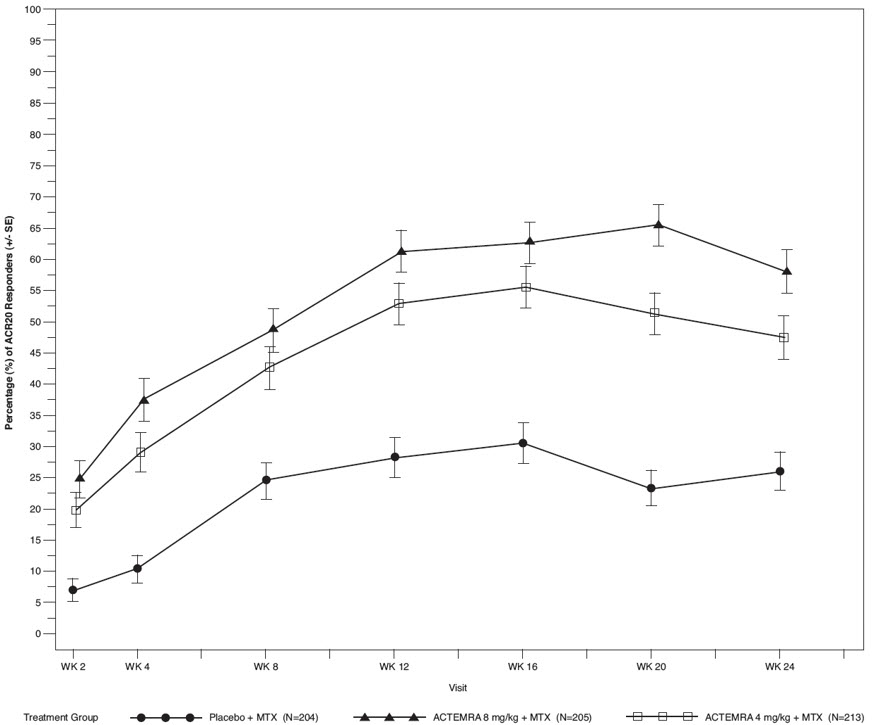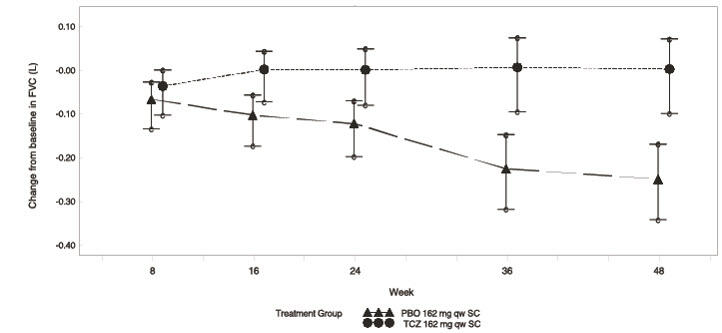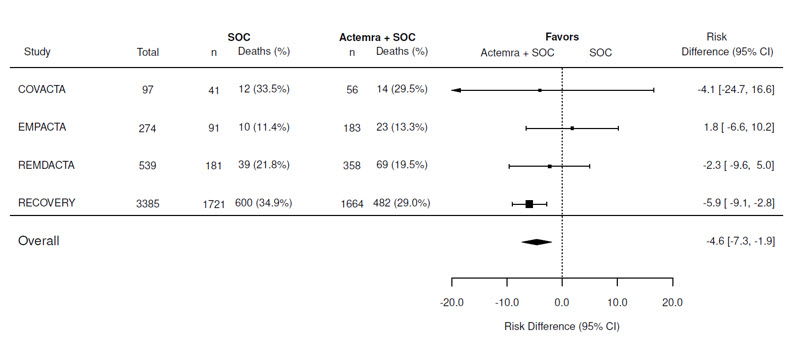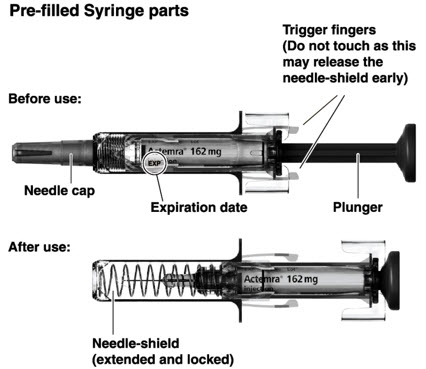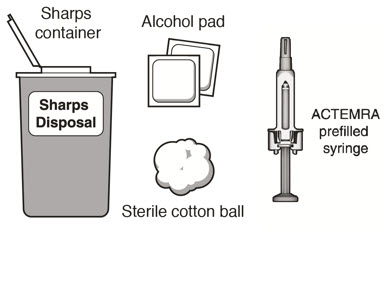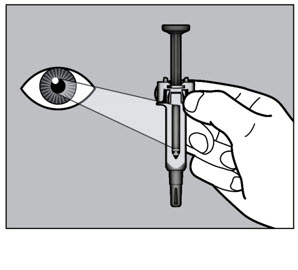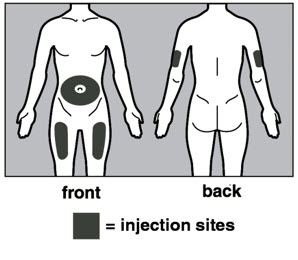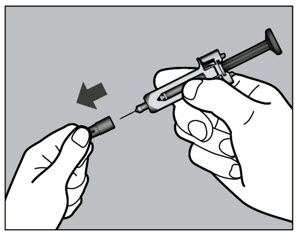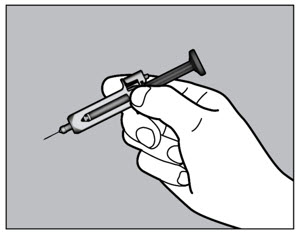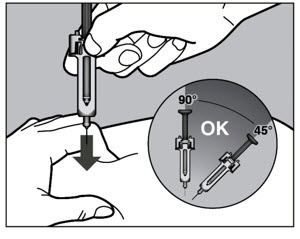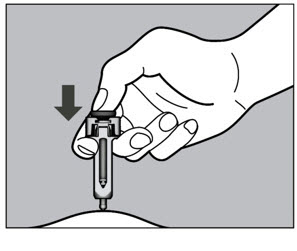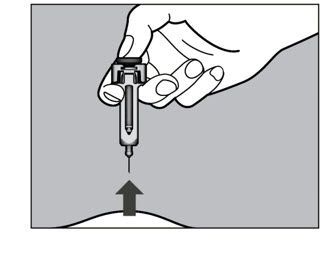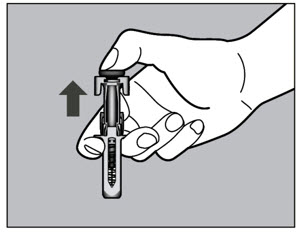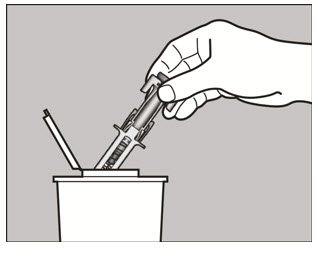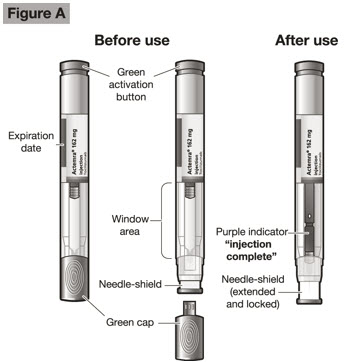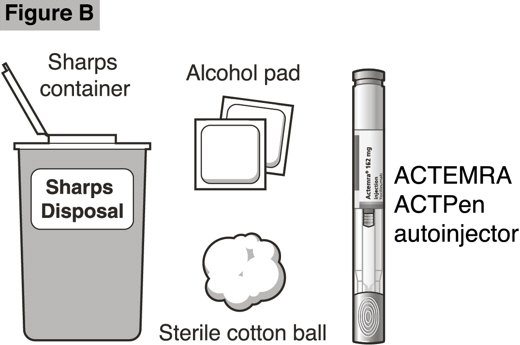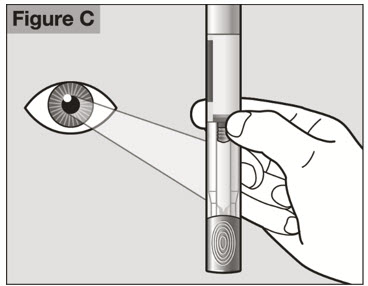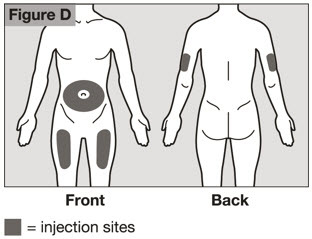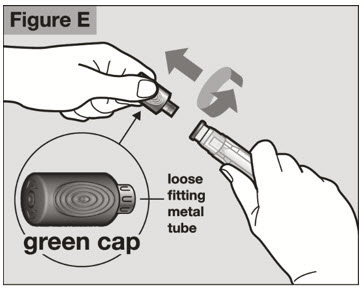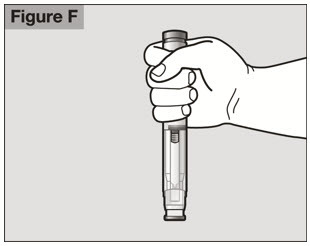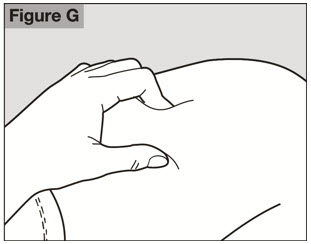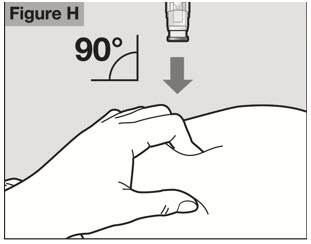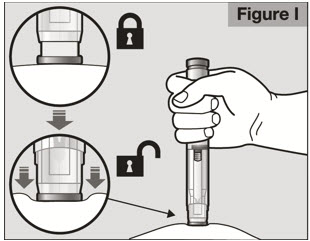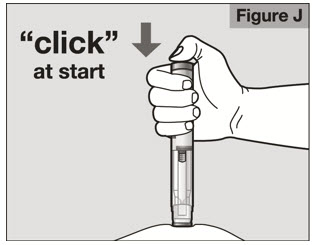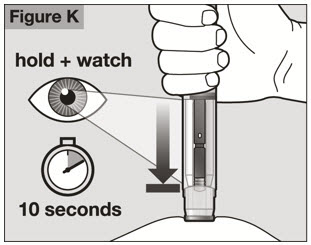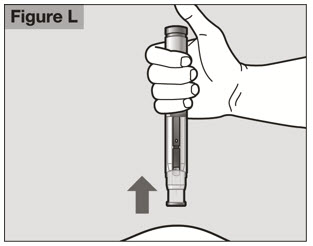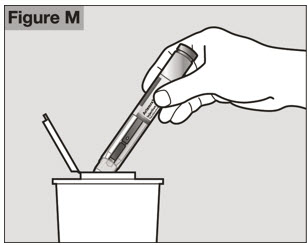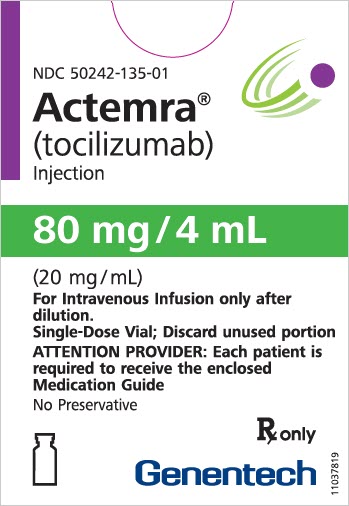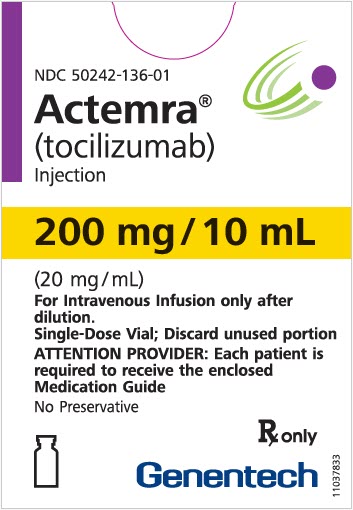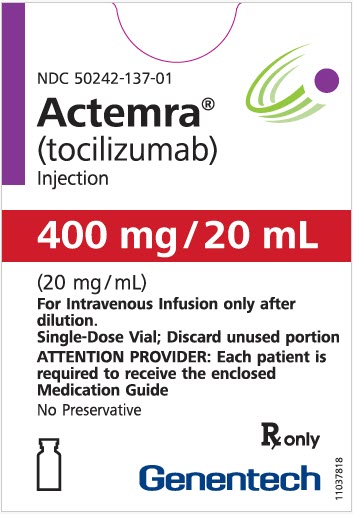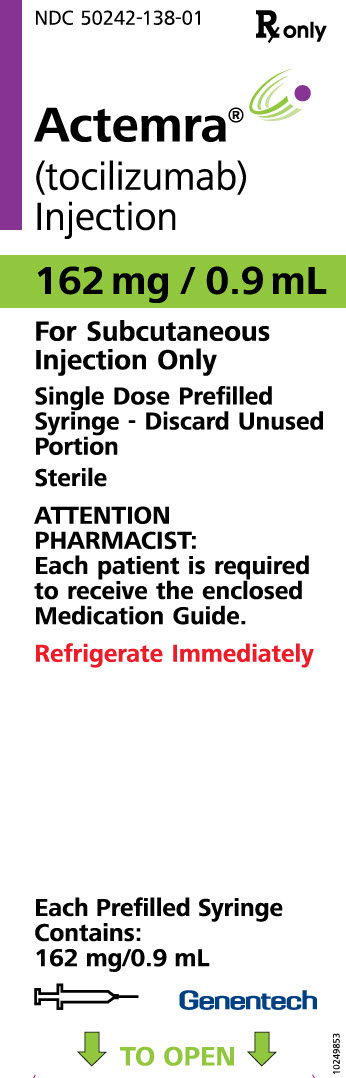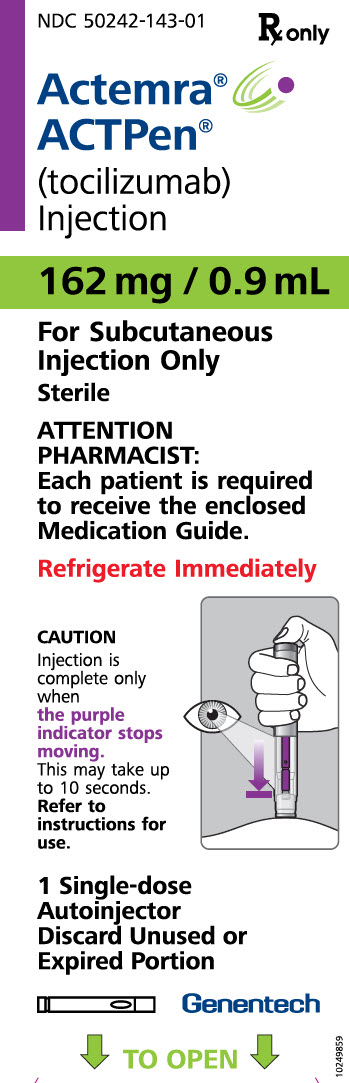 DRUG LABEL: ACTEMRA
NDC: 50242-135 | Form: INJECTION, SOLUTION, CONCENTRATE
Manufacturer: Genentech, Inc.
Category: prescription | Type: HUMAN PRESCRIPTION DRUG LABEL
Date: 20251216

ACTIVE INGREDIENTS: TOCILIZUMAB 80 mg/4 mL
INACTIVE INGREDIENTS: SUCROSE; POLYSORBATE 80; SODIUM PHOSPHATE, DIBASIC, DODECAHYDRATE; SODIUM PHOSPHATE, MONOBASIC, DIHYDRATE

HIGHLIGHTS OF PRESCRIBING INFORMATION

These highlights do not include all the information needed to use ACTEMRA safely and effectively. See full prescribing information for ACTEMRA.
ACTEMRA® (tocilizumab) injection, for intravenous or subcutaneous use
Initial U.S. Approval: 2010

WARNING: RISK OF SERIOUS INFECTIONS

See full prescribing information for complete boxed warning.

- Serious infections leading to hospitalization or death including tuberculosis (TB), bacterial, invasive fungal, viral, and other opportunistic infections have occurred in patients receiving ACTEMRA. (5.1)
- If a serious infection develops, interrupt ACTEMRA until the infection is controlled. (5.1)
- Perform test for latent TB (except patients with COVID-19); if positive, start treatment for TB prior to starting ACTEMRA. (5.1)
- Monitor all patients for active TB during treatment, even if initial latent TB test is negative. (5.1)

RECENT MAJOR CHANGES

Indications and Usage (1.7) | 08/2025
Dosage and Administration (2.8, 2.9) | 08/2025
Warnings and Precautions (5.2, 5.6) | 09/2024

1 INDICATIONS AND USAGE

ACTEMRA® (tocilizumab) is an interleukin-6 (IL-6) receptor antagonist indicated for treatment of:

Rheumatoid Arthritis (RA) (1.1)

- Adult patients with moderately to severely active rheumatoid arthritis who have had an inadequate response to one or more Disease-Modifying Anti-Rheumatic Drugs (DMARDs).

Giant Cell Arteritis (GCA) (1.2)

- Adult patients with giant cell arteritis.

Systemic Sclerosis-Associated Interstitial Lung Disease (SSc-ILD) (1.3)

- Slowing the rate of decline in pulmonary function in adult patients with systemic sclerosis-associated interstitial lung disease (SSc-ILD)

Polyarticular Juvenile Idiopathic Arthritis (PJIA) (1.4)

- Patients 2 years of age and older with active polyarticular juvenile idiopathic arthritis.

Systemic Juvenile Idiopathic Arthritis (SJIA) (1.5)

- Patients 2 years of age and older with active systemic juvenile idiopathic arthritis.

Cytokine Release Syndrome (CRS) (1.6)

- Adults and pediatric patients 2 years of age and older with chimeric antigen receptor (CAR) T cell-induced severe or life-threatening cytokine release syndrome.

Coronavirus Disease 2019 (COVID-19) (1.7)

- Hospitalized adult and pediatric patients aged 2 years and older with coronavirus disease 2019 (COVID-19) who are receiving systemic corticosteroids and require supplemental oxygen, non-invasive or invasive mechanical ventilation, or extracorporeal membrane oxygenation (ECMO).

2 DOSAGE AND ADMINISTRATION

For RA, pJIA and sJIA, ACTEMRA may be used alone or in combination with methotrexate: and in RA, other non-biologic DMARDs may be used. (2)

General Administration and Dosing Information (2.1)

- RA, GCA, SSc-ILD, PJIA and SJIA – It is recommended that ACTEMRA not be initiated in patients with an absolute neutrophil count (ANC) below 2000 per mm^3, platelet count below 100,000 per mm^3, or ALT or AST above 1.5 times the upper limit of normal (ULN)(5.3, 5.4).
- COVID-19 – It is recommended that ACTEMRA not be initiated in patients with an absolute neutrophil count (ANC) below 1000 per mm^3, platelet count below 50,000 mm^3, or ALT or AST above 10 times ULN (5.3, 5.4).
- In RA, CRS or COVID-19 patients, ACTEMRA doses exceeding 800 mg per infusion are not recommended. (2.2, 2.7, 12.3)
- In GCA patients, ACTEMRA doses exceeding 600 mg per infusion are not recommended. (2.3, 12.3)

Rheumatoid Arthritis (2.2)

Recommended Adult Intravenous Dosage:

When used in combination with non-biologic DMARDs or as monotherapy the recommended starting dose is 4 mg per kg every 4 weeks followed by an increase to 8 mg per kg every 4 weeks based on clinical response.

Recommended Adult Subcutaneous Dosage:

Patients less than 100 kg weight | 162 mg administered subcutaneously every other week, followed by an increase to every week based on clinical response
Patients at or above 100 kg weight | 162 mg administered subcutaneously every week

Giant Cell Arteritis (2.3)

Recommended Adult Intravenous Dosage:

The recommended dose is 6 mg per kg every 4 weeks in combination with a tapering course of glucocorticoids. ACTEMRA can be used alone following discontinuation of glucocorticoids.

Recommended Adult Subcutaneous Dosage:

The recommended dose is 162 mg given once every week as a subcutaneous injection, in combination with a tapering course of glucocorticoids.

A dose of 162 mg given once every other week as a subcutaneous injection, in combination with a tapering course of glucocorticoids, may be prescribed based on clinical considerations.

ACTEMRA can be used alone following discontinuation of glucocorticoids.

Systemic Sclerosis-Associated Interstitial Lung Disease (SSc-ILD) (2.4)

Recommended Adult Subcutaneous Dosage:

The recommended dose of ACTEMRA for adult patients with SSc-ILD is 162 mg given once every week as a subcutaneous injection.

Polyarticular Juvenile Idiopathic Arthritis (2.5)

Recommended Intravenous PJIA Dosage Every 4 Weeks
Patients less than 30 kg weight | 10 mg per kg
Patients at or above 30 kg weight | 8 mg per kg

Recommended Subcutaneous PJIA Dosage
Patients less than 30 kg weight | 162 mg once every three weeks
Patients at or above 30 kg weight | 162 mg once every two weeks

Systemic Juvenile Idiopathic Arthritis (2.6)

Recommended Intravenous SJIA Dosage Every 2 Weeks
Patients less than 30 kg weight | 12 mg per kg
Patients at or above 30 kg weight | 8 mg per kg

Recommended Subcutaneous SJIA Dosage
Patients less than 30 kg weight | 162 mg every two weeks
Patients at or above 30 kg weight | 162 mg every week

Cytokine Release Syndrome (2.7)

Recommended Intravenous CRS Dosage
Patients less than 30 kg weight | 12 mg per kg
Patients at or above 30 kg weight | 8 mg per kg
Alone or in combination with corticosteroids.

Coronavirus Disease 2019 (2.8)

Recommended Intravenous COVID-19 Dosage

Patients less than 30 kg weight

12 mg per kg

Patients at or above 30 kg weight

8 mg per kg

Administered by a 60-minute intravenous infusion

Administration of Intravenous formulation (2.9)

- For patients with RA, GCA, COVID-19, CRS, PJIA, and SJIA patients at or above 30 kg, dilute to 100 mL in 0.9% or 0.45% Sodium Chloride Injection, USP for intravenous infusion using aseptic technique.
- For PJIA, SJIA, CRS and COVID-19 patients less than 30 kg, dilute to 50 mL in 0.9% or 0.45% Sodium Chloride Injection, USP for intravenous infusion using aseptic technique.
- Administer as a single intravenous drip infusion over 1 hour; do not administer as bolus or push.

Administration of Subcutaneous formulation (2.10)

- Follow the Instructions for Use for prefilled syringe and prefilled ACTPen® autoinjector

Dose Modifications (2.11)

- Recommended for management of certain dose-related laboratory changes including elevated liver enzymes, neutropenia, and thrombocytopenia.

3 DOSAGE FORMS AND STRENGTHS

Intravenous Infusion

Injection: 80 mg/4 mL (20 mg/mL), 200 mg/10 mL (20 mg/mL), 400 mg/20 mL (20 mg/mL) in single-dose vials for further dilution prior to intravenous infusion (3)

Subcutaneous Injection

Injection: 162 mg/0.9 mL in a single-dose prefilled syringe or single-dose prefilled ACTPen® autoinjector (3)

4 CONTRAINDICATIONS

Known hypersensitivity to ACTEMRA. (4)

5 WARNINGS AND PRECAUTIONS

- Serious Infections – do not administer ACTEMRA during an active infection, including localized infections. If a serious infection develops, interrupt ACTEMRA until the infection is controlled. (5.1)
- Gastrointestinal (GI) perforation—use with caution in patients who may be at increased risk. (5.2)
- Hepatotoxicity- Monitor patients for signs and symptoms of hepatic injury. Modify or discontinue ACTEMRA if abnormal liver tests persist or worsen or if clinical signs and symptoms of liver disease develop. (2.10, 5.3)
- Laboratory monitoring—recommended due to potential consequences of treatment-related changes in neutrophils, platelets, lipids, and liver function tests. (2.10, 5.4)
- Hypersensitivity reactions, including anaphylaxis and death, and serious cutaneous reactions including Drug Reaction with Eosinophilia and Systemic Symptoms (DRESS) – discontinue ACTEMRA, treat promptly, and monitor until reaction resolves. (5.6)
- Live vaccines—Avoid use with ACTEMRA. (5.9, 7.3)

6 ADVERSE REACTIONS

Most common adverse reactions (incidence of at least 5%): upper respiratory tract infections, nasopharyngitis, headache, hypertension, increased ALT, injection site reactions. (6)

To report SUSPECTED ADVERSE REACTIONS, contact Genentech at 1-888-835-2555 or FDA at 1-800-FDA-1088 or www.fda.gov/medwatch

8 USE IN SPECIFIC POPULATIONS

- Pregnancy: Based on animal data, may cause fetal harm. (8.1)
- Lactation: Discontinue drug or nursing taking into consideration importance of drug to mother. (8.2)

FULL PRESCRIBING INFORMATION

WARNING: RISK OF SERIOUS INFECTIONS

Patients treated with ACTEMRA are at increased risk for developing serious infections that may lead to hospitalization or death [see Warnings and Precautions (5.1), Adverse Reactions (6.1)]. Most patients who developed these infections were taking concomitant immunosuppressants such as methotrexate or corticosteroids.

If a serious infection develops, interrupt ACTEMRA until the infection is controlled.

Reported infections include:

- Active tuberculosis, which may present with pulmonary or extrapulmonary disease. Patients, except those with COVID-19, should be tested for latent tuberculosis before ACTEMRA use and during therapy. Treatment for latent infection should be initiated prior to ACTEMRA use.
- Invasive fungal infections, including candidiasis, aspergillosis, and pneumocystis. Patients with invasive fungal infections may present with disseminated, rather than localized, disease.
- Bacterial, viral and other infections due to opportunistic pathogens.

The risks and benefits of treatment with ACTEMRA should be carefully considered prior to initiating therapy in patients with chronic or recurrent infection.

Patients should be closely monitored for the development of signs and symptoms of infection during and after treatment with ACTEMRA, including the possible development of tuberculosis in patients who tested negative for latent tuberculosis infection prior to initiating therapy [see Warnings and Precautions (5.1)].

1 INDICATIONS AND USAGE

1.1 Rheumatoid Arthritis (RA)

ACTEMRA® (tocilizumab) is indicated for the treatment of adult patients with moderately to severely active rheumatoid arthritis who have had an inadequate response to one or more Disease-Modifying Anti-Rheumatic Drugs (DMARDs).

1.2 Giant Cell Arteritis (GCA)

ACTEMRA® (tocilizumab) is indicated for the treatment of giant cell arteritis (GCA) in adult patients.

1.3 Systemic Sclerosis-Associated Interstitial Lung Disease (SSc-ILD)

ACTEMRA® (tocilizumab) is indicated for slowing the rate of decline in pulmonary function in adult patients with systemic sclerosis-associated interstitial lung disease.

1.4 Polyarticular Juvenile Idiopathic Arthritis (PJIA)

ACTEMRA® (tocilizumab) is indicated for the treatment of active polyarticular juvenile idiopathic arthritis in patients 2 years of age and older.

1.5 Systemic Juvenile Idiopathic Arthritis (SJIA)

ACTEMRA® (tocilizumab) is indicated for the treatment of active systemic juvenile idiopathic arthritis in patients 2 years of age and older.

1.6 Cytokine Release Syndrome (CRS)

ACTEMRA® (tocilizumab) is indicated for the treatment of chimeric antigen receptor (CAR) T cell-induced severe or life-threatening cytokine release syndrome in adults and pediatric patients 2 years of age and older.

1.7 Coronavirus Disease 2019 (COVID-19)

ACTEMRA® (tocilizumab) is indicated for the treatment of coronavirus disease 2019 (COVID-19) in hospitalized adult and pediatric patients aged 2 years and older who are receiving systemic corticosteroids and require supplemental oxygen, non-invasive or invasive mechanical ventilation, or extracorporeal membrane oxygenation (ECMO).

2 DOSAGE AND ADMINISTRATION

2.1 General Considerations for Administration

Not Recommended for Concomitant Use with Biological DMARDs

ACTEMRA has not been studied in combination with biological DMARDs such as TNF antagonists, IL-1R antagonists, anti-CD20 monoclonal antibodies and selective co-stimulation modulators because of the possibility of increased immunosuppression and increased risk of infection. Avoid using ACTEMRA with biological DMARDs.

Baseline Laboratory Evaluation Prior to Treatment

Obtain and assess baseline complete blood count (CBC) and liver function tests prior to treatment.

- RA, GCA, SSc-ILD, PJIA and SJIA – It is recommended that ACTEMRA not be initiated in patients with an absolute neutrophil count (ANC) below 2000 per mm^3, platelet count below 100,000 per mm^3, or ALT or AST above 1.5 times the upper limit of normal (ULN) [see Warnings and Precautions (5.3, 5.4)].
- CRS – Patients with severe or life-threatening CRS frequently have cytopenias or elevated ALT or AST due to the lymphodepleting chemotherapy or the CRS. The decision to administer ACTEMRA should take into account the potential benefit of treating the CRS versus the risks of short-term treatment with ACTEMRA.
- COVID-19 – It is recommended that ACTEMRA not be initiated in patients with an absolute neutrophil count (ANC) below 1000 per mm^3, platelet count below 50,000 mm^3, or ALT or AST above 10 times ULN [see Warnings and Precautions (5.3, 5.4)].

2.2 Recommended Dosage for Rheumatoid Arthritis

ACTEMRA may be used as monotherapy or concomitantly with methotrexate or other non-biologic DMARDs as an intravenous infusion or as a subcutaneous injection.

Recommended Intravenous Dosage Regimen:

The recommended dosage of ACTEMRA for adult patients given as a 60-minute single intravenous drip infusion is 4 mg per kg every 4 weeks followed by an increase to 8 mg per kg every 4 weeks based on clinical response.

- Reduction of dose from 8 mg per kg to 4 mg per kg is recommended for management of certain dose-related laboratory changes including elevated liver enzymes, neutropenia, and thrombocytopenia [see Dosage and Administration (2.11), Warnings and Precautions (5.3, 5.4), and Adverse Reactions (6.1)].
- Doses exceeding 800 mg per infusion are not recommended in RA patients [see Clinical Pharmacology (12.3)].

Recommended Subcutaneous Dosage Regimen:

Patients less than 100 kg weight | 162 mg administered subcutaneously every other week, followed by an increase to every week based on clinical response
Patients at or above 100 kg weight | 162 mg administered subcutaneously every week

When transitioning from ACTEMRA intravenous therapy to subcutaneous administration administer the first subcutaneous dose instead of the next scheduled intravenous dose.

Interruption of dose or reduction in frequency of administration of subcutaneous dose from every week to every other week dosing is recommended for management of certain dose-related laboratory changes including elevated liver enzymes, neutropenia, and thrombocytopenia [see Dosage and Administration (2.11), Warnings and Precautions (5.3, 5.4), and Adverse Reactions (6.2)].

2.3 Recommended Dosage for Giant Cell Arteritis

Recommended Intravenous Dosage Regimen:

The recommended dosage of ACTEMRA for adult patients given as a 60-minute single intravenous drip infusion is 6 mg per kg every 4 weeks in combination with tapering course of glucocorticoids.

ACTEMRA can be used alone following discontinuation of glucocorticoids.

- Interruption of dosing may be needed for management of dose-related laboratory abnormalities including elevated liver enzymes, neutropenia, and thrombocytopenia [see Dosage and Administration (2.11)].
- Doses exceeding 600 mg per infusion are not recommended in GCA patients [see Clinical Pharmacology (12.3)].

Recommended Subcutaneous Dosage Regimen:

The recommended dose of ACTEMRA for adult patients with GCA is 162 mg given once every week as a subcutaneous injection in combination with a tapering course of glucocorticoids.

A dose of 162 mg given once every other week as a subcutaneous injection in combination with a tapering course of glucocorticoids may be prescribed based on clinical considerations.

ACTEMRA can be used alone following discontinuation of glucocorticoids.

When transitioning from ACTEMRA intravenous therapy to subcutaneous administration, administer the first subcutaneous dose instead of the next scheduled intravenous dose.

Interruption of dose or reduction in frequency of administration of subcutaneous dose from every week to every other week dosing may be needed for management of dose-related laboratory abnormalities including elevated liver enzymes, neutropenia, and thrombocytopenia [see Dosage and Administration (2.11)].

2.4 Recommended Dosage for Systemic Sclerosis-Associated Interstitial Lung Disease

The recommended dose of ACTEMRA for adult patients with SSc-ILD is 162 mg given once every week as a subcutaneous injection.

- Interruption of dosing may be needed for management of dose-related laboratory abnormalities including elevated liver enzymes, neutropenia, and thrombocytopenia [see Dosage and Administration (2.11)].
- Subcutaneous administration with the prefilled ACTPen® autoinjector has not been studied in SSc-ILD.
- Intravenous administration is not approved for SSc-ILD.

2.5 Recommended Dosage for Polyarticular Juvenile Idiopathic Arthritis

ACTEMRA may be used as an intravenous infusion or as a subcutaneous injection alone or in combination with methotrexate. Do not change dose based solely on a single visit body weight measurement, as weight may fluctuate.

Recommended Intravenous Dosage Regimen:

The recommended dosage of ACTEMRA for PJIA patients given once every 4 weeks as a 60-minute single intravenous drip infusion is:

Recommended Intravenous PJIA Dosage Every 4 Weeks
Patients less than 30 kg weight | 10 mg per kg
Patients at or above 30 kg weight | 8 mg per kg

Recommended Subcutaneous Dosage Regimen:

Recommended Subcutaneous PJIA Dosage
Patients less than 30 kg weight | 162 mg once every 3 weeks
Patients at or above 30 kg weight | 162 mg once every 2 weeks

When transitioning from ACTEMRA intravenous therapy to subcutaneous administration, administer the first subcutaneous dose instead of the next scheduled intravenous dose.

Interruption of dosing may be needed for management of dose-related laboratory abnormalities including elevated liver enzymes, neutropenia, and thrombocytopenia [see Dosage and Administration (2.11].

2.6 Recommended Dosage for Systemic Juvenile Idiopathic Arthritis

ACTEMRA may be used as an intravenous infusion or as a subcutaneous injection alone or in combination with methotrexate. Do not change a dose based solely on a single visit body weight measurement, as weight may fluctuate.

Recommended Intravenous Dosage Regimen:

The recommended dose of ACTEMRA for SJIA patients given once every 2 weeks as a 60-minute single intravenous drip infusion is:

Recommended Intravenous SJIA Dosage Every 2 Weeks
Patients less than 30 kg weight | 12 mg per kg
Patients at or above 30 kg weight | 8 mg per kg

Recommended Subcutaneous Dosage Regimen:

Recommended Subcutaneous SJIA Dosage
Patients less than 30 kg weight | 162 mg once every two weeks
Patients at or above 30 kg weight | 162 mg once every week

When transitioning from ACTEMRA intravenous therapy to subcutaneous administration, administer the first subcutaneous dose when the next scheduled intravenous dose is due.

Interruption of dosing may be needed for management of dose-related laboratory abnormalities including elevated liver enzymes, neutropenia, and thrombocytopenia [see Dosage and Administration (2.11)].

2.7 Recommended Dosage for Cytokine Release Syndrome (CRS)

Use only the intravenous route for treatment of CRS. The recommended dose of ACTEMRA for treatment of CRS given as a 60-minute intravenous infusion is:

Recommended Intravenous CRS Dosage
Patients less than 30 kg weight | 12 mg per kg
Patients at or above 30 kg weight | 8 mg per kg
Alone or in combination with corticosteroids

- If no clinical improvement in the signs and symptoms of CRS occurs after the first dose, up to 3 additional doses of ACTEMRA may be administered. The interval between consecutive doses should be at least 8 hours.
- Doses exceeding 800 mg per infusion are not recommended in CRS patients.
- Subcutaneous administration is not approved for CRS.

2.8 Recommended Dosage for Coronavirus Disease 2019 (COVID-19)

Administer ACTEMRA by intravenous infusion only.

The recommended dosage of ACTEMRA for treatment of patients with COVID-19 given as a single 60-minute intravenous infusion is:

Recommended Intravenous COVID-19 Dosage
Patients less than 30 kg weight | 12 mg per kg
Patients at or above 30 kg weight | 8 mg per kg

If clinical signs or symptoms worsen or do not improve after the first dose, one additional infusion of ACTEMRA may be administered at least 8 hours after the initial infusion.

- Doses exceeding 800 mg per infusion are not recommended in patients with COVID-19.
- Subcutaneous administration is not approved for COVID-19.

2.9 Preparation and Administration Instructions for Intravenous Infusion

ACTEMRA for intravenous infusion should be diluted by a healthcare professional using aseptic technique as follows:

- Use a sterile needle and syringe to prepare ACTEMRA.
- Patients less than 30 kg: use a 50 mL infusion bag or bottle of 0.9% or 0.45% Sodium Chloride Injection, USP, and then follow steps 1 and 2 below.
- Patients at or above 30 kg weight: use a 100 mL infusion bag or bottle, and then follow steps 1 and 2 below.
- Step 1. Withdraw a volume of 0.9% or 0.45% Sodium Chloride Injection, USP, equal to the volume of the ACTEMRA injection required for the patient's dose from the infusion bag or bottle [see Dosage and Administration (2.2, 2.5, 2.6, 2.7)].

For Intravenous Use: Volume of ACTEMRA Injection per kg of Body Weight
Dosage | Indication | Volume of ACTEMRA injection per kg of body weight
4 mg/kg | Adult RA | 0.2 mL/kg
6 mg/kg | Adult GCA | 0.3 mL/kg
8 mg/kg | Adult RA SJIA, PJIA, CRS and COVID-19 (greater than or equal to 30 kg of body weight) | 0.4 mL/kg
10 mg/kg | PJIA (less than 30 kg of body weight) | 0.5 mL/kg
12 mg/kg | SJIA, CRS and COVID-19 (less than 30 kg of body weight) | 0.6 mL/kg

- Step 2. Withdraw the amount of ACTEMRA for intravenous infusion from the vial(s) and add slowly into the 0.9% or 0.45% Sodium Chloride Injection, USP infusion bag or bottle. To mix the solution, gently invert the bag to avoid foaming.
- The fully diluted ACTEMRA solutions for infusion using 0.9% Sodium Chloride Injection, USP may be stored at 36°F to 46°F (2°C to 8°C) or room temperature for up to 24 hours and should be protected from light.
- The fully diluted ACTEMRA solutions for infusion using 0.45% Sodium Chloride Injection, USP may be stored at 36°F to 46°F (2°C to 8°C) for up to 24 hours or room temperature for up to 4 hours and should be protected from light.
- ACTEMRA solutions do not contain preservatives; therefore, unused product remaining in the vials should not be used.
- Allow the fully diluted ACTEMRA solution to reach room temperature prior to infusion.
- The infusion should be administered over 60 minutes, and must be administered with an infusion set. Do not administer as an intravenous push or bolus.
- ACTEMRA should not be infused concomitantly in the same intravenous line with other drugs. No physical or biochemical compatibility studies have been conducted to evaluate the co-administration of ACTEMRA with other drugs.
- Parenteral drug products should be inspected visually for particulate matter and discoloration prior to administration, whenever solution and container permit. If particulates and discolorations are noted, the product should not be used.
- Fully diluted ACTEMRA solutions are compatible with polypropylene, polyethylene and polyvinyl chloride infusion bags and polypropylene, polyethylene and glass infusion bottles.

2.10 Preparation and Administration Instructions for Subcutaneous Injection

- ACTEMRA for subcutaneous injection is not intended for intravenous drip infusion.
- Assess suitability of patient for subcutaneous home use and instruct patients to inform a healthcare professional before administering the next dose if they experience any symptoms of allergic reaction. Patients should seek immediate medical attention if they develop symptoms of serious allergic reactions. ACTEMRA subcutaneous injection is intended for use under the guidance of a healthcare practitioner. After proper training in subcutaneous injection technique, a patient may self-inject ACTEMRA or the patient's caregiver may administer ACTEMRA if a healthcare practitioner determines that it is appropriate. PJIA and SJIA patients may self-inject with the ACTEMRA prefilled syringe or ACTPen® autoinjector, or the patient's caregiver may administer ACTEMRA if both the healthcare practitioner and the parent/legal guardian determines it is appropriate [see Use in Specific Populations (8.4)]. Patients, or patient caregivers, should be instructed to follow the directions provided in the Instructions for Use (IFU) for additional details on medication administration.
- Parenteral drug products should be inspected visually for particulate matter and discoloration prior to administration. Do not use ACTEMRA prefilled syringes (PFS) or prefilled ACTPen® autoinjectors exhibiting particulate matter, cloudiness, or discoloration. ACTEMRA for subcutaneous administration should be clear and colorless to pale yellow. Do not use if any part of the PFS or ACTPen® autoinjector appears to be damaged.
- Patients using ACTEMRA for subcutaneous administration should be instructed to inject the full amount in the syringe (0.9 mL) or full amount in the ACTPen® autoinjector (0.9 mL), which provides 162 mg of ACTEMRA, according to the directions provided in the IFU.
- Injection sites should be rotated with each injection and should never be given into moles, scars, or areas where the skin is tender, bruised, red, hard, or not intact.

2.11 Dosage Modifications due to Serious Infections or Laboratory Abnormalities

Serious Infections

Hold ACTEMRA treatment if a patient develops a serious infection until the infection is controlled.

Laboratory Abnormalities

Rheumatoid Arthritis, Giant Cell Arteritis and Systemic Sclerosis-Associated Interstitial Lung Disease

Liver Enzyme Abnormalities [see Warnings and Precautions (5.3,5.4)]
Lab Value | Recommendation for RA and SSc-ILD | Recommendation for GCA
Greater than 1 to 3× ULN | Dose modify concomitant DMARDs if appropriate For persistent increases in this range:; - For patients receiving intravenous ACTEMRA, reduce dose to 4 mg per kg or hold ACTEMRA until ALT or AST have normalized - For patients receiving subcutaneous ACTEMRA, reduce injection frequency to every other week or hold dosing until ALT or AST have normalized. Resume ACTEMRA at every other week and increase frequency to every week as clinically appropriate. | Dose modify immunomodulatory agents if appropriate For persistent increases in this range:; - For patients receiving intravenous ACTEMRA, hold ACTEMRA until ALT or AST have normalized - For patients receiving subcutaneous ACTEMRA, reduce injection frequency to every other week or hold dosing until ALT or AST have normalized. Resume ACTEMRA at every other week and increase frequency to every week as clinically appropriate
Greater than 3 to 5× ULN (confirmed by repeat testing) | Hold ACTEMRA dosing until less than 3× ULN and follow recommendations above for greater than 1 to 3× ULN For persistent increases greater than 3× ULN, discontinue ACTEMRA | Hold ACTEMRA dosing until less than 3x ULN and follow recommendations above for greater than 1 to 3x ULN For persistent increases greater than 3x ULN, discontinue ACTEMRA
Greater than 5× ULN | Discontinue ACTEMRA | Discontinue ACTEMRA

Low Absolute Neutrophil Count (ANC) [see Warnings and Precautions (5.4)]
Lab Value (cells per mm^3) | Recommendation for RA and SSc-ILD | Recommendation for GCA
ANC greater than 1000 | Maintain dose | Maintain dose
ANC 500 to 1000 | Hold ACTEMRA dosing When ANC greater than 1000 cells per mm^3:; - For patients receiving intravenous ACTEMRA, resume ACTEMRA at 4 mg per kg and increase to 8 mg per kg as clinically appropriate - For patients receiving subcutaneous ACTEMRA, resume ACTEMRA at every other week and increase frequency to every week as clinically appropriate | Hold ACTEMRA dosing When ANC greater than 1000 cells per mm^3:; - For patients receiving intravenous ACTEMRA, resume ACTEMRA at 6 mg per kg - For patients receiving subcutaneous ACTEMRA, resume ACTEMRA at every other week and increase frequency to every week as clinically appropriate
ANC less than 500 | Discontinue ACTEMRA | Discontinue ACTEMRA

Low Platelet Count [see Warnings and Precautions (5.4)]
Lab Value (cells per mm^3) | Recommendation for RA and SSc-ILD | Recommendation for GCA
50,000 to 100,000 | Hold ACTEMRA dosing When platelet count is greater than 100,000 cells per mm^3:; - For patients receiving intravenous ACTEMRA, resume ACTEMRA at 4 mg per kg and increase to 8 mg per kg as clinically appropriate - For patients receiving subcutaneous ACTEMRA, resume ACTEMRA at every other week and increase frequency to every week as clinically appropriate | Hold ACTEMRA dosing When platelet count is greater than 100,000 cells per mm^3:; - For patients receiving intravenous ACTEMRA, resume ACTEMRA at 6 mg per kg - For patients receiving subcutaneous ACTEMRA, resume ACTEMRA at every other week and increase frequency to every week as clinically appropriate
Less than 50,000 | Discontinue ACTEMRA | Discontinue ACTEMRA

Polyarticular and Systemic Juvenile Idiopathic Arthritis

Dose reduction of ACTEMRA has not been studied in the PJIA and SJIA populations. Dose interruptions of ACTEMRA are recommended for liver enzyme abnormalities, low neutrophil counts, and low platelet counts in patients with PJIA and SJIA at levels similar to what is outlined above for patients with RA and GCA. If appropriate, dose modify or stop concomitant methotrexate and/or other medications and hold ACTEMRA dosing until the clinical situation has been evaluated. In PJIA and SJIA the decision to discontinue ACTEMRA for a laboratory abnormality should be based upon the medical assessment of the individual patient.

3 DOSAGE FORMS AND STRENGTHS

Intravenous Infusion

Injection: 80 mg/4 mL, 200 mg/10 mL, 400 mg/20 mL as a clear, colorless to pale yellow solution in 20 mg/mL single-dose vials for further dilution prior to intravenous infusion.

Subcutaneous Injection

Injection: 162 mg/0.9 mL clear, colorless to slightly yellowish solution in a single-dose prefilled syringe or single-dose prefilled ACTPen® autoinjector.

4 CONTRAINDICATIONS

ACTEMRA is contraindicated in patients with known hypersensitivity to ACTEMRA [see Warnings and Precautions (5.6)].

5 WARNINGS AND PRECAUTIONS

5.1 Serious Infections

Serious and sometimes fatal infections due to bacterial, mycobacterial, invasive fungal, viral, protozoal, or other opportunistic pathogens have been reported in patients receiving immunosuppressive agents including ACTEMRA. The most common serious infections included pneumonia, urinary tract infection, cellulitis, herpes zoster, gastroenteritis, diverticulitis, sepsis and bacterial arthritis [see Adverse Reactions (6.1)]. Among opportunistic infections, tuberculosis, cryptococcus, aspergillosis, candidiasis, and pneumocystosis were reported with ACTEMRA. Other serious infections, not reported in clinical studies, may also occur (e.g., histoplasmosis, coccidioidomycosis, listeriosis). Patients have presented with disseminated rather than localized disease, and were often taking concomitant immunosuppressants such as methotrexate or corticosteroids which in addition to rheumatoid arthritis may predispose them to infections.

Do not administer ACTEMRA in patients with an active infection, including localized infections. The risks and benefits of treatment should be considered prior to initiating ACTEMRA in patients:

- with chronic or recurrent infection;
- who have been exposed to tuberculosis;
- with a history of serious or an opportunistic infection;
- who have resided or traveled in areas of endemic tuberculosis or endemic mycoses; or
- with underlying conditions that may predispose them to infection.

Closely monitor patients for the development of signs and symptoms of infection during and after treatment with ACTEMRA, as signs and symptoms of acute inflammation may be lessened due to suppression of the acute phase reactants [see Dosage and Administration (2.8), Adverse Reactions (6.1), and Patient Counseling Information (17)].

Hold ACTEMRA if a patient develops a serious infection, an opportunistic infection, or sepsis. A patient who develops a new infection during treatment with ACTEMRA should undergo a prompt and complete diagnostic workup appropriate for an immunocompromised patient, initiate appropriate antimicrobial therapy, and closely monitor the patient.

COVID-19

In patients with COVID-19, monitor for signs and symptoms of new infections during and after treatment with ACTEMRA. There is limited information regarding the use of ACTEMRA in patients with COVID-19 and concomitant active serious infections. The risks and benefits of treatment with ACTEMRA in COVID-19 patients with other concurrent infections should be considered.

Tuberculosis

Evaluate patients for tuberculosis risk factors and test for latent infection prior to initiating ACTEMRA. In patients with COVID-19, testing for latent infection is not necessary prior to initiating treatment with ACTEMRA.

Consider anti-tuberculosis therapy prior to initiation of ACTEMRA in patients with a past history of latent or active tuberculosis in whom an adequate course of treatment cannot be confirmed, and for patients with a negative test for latent tuberculosis but having risk factors for tuberculosis infection. Consultation with a physician with expertise in the treatment of tuberculosis is recommended to aid in the decision whether initiating anti-tuberculosis therapy is appropriate for an individual patient.

Closely monitor patients for the development of signs and symptoms of tuberculosis including patients who tested negative for latent tuberculosis infection prior to initiating therapy.

The incidence of tuberculosis in worldwide clinical development programs is 0.1%. Patients with latent tuberculosis should be treated with standard antimycobacterial therapy before initiating ACTEMRA.

Viral Reactivation

Viral reactivation has been reported with immunosuppressive biologic therapies and cases of herpes zoster exacerbation were observed in clinical studies with ACTEMRA. No cases of Hepatitis B reactivation were observed in the trials; however patients who screened positive for hepatitis were excluded.

5.2 Gastrointestinal Perforations

Events of gastrointestinal perforation have been reported in clinical trials, primarily as complications of diverticulitis in patients treated with ACTEMRA. Use ACTEMRA with caution in patients who may be at increased risk for gastrointestinal perforation. Promptly evaluate patients presenting with fever, new onset abdominal symptoms, and a change in bowel habits for early identification of gastrointestinal perforation [see Adverse Reactions (6.1)].

5.3 Hepatotoxicity

Serious cases of hepatic injury have been observed in patients taking intravenous or subcutaneous ACTEMRA. Some of these cases have resulted in liver transplant or death. Time to onset for cases ranged from months to years after treatment initiation with tocilizumab. While most cases presented with marked elevations of transaminases (> 5 times ULN), some cases presented with signs or symptoms of liver dysfunction and only mildly elevated transaminases.

During randomized controlled studies, treatment with ACTEMRA was associated with a higher incidence of transaminase elevations [see Adverse Reactions (6.1, 6.2, 6.6, 6.8)]. Increased frequency and magnitude of these elevations was observed when potentially hepatotoxic drugs (e.g., MTX) were used in combination with ACTEMRA.

For RA, GCA and SSc-ILD patients, obtain a liver test panel (serum alanine aminotransferase [ALT], aspartate aminotransferase [AST], alkaline phosphatase, and total bilirubin) before initiating ACTEMRA, every 4 to 8 weeks after start of therapy for the first 6 months of treatment and every 3 months thereafter. It is not recommended to initiate ACTEMRA treatment in RA, GCA or SSc-ILD patients with elevated transaminases ALT or AST greater than 1.5× ULN. In patients who develop elevated ALT or AST greater than 5× ULN, discontinue ACTEMRA. For recommended modifications based upon increase in transaminases see Dosage and Administration (2.11).

Patients hospitalized with COVID-19 may have elevated ALT or AST levels. Multi-organ failure with involvement of the liver is recognized as a complication of severe COVID-19. The decision to administer ACTEMRA should balance the potential benefit of treating COVID-19 against the potential risks of acute treatment with ACTEMRA. It is not recommended to initiate ACTEMRA treatment in COVID-19 patients with elevated ALT or AST above 10 × ULN. Monitor ALT and AST during treatment.

Measure liver tests promptly in patients who report symptoms that may indicate liver injury, such as fatigue, anorexia, right upper abdominal discomfort, dark urine or jaundice. In this clinical context, if the patient is found to have abnormal liver tests (e.g., ALT greater than three times the upper limit of the reference range, serum total bilirubin greater than two times the upper limit of the reference range), ACTEMRA treatment should be interrupted and investigation done to establish the probable cause. ACTEMRA should only be restarted in patients with another explanation for the liver test abnormalities after normalization of the liver tests.

A similar pattern of liver enzyme elevation is noted with ACTEMRA treatment in the PJIA and SJIA populations. Monitor liver test panel at the time of the second administration and thereafter every 4 to 8 weeks for PJIA and every 2 to 4 weeks for SJIA.

5.4 Changes in Laboratory Parameters

Patients with Rheumatoid Arthritis, Giant Cell Arteritis, Systemic Sclerosis-Associated Interstitial Lung Disease and Coronavirus Disease 2019

Neutropenia

Treatment with ACTEMRA was associated with a higher incidence of neutropenia. Infections have been uncommonly reported in association with treatment-related neutropenia in long-term extension studies and postmarketing clinical experience.

- It is not recommended to initiate ACTEMRA treatment in RA, GCA and SSc-ILD patients with a low neutrophil count, i.e., absolute neutrophil count (ANC) less than 2000 per mm^3. In patients who develop an absolute neutrophil count less than 500 per mm^3 treatment is not recommended.
- Monitor neutrophils 4 to 8 weeks after start of therapy and every 3 months thereafter [see Clinical Pharmacology (12.2)]. For recommended modifications based on ANC results see Dosage and Administration (2.11).
- It is not recommended to initiate ACTEMRA treatment in COVID-19 patients with an ANC less than 1000 per mm^3. Neutrophils should be monitored.

Thrombocytopenia

Treatment with ACTEMRA was associated with a reduction in platelet counts. Treatment-related reduction in platelets was not associated with serious bleeding events in clinical trials [see Adverse Reactions (6.1, 6.2)].

- It is not recommended to initiate ACTEMRA treatment in RA, GCA and SSc-ILD patients with a platelet count below 100,000 per mm^3. In patients who develop a platelet count less than 50,000 per mm^3 treatment is not recommended.
- Monitor platelets 4 to 8 weeks after start of therapy and every 3 months thereafter. For recommended modifications based on platelet counts see Dosage and Administration (2.11).
- In COVID-19 patients with a platelet count less than 50,000 per mm^3, treatment is not recommended. Platelets should be monitored.

Elevated Liver Enzymes

Refer to 5.3 Hepatotoxicity. For recommended modifications [see Dosage and Administration (2.11)]

Lipid Abnormalities

Treatment with ACTEMRA was associated with increases in lipid parameters such as total cholesterol, triglycerides, LDL cholesterol, and/or HDL cholesterol [see Adverse Reactions (6.1, 6.2)].

- Assess lipid parameters approximately 4 to 8 weeks following initiation of ACTEMRA therapy.
- Subsequently, manage patients according to clinical guidelines [e.g., National Cholesterol Educational Program (NCEP)] for the management of hyperlipidemia.

Patients with Polyarticular and Systemic Juvenile Idiopathic Arthritis

A similar pattern of liver enzyme elevation, low neutrophil count, low platelet count and lipid elevations is noted with ACTEMRA treatment in the PJIA and SJIA populations. Monitor neutrophils, platelets, ALT and AST at the time of the second administration and thereafter every 4 to 8 weeks for PJIA and every 2 to 4 weeks for SJIA. Monitor lipids as above for approved adult indications [see Dosage and Administration (2.11)].

5.5 Immunosuppression

The impact of treatment with ACTEMRA on the development of malignancies is not known but malignancies were observed in clinical studies [see Adverse Reactions (6.1)]. ACTEMRA is an immunosuppressant, and treatment with immunosuppressants may result in an increased risk of malignancies.

5.6 Hypersensitivity Reactions, Including Anaphylaxis

Hypersensitivity reactions, including anaphylaxis, have been reported in association with ACTEMRA and anaphylactic events with a fatal outcome have been reported with intravenous infusion of ACTEMRA. Anaphylaxis and other hypersensitivity reactions that required treatment discontinuation were reported in 0.1% (3 out of 2644) of patients in the 6-month controlled trials of intravenous ACTEMRA, 0.2% (8 out of 4009) of patients in the intravenous all-exposure RA population, 0.7% (8 out of 1068) in the subcutaneous 6-month controlled RA trials, and in 0.7% (10 out of 1465) of patients in the subcutaneous all-exposure population. In the SJIA controlled trial with intravenous ACTEMRA, 1 out of 112 patients (0.9%) experienced hypersensitivity reactions that required treatment discontinuation. In the PJIA controlled trial with intravenous ACTEMRA, 0 out of 188 patients (0%) in the ACTEMRA all-exposure population experienced hypersensitivity reactions that required treatment discontinuation. Reactions that required treatment discontinuation included generalized erythema, rash, and urticaria. Injection site reactions were categorized separately [see Adverse Reactions (6)].

In the postmarketing setting, events of hypersensitivity reactions, including anaphylaxis and death have occurred in patients treated with a range of doses of intravenous ACTEMRA, with or without concomitant therapies. Events have occurred in patients who received premedication. Hypersensitivity, including anaphylaxis events, have occurred both with and without previous hypersensitivity reactions and as early as the first infusion of ACTEMRA [see Adverse Reactions (6.12)]. In addition, serious cutaneous reactions, including Drug Reaction with Eosinophilia and Systemic Symptoms (DRESS), have been reported in patients with autoinflammatory conditions treated with ACTEMRA.

ACTEMRA for intravenous use should only be infused by a healthcare professional with appropriate medical support to manage anaphylaxis. For ACTEMRA subcutaneous injection, advise patients to seek immediate medical attention if they experience any symptoms of a hypersensitivity reaction. If a hypersensitivity reaction occurs, immediately discontinue ACTEMRA, treat promptly and monitor until signs and symptoms resolve.

5.7 Demyelinating Disorders

The impact of treatment with ACTEMRA on demyelinating disorders is not known, but multiple sclerosis and chronic inflammatory demyelinating polyneuropathy were reported rarely in RA clinical studies. Monitor patients for signs and symptoms potentially indicative of demyelinating disorders. Prescribers should exercise caution in considering the use of ACTEMRA in patients with preexisting or recent onset demyelinating disorders.

5.8 Active Hepatic Disease and Hepatic Impairment

Treatment with ACTEMRA is not recommended in patients with active hepatic disease or hepatic impairment [see Adverse Reactions (6.1), Use in Specific Populations (8.6)].

5.9 Vaccinations

Avoid use of live vaccines concurrently with ACTEMRA as clinical safety has not been established. No data are available on the secondary transmission of infection from persons receiving live vaccines to patients receiving ACTEMRA.

No data are available on the effectiveness of vaccination in patients receiving ACTEMRA. Because IL-6 inhibition may interfere with the normal immune response to new antigens, it is recommended that all patients, particularly pediatric or elderly patients, if possible, be brought up to date with all immunizations in agreement with current immunization guidelines prior to initiating ACTEMRA therapy. The interval between live vaccinations and initiation of ACTEMRA therapy should be in accordance with current vaccination guidelines regarding immunosuppressive agents.

6 ADVERSE REACTIONS

The following serious adverse reactions are described elsewhere in labeling:

- Serious Infections [see Warnings and Precautions (5.1)]
- Gastrointestinal Perforations [see Warnings and Precautions (5.2)]
- Laboratory Parameters [see Warnings and Precautions (5.4)]
- Immunosuppression [see Warnings and Precautions (5.5)]
- Hypersensitivity Reactions, Including Anaphylaxis [see Warnings and Precautions (5.6)]
- Demyelinating Disorders [see Warnings and Precautions (5.7)]
- Active Hepatic Disease and Hepatic Impairment [see Warnings and Precautions (5.8)]

Because clinical studies are conducted under widely varying conditions, adverse reaction rates observed in the clinical studies of a drug cannot be directly compared to rates in the clinical studies of another drug and may not predict the rates observed in a broader patient population in clinical practice.

6.1 Clinical Trials Experience in Rheumatoid Arthritis Patients Treated with Intravenous ACTEMRA (ACTEMRA-IV)

The ACTEMRA-IV data in rheumatoid arthritis (RA) includes 5 double-blind, controlled, multicenter studies. In these studies, patients received doses of ACTEMRA-IV 8 mg per kg monotherapy (288 patients), ACTEMRA-IV 8 mg per kg in combination with DMARDs (including methotrexate) (1582 patients), or ACTEMRA-IV 4 mg per kg in combination with methotrexate (774 patients).

The all exposure population includes all patients in registration studies who received at least one dose of ACTEMRA-IV. Of the 4009 patients in this population, 3577 received treatment for at least 6 months, 3309 for at least one year; 2954 received treatment for at least 2 years and 2189 for 3 years.

All patients in these studies had moderately to severely active rheumatoid arthritis. The study population had a mean age of 52 years, 82% were female and 74% were Caucasian.

The most common serious adverse reactions were serious infections [see Warnings and Precautions (5.1)]. The most commonly reported adverse reactions in controlled studies up to 24 weeks (occurring in at least 5% of patients treated with ACTEMRA-IV monotherapy or in combination with DMARDs) were upper respiratory tract infections, nasopharyngitis, headache, hypertension and increased ALT.

The proportion of patients who discontinued treatment due to any adverse reactions during the double-blind, placebo-controlled studies was 5% for patients taking ACTEMRA-IV and 3% for placebo-treated patients. The most common adverse reactions that required discontinuation of ACTEMRA-IV were increased hepatic transaminase values (per protocol requirement) and serious infections.

Overall Infections

In the 24 week, controlled clinical studies, the rate of infections in the ACTEMRA-IV monotherapy group was 119 events per 100 patient-years and was similar in the methotrexate monotherapy group. The rate of infections in the 4 mg per kg and 8 mg per kg ACTEMRA-IV plus DMARD group was 133 and 127 events per 100 patient-years, respectively, compared to 112 events per 100 patient-years in the placebo plus DMARD group. The most commonly reported infections (5% to 8% of patients) were upper respiratory tract infections and nasopharyngitis.

The overall rate of infections with ACTEMRA-IV in the all exposure population remained consistent with rates in the controlled periods of the studies.

Serious Infections

In the 24 week, controlled clinical studies, the rate of serious infections in the ACTEMRA-IV monotherapy group was 3.6 per 100 patient-years compared to 1.5 per 100 patient-years in the methotrexate group. The rate of serious infections in the 4 mg per kg and 8 mg per kg ACTEMRA-IV plus DMARD group was 4.4 and 5.3 events per 100 patient-years, respectively, compared to 3.9 events per 100 patient-years in the placebo plus DMARD group.

In the all-exposure population, the overall rate of serious infections remained consistent with rates in the controlled periods of the studies. The most common serious infections included pneumonia, urinary tract infection, cellulitis, herpes zoster, gastroenteritis, diverticulitis, sepsis and bacterial arthritis. Cases of opportunistic infections have been reported [see Warnings and Precautions (5.1)].

In the cardiovascular outcomes Study WA25204, the rate of serious infections in the ACTEMRA 8 mg/kg IV every 4 weeks group, with or without DMARD, was 4.5 per 100 patient-years, and the rate in the etanercept 50 mg weekly SC group, with or without DMARD, was 3.2 per 100 patient-years [see Clinical Studies (14.1)].

Gastrointestinal Perforations

During the 24 week, controlled clinical trials, the overall rate of gastrointestinal perforation was 0.26 events per 100 patient-years with ACTEMRA-IV therapy.

In the all-exposure population, the overall rate of gastrointestinal perforation remained consistent with rates in the controlled periods of the studies. Reports of gastrointestinal perforation were primarily reported as complications of diverticulitis including generalized purulent peritonitis, lower GI perforation, fistula and abscess. Most patients who developed gastrointestinal perforations were taking concomitant nonsteroidal anti-inflammatory medications (NSAIDs), corticosteroids, or methotrexate [see Warnings and Precautions (5.2)]. The relative contribution of these concomitant medications versus ACTEMRA-IV to the development of GI perforations is not known.

Infusion Reactions

In the 24 week, controlled clinical studies, adverse events associated with the infusion (occurring during or within 24 hours of the start of infusion) were reported in 8% and 7% of patients in the 4 mg per kg and 8 mg per kg ACTEMRA-IV plus DMARD group, respectively, compared to 5% of patients in the placebo plus DMARD group. The most frequently reported event on the 4 mg per kg and 8 mg per kg dose during the infusion was hypertension (1% for both doses), while the most frequently reported event occurring within 24 hours of finishing an infusion were headache (1% for both doses) and skin reactions (1% for both doses), including rash, pruritus and urticaria. These events were not treatment limiting.

Anaphylaxis

Hypersensitivity reactions requiring treatment discontinuation, including anaphylaxis, associated with ACTEMRA-IV were reported in 0.1% (3 out of 2644) in the 24 week, controlled trials and in 0.2% (8 out of 4009) in the all-exposure population. These reactions were generally observed during the second to fourth infusion of ACTEMRA-IV. Appropriate medical treatment should be available for immediate use in the event of a serious hypersensitivity reaction [see Warnings and Precautions (5.6)].

Laboratory Abnormalities

Neutropenia

In the 24 week, controlled clinical studies, decreases in neutrophil counts below 1000 per mm^3 occurred in 1.8% and 3.4% of patients in the 4 mg per kg and 8 mg per kg ACTEMRA-IV plus DMARD group, respectively, compared to 0.1% of patients in the placebo plus DMARD group. Approximately half of the instances of ANC below 1000 per mm^3 occurred within 8 weeks of starting therapy. Decreases in neutrophil counts below 500 per mm^3 occurred in 0.4% and 0.3% of patients in the 4 mg per kg and 8 mg per kg ACTEMRA-IV plus DMARD, respectively, compared to 0.1% of patients in the placebo plus DMARD group. There was no clear relationship between decreases in neutrophils below 1000 per mm^3 and the occurrence of serious infections.

In the all-exposure population, the pattern and incidence of decreases in neutrophil counts remained consistent with what was seen in the 24 week controlled clinical studies [see Warnings and Precautions (5.4)].

Thrombocytopenia

In the 24 week, controlled clinical studies, decreases in platelet counts below 100,000 per mm^3 occurred in 1.3% and 1.7% of patients on 4 mg per kg and 8 mg per kg ACTEMRA-IV plus DMARD, respectively, compared to 0.5% of patients on placebo plus DMARD, without associated bleeding events.

In the all-exposure population, the pattern and incidence of decreases in platelet counts remained consistent with what was seen in the 24 week controlled clinical studies [see Warnings and Precautions (5.4)].

Elevated Liver Enzymes

Liver enzyme abnormalities are summarized in Table 1. In patients experiencing liver enzyme elevation, modification of treatment regimen, such as reduction in the dose of concomitant DMARD, interruption of ACTEMRA-IV, or reduction in ACTEMRA-IV dose, resulted in decrease or normalization of liver enzymes [see Dosage and Administration (2.11)]. These elevations were not associated with clinically relevant increases in direct bilirubin, nor were they associated with clinical evidence of hepatitis or hepatic insufficiency [see Warnings and Precautions (5.3, 5.4)].

Table 1 Incidence of Liver Enzyme Abnormalities in the 24 Week Controlled Period of Studies I to V [For a description of these studies, see Section 14, Clinical Studies.]
 | ACTEMRA 8 mg per kg MONOTHERAPY | Methotrexate | ACTEMRA 4 mg per kg + DMARDs | ACTEMRA 8 mg per kg + DMARDs | Placebo + DMARDs
 | N = 288 (%) | N = 284 (%) | N = 774 (%) | N = 1582 (%) | N = 1170 (%)
AST (U/L)
> ULN to 3× ULN | 22 | 26 | 34 | 41 | 17
> 3× ULN to 5× ULN | 0.3 | 2 | 1 | 2 | 0.3
> 5× ULN | 0.7 | 0.4 | 0.1 | 0.2 | < 0.1
ALT (U/L)
> ULN to 3× ULN | 36 | 33 | 45 | 48 | 23
> 3× ULN to 5× ULN | 1 | 4 | 5 | 5 | 1
> 5× ULN | 0.7 | 1 | 1.3 | 1.5 | 0.3
ULN = Upper Limit of Normal

In the all-exposure population, the elevations in ALT and AST remained consistent with what was seen in the 24 week, controlled clinical trials.

In Study WA25204, of the 1538 patients with moderate to severe RA [see Clinical Studies (14.1)] and treated with tocilizumab, elevations in ALT or AST >3 × ULN occurred in 5.3% and 2.2% patients, respectively. One serious event of drug induced hepatitis with hyperbilirubinemia was reported in association with tocilizumab.

Lipids

Elevations in lipid parameters (total cholesterol, LDL, HDL, triglycerides) were first assessed at 6 weeks following initiation of ACTEMRA-IV in the controlled 24 week clinical trials. Increases were observed at this time point and remained stable thereafter. Increases in triglycerides to levels above 500 mg per dL were rarely observed. Changes in other lipid parameters from baseline to week 24 were evaluated and are summarized below:

- Mean LDL increased by 13 mg per dL in the ACTEMRA 4 mg per kg+DMARD arm, 20 mg per dL in the ACTEMRA 8 mg per kg+DMARD, and 25 mg per dL in ACTEMRA 8 mg per kg monotherapy.
- Mean HDL increased by 3 mg per dL in the ACTEMRA 4 mg per kg+DMARD arm, 5 mg per dL in the ACTEMRA 8 mg per kg+DMARD, and 4 mg per dL in ACTEMRA 8 mg per kg monotherapy.
- Mean LDL/HDL ratio increased by an average of 0.14 in the ACTEMRA 4 mg per kg+DMARD arm, 0.15 in the ACTEMRA 8 mg per kg+DMARD, and 0.26 in ACTEMRA 8 mg per kg monotherapy.
- ApoB/ApoA1 ratios were essentially unchanged in ACTEMRA-treated patients.

Elevated lipids responded to lipid lowering agents.

In the all-exposure population, the elevations in lipid parameters remained consistent with what was seen in the 24 week, controlled clinical trials.

Immunogenicity

As with all therapeutic proteins, there is potential for immunogenicity. The detection of antibody formation is highly dependent on the sensitivity and specificity of the assay. Additionally, the observed incidence of antibody (including neutralizing antibody) positivity in an assay may be influenced by several factors including assay methodology, sample handling, timing of sample collection, concomitant medications, and underlying disease. For these reasons, comparison of the incidence of antibodies to tocilizumab in the studies described below with the incidence of antibodies in other studies or to other products may be misleading.

In the 24 week, controlled clinical studies, a total of 2876 patients have been tested for anti-tocilizumab antibodies. Forty-six patients (2%) developed positive anti-tocilizumab antibodies, of whom 5 had an associated, medically significant, hypersensitivity reaction leading to withdrawal. Thirty patients (1%) developed neutralizing antibodies.

Malignancies

During the 24 week, controlled period of the studies, 15 malignancies were diagnosed in patients receiving ACTEMRA-IV, compared to 8 malignancies in patients in the control groups. Exposure-adjusted incidence was similar in the ACTEMRA-IV groups (1.32 events per 100 patient-years) and in the placebo plus DMARD group (1.37 events per 100 patient-years).

In the all-exposure population, the rate of malignancies remained consistent with the rate observed in the 24 week, controlled period [see Warnings and Precautions (5.5)].

Other Adverse Reactions

Adverse reactions occurring in 2% or more of patients on 4 or 8 mg per kg ACTEMRA-IV plus DMARD and at least 1% greater than that observed in patients on placebo plus DMARD are summarized in Table 2.

Table 2 Adverse Reactions Occurring in at Least 2% or More of Patients on 4 or 8 mg per kg ACTEMRA plus DMARD and at Least 1% Greater Than That Observed in Patients on Placebo plus DMARD
24 Week Phase 3 Controlled Study Population
 | ACTEMRA 8 mg per kg MONOTHERAPY | Methotrexate | ACTEMRA 4 mg per kg + DMARDs | ACTEMRA 8 mg per kg + DMARDs | Placebo + DMARDs
Preferred Term | N = 288 (%) | N = 284 (%) | N = 774 (%) | N = 1582 (%) | N = 1170 (%)
Upper Respiratory Tract Infection | 7 | 5 | 6 | 8 | 6
Nasopharyngitis | 7 | 6 | 4 | 6 | 4
Headache | 7 | 2 | 6 | 5 | 3
Hypertension | 6 | 2 | 4 | 4 | 3
ALT increased | 6 | 4 | 3 | 3 | 1
Dizziness | 3 | 1 | 2 | 3 | 2
Bronchitis | 3 | 2 | 4 | 3 | 3
Rash | 2 | 1 | 4 | 3 | 1
Mouth Ulceration | 2 | 2 | 1 | 2 | 1
Abdominal Pain Upper | 2 | 2 | 3 | 3 | 2
Gastritis | 1 | 2 | 1 | 2 | 1
Transaminase increased | 1 | 5 | 2 | 2 | 1

Other infrequent and medically relevant adverse reactions occurring at an incidence less than 2% in rheumatoid arthritis patients treated with ACTEMRA-IV in controlled trials were:

Infections and Infestations: oral herpes simplex

Gastrointestinal disorders: stomatitis, gastric ulcer

Investigations: weight increased, total bilirubin increased

Blood and lymphatic system disorders: leukopenia

General disorders and administration site conditions: edema peripheral

Respiratory, thoracic, and mediastinal disorders: dyspnea, cough

Eye disorders: conjunctivitis

Renal disorders: nephrolithiasis

Endocrine disorders: hypothyroidism

6.2 Clinical Trials Experience in Rheumatoid Arthritis Patients Treated with Subcutaneous ACTEMRA (ACTEMRA-SC)

The ACTEMRA-SC data in rheumatoid arthritis (RA) includes 2 double-blind, controlled, multicenter studies. Study SC-I was a non-inferiority study that compared the efficacy and safety of tocilizumab 162 mg administered every week subcutaneously and 8 mg/kg intravenously every four weeks in 1262 adult subjects with rheumatoid arthritis. Study SC-II was a placebo controlled superiority study that evaluated the safety and efficacy of tocilizumab 162 mg administered every other week subcutaneously or placebo in 656 patients. All patients in both studies received background non-biologic DMARDs.

The safety observed for ACTEMRA-SC administered subcutaneously was consistent with the known safety profile of intravenous ACTEMRA, with the exception of injection site reactions (ISRs), which were more common with ACTEMRA-SC compared with placebo SC injections (IV arm).

Injection Site Reactions

In the 6-month control period, in SC-I, the frequency of ISRs was 10.1% (64/631) and 2.4% (15/631) for the weekly ACTEMRA-SC and placebo SC (IV-arm) groups, respectively. In SC-II, the frequency of ISRs was 7.1% (31/437) and 4.1% (9/218) for the every other week ACTEMRA-SC and placebo groups, respectively. These ISRs (including erythema, pruritus, pain and hematoma) were mild to moderate in severity. The majority resolved without any treatment and none necessitated drug discontinuation.

Immunogenicity

In the 6-month control period in SC-I, 0.8% (5/625) in the ACTEMRA-SC arm and 0.8% (5/627) in the IV arm developed anti-tocilizumab antibodies; of these, all developed neutralizing antibodies. In SC-II, 1.6% (7/434) in the ACTEMRA-SC arm compared with 1.4 % (3/217) in the placebo arm developed anti- tocilizumab antibodies; of these, 1.4% (6/434) in the ACTEMRA-SC arm and 0.5% (1/217) in the placebo arm also developed neutralizing antibodies.

A total of 1454 (>99%) patients who received ACTEMRA-SC in the all exposure group have been tested for anti-tocilizumab antibodies. Thirteen patients (0.9%) developed anti-tocilizumab antibodies, and, of these, 12 patients (0.8%) developed neutralizing antibodies.

The rate is consistent with previous intravenous experience. No correlation of antibody development to adverse events or loss of clinical response was observed.

Laboratory Abnormalities

Neutropenia

During routine laboratory monitoring in the 6-month controlled clinical trials, a decrease in neutrophil count below 1 × 10^9/L occurred in 2.9% and 3.7% of patients receiving ACTEMRA-SC weekly and every other week, respectively.

There was no clear relationship between decreases in neutrophils below 1 × 10^9/L and the occurrence of serious infections.

Thrombocytopenia

During routine laboratory monitoring in the ACTEMRA-SC 6-month controlled clinical trials, none of the patients had a decrease in platelet count to ≤50,000/mm^3.

Elevated Liver Enzymes

During routine laboratory monitoring in the 6-month controlled clinical trials, elevation in ALT or AST ≥3 × ULN occurred in 6.5% and 1.4% of patients, respectively, receiving ACTEMRA-SC weekly and 3.4% and 0.7% receiving ACTEMRA-SC every other week.

Lipid Parameters Elevations

During routine laboratory monitoring in the ACTEMRA-SC 6-month clinical trials, 19% of patients dosed weekly and 19.6% of patients dosed every other week and 10.2% of patients on placebo experienced sustained elevations in total cholesterol > 6.2 mmol/l (240 mg/dL), with 9%, 10.4% and 5.1% experiencing a sustained increase in LDL to 4.1 mmol/l (160 mg/dL) receiving ACTEMRA-SC weekly, every other week and placebo, respectively.

6.3 Clinical Trials Experience in Giant Cell Arteritis Patients Treated with Subcutaneous ACTEMRA (ACTEMRA-SC)

The safety of subcutaneous ACTEMRA (tocilizumab) has been studied in one Phase III study (WA28119) with 251 GCA patients. The total patient years duration in the ACTEMRA-SC GCA all exposure population was 138.5 patient years during the 12-month double blind, placebo-controlled phase of the study. The overall safety profile observed in the ACTEMRA-SC treatment groups was generally consistent with the known safety profile of ACTEMRA. There was an overall higher incidence of infections in GCA patients relative to RA patients. The rate of infection/serious infection events was 200.2/9.7 events per 100 patient years in the ACTEMRA-SC weekly group and 160.2/4.4 events per 100 patient years in the ACTEMRA-SC every other week group as compared to 156.0/4.2 events per 100 patient years in the placebo + 26 week prednisone taper and 210.2/12.5 events per 100 patient years in the placebo + 52 week taper groups.

6.4 Clinical Trials Experience in Giant Cell Arteritis Patients Treated With Intravenous ACTEMRA (ACTEMRA-IV)

The safety of ACTEMRA-IV was studied in an open label PK-PD and safety study in 24 patients with GCA who were in remission on ACTEMRA-IV at time of enrollment. Patients received ACTEMRA 7 mg/kg every 4 weeks for 20 weeks, followed by 6 mg/kg every 4 weeks for 20 weeks. The total patient years exposure to treatment was 17.5 years. The overall safety profile observed for ACTEMRA administered intravenously in GCA patients was consistent with the known safety profile of ACTEMRA.

6.5 Clinical Trials Experience in Systemic Sclerosis-Associated Interstitial Lung Disease Patients Treated with Subcutaneous ACTEMRA (ACTEMRA-SC)

The safety of subcutaneous ACTEMRA was evaluated in two double-blind, placebo-controlled, multicenter studies (WA29767 and WA27788). In the Phase 3 Study WA29767, 212 patients with SSc were randomized to tocilizumab 162 mg administered every week subcutaneously or placebo for 48 weeks, followed by open-label tocilizumab 162 mg administered subcutaneously every week for another 48 weeks. In the Phase 2/3 Study WA27788, 87 patients were randomized to tocilizumab 162 mg administered every week subcutaneously or placebo for 48 weeks, followed by open-label tocilizumab 162 mg administered subcutaneously every week for another 48 weeks.

The safety profile for ACTEMRA through week 48 in WA29767 was comparable for SSc-ILD and SSc patients overall, and in both studies was consistent with the known safety profile of ACTEMRA.

Immunogenicity

In the two clinical studies, WA29767 and WA27788, the incidence of treatment-induced anti-TCZ antibodies at week 96 was low (3 out of 169 patients, 1.8%). These anti-drug antibodies were of neutralizing potential, and none of the patients experienced hypersensitivity reactions.

6.6 Clinical Trials Experience in Polyarticular Juvenile Idiopathic Arthritis Patients Treated With Intravenous ACTEMRA (ACTEMRA-IV)

The safety of ACTEMRA-IV was studied in 188 pediatric patients 2 to 17 years of age with PJIA who had an inadequate clinical response or were intolerant to methotrexate. The total patient exposure in the ACTEMRA-IV all exposure population (defined as patients who received at least one dose of ACTEMRA-IV) was 184.4 patient years. At baseline, approximately half of the patients were taking oral corticosteroids and almost 80% were taking methotrexate. In general, the types of adverse drug reactions in patients with PJIA were consistent with those seen in RA and SJIA patients [see Adverse Reactions (6.1 and 6.8)].

Infections

The rate of infections in the ACTEMRA-IV all exposure population was 163.7 per 100 patient years. The most common events observed were nasopharyngitis and upper respiratory tract infections. The rate of serious infections was numerically higher in patients weighing less than 30 kg treated with 10 mg/kg tocilizumab (12.2 per 100 patient years) compared to patients weighing at or above 30 kg, treated with 8 mg/kg tocilizumab (4.0 per 100 patient years). The incidence of infections leading to dose interruptions was also numerically higher in patients weighing less than 30 kg treated with 10 mg/kg tocilizumab (21%) compared to patients weighing at or above 30 kg, treated with 8 mg/kg tocilizumab (8%).

Infusion Reactions

In PJIA patients, infusion-related reactions are defined as all events occurring during or within 24 hours of an infusion. In the ACTEMRA-IV all exposure population, 11 patients (6%) experienced an event during the infusion, and 38 patients (20.2%) experienced an event within 24 hours of an infusion. The most common events occurring during infusion were headache, nausea and hypotension, and occurring within 24 hours of infusion were dizziness and hypotension. In general, the adverse drug reactions observed during or within 24 hours of an infusion were similar in nature to those seen in RA and SJIA patients [see Adverse Reactions (6.1 and 6.8)].

No clinically significant hypersensitivity reactions associated with tocilizumab and requiring treatment discontinuation were reported.

Immunogenicity

One patient, in the 10 mg/kg less than 30 kg group, developed positive anti-tocilizumab antibodies without developing a hypersensitivity reaction and subsequently withdrew from the study.

Laboratory Abnormalities

Neutropenia

During routine laboratory monitoring in the ACTEMRA-IV all exposure population, a decrease in neutrophil counts below 1 × 10^9 per L occurred in 3.7% of patients.

There was no clear relationship between decreases in neutrophils below 1 × 10^9 per L and the occurrence of serious infections.

Thrombocytopenia

During routine laboratory monitoring in the ACTEMRA-IV all exposure population, 1% of patients had a decrease in platelet count at or less than 50,000 per mm^3 without associated bleeding events.

Elevated Liver Enzymes

During routine laboratory monitoring in the ACTEMRA-IV all exposure population, elevation in ALT or AST at or greater than 3 × ULN occurred in 4% and less than 1% of patients, respectively.

Lipids

During routine laboratory monitoring in the tocilizumab all exposure population, elevation in total cholesterol greater than 1.5-2 × ULN occurred in one patient (0.5%) and elevation in LDL greater than 1.5-2 × ULN occurred in one patient (0.5%).

6.7 Clinical Trials Experience in Polyarticular Juvenile Idiopathic Arthritis Patients Treated With Subcutaneous ACTEMRA (ACTEMRA-SC)

The safety of ACTEMRA-SC was studied in 52 pediatric patients 1 to 17 years of age with PJIA who had an inadequate clinical response or were intolerant to methotrexate. The total patient exposure in the PJIA ACTEMRA-SC population (defined as patients who received at least one dose of ACTEMRA-SC and accounting for treatment discontinuation) was 49.5 patient years. In general, the safety observed for ACTEMRA administered subcutaneously was consistent with the known safety profile of intravenous ACTEMRA, with the exception of injection site reactions (ISRs), and neutropenia.

Injection Site Reactions

During the 1-year study, a frequency of 28.8% (15/52) ISRs was observed in ACTEMRA-SC treated PJIA patients. These ISRs occurred in a greater proportion of patients at or above 30 kg (44.0%) compared with patients below 30 kg (14.8%). All ISRs were mild in severity and none of the ISRs required patient withdrawal from treatment or dose interruption. A higher frequency of ISRs was observed in ACTEMRA-SC treated PJIA patients compared to what was seen in adult RA or GCA patients [see Adverse Reactions (6.2 and 6.3)].

Immunogenicity

Three patients, 1 patient below 30 kg and 2 patients at or above 30 kg, developed positive anti-tocilizumab antibodies with neutralizing potential without developing a serious or clinically significant hypersensitivity reaction. One patient subsequently withdrew from the study.

Neutropenia

During routine laboratory monitoring in the ACTEMRA-SC all exposure population, a decrease in neutrophil counts below 1 × 10^9 per L occurred in 15.4% of patients, and was more frequently observed in the patients less than 30 kg (25.9%) compared to patients at or above 30 kg (4.0%). There was no clear relationship between decreases in neutrophils below 1 × 10^9 per L and the occurrence of serious infections.

6.8 Clinical Trials Experience in Systemic Juvenile Idiopathic Arthritis Patients Treated with Intravenous ACTEMRA (ACTEMRA-IV)

The data described below reflect exposure to ACTEMRA-IV in one randomized, double-blind, placebo-controlled trial of 112 pediatric patients with SJIA 2 to 17 years of age who had an inadequate clinical response to nonsteroidal anti-inflammatory drugs (NSAIDs) or corticosteroids due to toxicity or lack of efficacy. At baseline, approximately half of the patients were taking 0.3 mg/kg/day corticosteroids or more, and almost 70% were taking methotrexate. The trial included a 12 week controlled phase followed by an open-label extension. In the 12 week double-blind, controlled portion of the clinical study 75 patients received treatment with ACTEMRA-IV (8 or 12 mg per kg based upon body weight). After 12 weeks or at the time of escape, due to disease worsening, patients were treated with ACTEMRA-IV in the open-label extension phase.

The most common adverse events (at least 5%) seen in ACTEMRA-IV treated patients in the 12 week controlled portion of the study were: upper respiratory tract infection, headache, nasopharyngitis and diarrhea.

Infections

In the 12 week controlled phase, the rate of all infections in the ACTEMRA-IV group was 345 per 100 patient-years and 287 per 100 patient-years in the placebo group. In the open label extension over an average duration of 73 weeks of treatment, the overall rate of infections was 304 per 100 patient-years.

In the 12 week controlled phase, the rate of serious infections in the ACTEMRA-IV group was 11.5 per 100 patient years. In the open label extension over an average duration of 73 weeks of treatment, the overall rate of serious infections was 11.4 per 100 patient years. The most commonly reported serious infections included pneumonia, gastroenteritis, varicella, and otitis media.

Macrophage Activation Syndrome

In the 12 week controlled study, no patient in any treatment group experienced macrophage activation syndrome (MAS) while on assigned treatment; 3 per 112 (3%) developed MAS during open-label treatment with ACTEMRA-IV. One patient in the placebo group escaped to ACTEMRA-IV 12 mg per kg at Week 2 due to severe disease activity, and ultimately developed MAS at Day 70. Two additional patients developed MAS during the long-term extension. All 3 patients had ACTEMRA-IV dose interrupted (2 patients) or discontinued (1 patient) for the MAS event, received treatment, and the MAS resolved without sequelae. Based on a limited number of cases, the incidence of MAS does not appear to be elevated in the ACTEMRA-IV SJIA clinical development experience; however no definitive conclusions can be made.

Infusion Reactions

Patients were not premedicated, however most patients were on concomitant corticosteroids as part of their background treatment for SJIA. Infusion related reactions were defined as all events occurring during or within 24 hours after an infusion. In the 12 week controlled phase, 4% of ACTEMRA-IV and 0% of placebo treated patients experienced events occurring during infusion. One event (angioedema) was considered serious and life-threatening, and the patient was discontinued from study treatment.

Within 24 hours after infusion, 16% of patients in the ACTEMRA-IV treatment group and 5% of patients in the placebo group experienced an event. In the ACTEMRA-IV group the events included rash, urticaria, diarrhea, epigastric discomfort, arthralgia and headache. One of these events, urticaria, was considered serious.

Anaphylaxis

Anaphylaxis was reported in 1 out of 112 patients (less than 1%) treated with ACTEMRA-IV during the controlled and open label extension study [see Warnings and Precautions (5.6)].

Immunogenicity

All 112 patients were tested for anti-tocilizumab antibodies at baseline. Two patients developed positive anti-tocilizumab antibodies: one of these patients experienced serious adverse events of urticaria and angioedema consistent with an anaphylactic reaction which led to withdrawal; the other patient developed macrophage activation syndrome while on escape therapy and was discontinued from the study.

Laboratory Abnormalities

Neutropenia

During routine monitoring in the 12 week controlled phase, a decrease in neutrophil below 1 × 10^9 per L occurred in 7% of patients in the ACTEMRA-IV group, and in no patients in the placebo group. In the open label extension over an average duration of 73 weeks of treatment, a decreased neutrophil count occurred in 17% of the ACTEMRA-IV group. There was no clear relationship between decrease in neutrophils below 1 × 10^9 per L and the occurrence of serious infections.

Thrombocytopenia

During routine monitoring in the 12 week controlled phase, 1% of patients in the ACTEMRA-IV group and 3% in the placebo group had a decrease in platelet count to no more than 100,000 per mm^3.

In the open label extension over an average duration of 73 weeks of treatment, decreased platelet count occurred in 4% of patients in the ACTEMRA-IV group, with no associated bleeding.

Elevated Liver Enzymes

During routine laboratory monitoring in the 12 week controlled phase, elevation in ALT or AST at or above 3× ULN occurred in 5% and 3% of patients, respectively in the ACTEMRA-IV group and in 0% of placebo patients.

In the open label extension over an average duration of 73 weeks of treatment, the elevation in ALT or AST at or above 3× ULN occurred in 13% and 5% of ACTEMRA-IV treated patients, respectively.

Lipids

During routine laboratory monitoring in the 12 week controlled phase, elevation in total cholesterol greater than 1.5× ULN – 2× ULN occurred in 1.5% of the ACTEMRA-IV group and in 0% of placebo patients. Elevation in LDL greater than 1.5× ULN – 2× ULN occurred in 1.9% of patients in the ACTEMRA-IV group and 0% of the placebo group.

In the open label extension study over an average duration of 73 weeks of treatment, the pattern and incidence of elevations in lipid parameters remained consistent with the 12 week controlled study data.

6.9 Clinical Trials Experience in Systemic Juvenile Idiopathic Arthritis Patients Treated with Subcutaneous ACTEMRA (ACTEMRA-SC)

The safety profile of ACTEMRA-SC was studied in 51 pediatric patients 1 to 17 years of age with SJIA who had an inadequate clinical response to NSAIDs and corticosteroids. In general, the safety observed for ACTEMRA administered subcutaneously was consistent with the known safety profile of intravenous ACTEMRA, with the exception of ISRs where a higher frequency was observed in ACTEMRA-SC treated SJIA patients compared to PJIA patients and adult RA or GCA patients [see Adverse Reactions (6.2, 6.3 and 6.7)].

Injection Site Reactions (ISRs)

A total of 41.2% (21/51) SJIA patients experienced ISRs to ACTEMRA-SC. The most common ISRs were erythema, pruritus, pain, and swelling at the injection site. The majority of ISRs reported were Grade 1 events and all ISRs reported were non-serious and none required patient withdrawal from treatment or dose interruption.

Immunogenicity

Forty-six of the 51 (90.2%) patients who were tested for anti-tocilizumab antibodies at baseline had at least one post-baseline screening assay result. No patient developed positive anti-tocilizumab antibodies post-baseline.

6.10 Clinical Trials Experience in Patients with Cytokine Release Syndrome Treated with Intravenous ACTEMRA (ACTEMRA-IV)

In a retrospective analysis of pooled outcome data from multiple clinical trials 45 patients were treated with tocilizumab 8 mg/kg (12 mg/kg for patients less than 30 kg) with or without additional high-dose corticosteroids for severe or life-threatening CAR T-cell-induced CRS. A median of 1 dose of tocilizumab (range, 1-4 doses) was administered. No adverse reactions related to tocilizumab were reported [see Clinical Studies (14.10)].

6.11 Clinical Trials Experience in COVID-19 Patients Treated with Intravenous ACTEMRA (ACTEMRA-IV)

The safety of ACTEMRA in hospitalized adult COVID-19 patients was evaluated in a pooled safety population that includes patients enrolled in EMPACTA, COVACTA, AND REMDACTA. The analysis of adverse reactions included a total of 974 patients exposed to ACTEMRA. Patients received a single, 60-minute infusion of intravenous ACTEMRA 8 mg/kg (maximum dose of 800 mg). If clinical signs or symptoms worsened or did not improve, one additional dose of ACTEMRA 8 mg/kg could be administered between 8- 24 hours after the initial dose.

Adverse reactions summarized in Table 3 occurred in at least 3% of ACTEMRA-treated patients and more commonly than in patients on placebo in the pooled safety population.

Table 3 Adverse Reactions [Patients are counted once for each category regardless of the number of reactions] Identified From the Pooled COVID-19 Adult Safety Population
Adverse Reaction | ACTEMRA 8 mg per kg | Placebo
Adverse Reaction | N = 974 (%) | N = 483 (%)
Hepatic Transaminases increased | 10% | 8%
Constipation | 9 % | 8%
Urinary tract infection | 5% | 4%
Hypertension | 4% | 1%
Hypokalaemia | 4% | 3%
Anxiety | 4% | 2%
Diarrhea | 4% | 2%
Insomnia | 4% | 3%
Nausea | 3% | 2%

In the pooled safety population, the rates of infection/serious infection events were 30%/19% in patients receiving ACTEMRA versus 32%/23% receiving placebo.

Laboratory Abnormalities

In the pooled adult safety population of EMPACTA, COVACTA, and REMDACTA, neutrophil counts <1000 cells/mcl occurred in 3.4% of patients who received ACTEMRA and 0.5% of patients who received placebo. Platelet counts <50,000 cells/mcl occurred in 3.2% of patients who received ACTEMRA and 1.5% of patients who received placebo. ALT or AST at or above 5× ULN occurred in 11.7% of patients who received ACTEMRA and 9.9% of patients who received placebo.

6.12 Postmarketing Experience

The following adverse reactions have been identified during post-approval use of ACTEMRA. Because these reactions are reported voluntarily from a population of uncertain size, it is not always possible to reliably estimate their frequency or establish a causal relationship to drug exposure.

- Hypersensitivity Reactions: Fatal anaphylaxis, Stevens-Johnson Syndrome, Drug Reaction with Eosinophilia and Systemic Symptoms (DRESS) [see Warnings and Precautions (5.6)]
- Pancreatitis
- Drug-induced liver injury, Hepatitis, Hepatic failure, Jaundice [see Warnings and Precautions (5.3)]
- Hypofibrinogenemia

7 DRUG INTERACTIONS

7.1 Concomitant Drugs for Treatment of Adult Indications

In RA patients, population pharmacokinetic analyses did not detect any effect of methotrexate (MTX), non-steroidal anti-inflammatory drugs or corticosteroids on tocilizumab clearance. Concomitant administration of a single intravenous dose of 10 mg/kg ACTEMRA with 10-25 mg MTX once weekly had no clinically significant effect on MTX exposure. ACTEMRA has not been studied in combination with biological DMARDs such as TNF antagonists [see Dosage and Administration (2.2)].

In GCA patients, no effect of concomitant corticosteroid on tocilizumab exposure was observed.

7.2 Interactions with CYP450 Substrates

Cytochrome P450s in the liver are down-regulated by infection and inflammation stimuli including cytokines such as IL-6. Inhibition of IL-6 signaling in RA patients treated with tocilizumab may restore CYP450 activities to higher levels than those in the absence of tocilizumab leading to increased metabolism of drugs that are CYP450 substrates. In vitro studies showed that tocilizumab has the potential to affect expression of multiple CYP enzymes including CYP1A2, CYP2B6, CYP2C9, CYP2C19, CYP2D6 and CYP3A4. Its effect on CYP2C8 or transporters is unknown. In vivo studies with omeprazole, metabolized by CYP2C19 and CYP3A4, and simvastatin, metabolized by CYP3A4, showed up to a 28% and 57% decrease in exposure one week following a single dose of ACTEMRA, respectively. The effect of tocilizumab on CYP enzymes may be clinically relevant for CYP450 substrates with narrow therapeutic index, where the dose is individually adjusted. Upon initiation or discontinuation of ACTEMRA, in patients being treated with these types of medicinal products, perform therapeutic monitoring of effect (e.g., warfarin) or drug concentration (e.g., cyclosporine or theophylline) and the individual dose of the medicinal product adjusted as needed. Exercise caution when coadministering ACTEMRA with CYP3A4 substrate drugs where decrease in effectiveness is undesirable, e.g., oral contraceptives, lovastatin, atorvastatin, etc. The effect of tocilizumab on CYP450 enzyme activity may persist for several weeks after stopping therapy [see Clinical Pharmacology (12.3)].

7.3 Live Vaccines

Avoid use of live vaccines concurrently with ACTEMRA [see Warnings and Precautions (5.9)].

8 USE IN SPECIFIC POPULATIONS

8.1 Pregnancy

Risk Summary

The available data with ACTEMRA from a pregnancy exposure registry, retrospective cohort study, pharmacovigilance, and published literature are insufficient to draw conclusions about a drug-associated risk of major birth defects, miscarriage, or other adverse maternal or fetal outcomes. These studies had methodological limitations, including small sample size of tocilizumab exposed groups, missing exposure and outcomes information, and lack of adjustment for confounders. Monoclonal antibodies, such as tocilizumab, are actively transported across the placenta during the third trimester of pregnancy and may affect immune response in the in utero exposed infant [see Clinical Considerations]. In animal reproduction studies, intravenous administration of tocilizumab to Cynomolgus monkeys during organogenesis caused abortion/embryo-fetal death at doses 1.25 times and higher than the maximum recommended human dose by the intravenous route of 8 mg per kg every 2 to 4 weeks. The literature in animals suggests that inhibition of IL-6 signaling may interfere with cervical ripening and dilatation and myometrial contractile activity leading to potential delays of parturition [see Data]. Based on the animal data, there may be a potential risk to the fetus.

The estimated background risk of major birth defects and miscarriage for the indicated population is unknown. All pregnancies have a background risk of birth defect, loss or other adverse outcomes. In the U.S. general population, the estimated background risk of major birth defects and miscarriage in clinically recognized pregnancies is 2 to 4% and 15 to 20%, respectively.

Clinical Considerations

Fetal/Neonatal adverse reactions

Monoclonal antibodies are increasingly transported across the placenta as pregnancy progresses, with the largest amount transferred during the third trimester. Risks and benefits should be considered prior to administering live or live-attenuated vaccines to infants exposed to ACTEMRA in utero [see Warnings and Precautions 5.9)].

Disease-associated Maternal Risk

Published data suggest that the risk of adverse pregnancy outcomes in women with rheumatoid arthritis is associated with increased disease activity. Adverse pregnancy outcomes include preterm delivery (before 37 weeks of gestation), low birth weight (less than 2500 g) infants, and small for gestational age at birth.

Data

Animal Data

An embryo-fetal developmental toxicity study was performed in which pregnant Cynomolgus monkeys were treated intravenously with tocilizumab at daily doses of 2, 10, or 50 mg/ kg during organogenesis from gestation day (GD) 20-50. Although there was no evidence for a teratogenic/dysmorphogenic effect at any dose, tocilizumab produced an increase in the incidence of abortion/embryo-fetal death at doses 1.25 times and higher the MRHD by the intravenous route at maternal intravenous doses of 10 and 50 mg/ kg. Testing of a murine analogue of tocilizumab in mice did not yield any evidence of harm to offspring during the pre- and postnatal development phase when dosed at 50 mg/kg intravenously with treatment every three days from implantation (GD 6) until post-partum day 21 (weaning). There was no evidence for any functional impairment of the development and behavior, learning ability, immune competence and fertility of the offspring.

Parturition is associated with significant increases of IL-6 in the cervix and myometrium. The literature suggests that inhibition of IL-6 signaling may interfere with cervical ripening and dilatation and myometrial contractile activity leading to potential delays of parturition. For mice deficient in IL-6 (ll6-/- null mice), parturition was delayed relative to wild-type (ll6+/+) mice. Administration of recombinant IL-6 to ll6-/- null mice restored the normal timing of delivery.

8.2 Lactation

Risk Summary

No information is available on the presence of tocilizumab in human milk, the effects of the drug on the breastfed infant, or the effects of the drug on milk production. Maternal immunoglobulin G (IgG) is present in human milk. If tocilizumab is transferred into human milk, the effects of local exposure in the gastrointestinal tract and potential limited systemic exposure in the infant to tocilizumab are unknown. The lack of clinical data during lactation precludes clear determination of the risk of ACTEMRA to an infant during lactation; therefore the developmental and health benefits of breastfeeding should be considered along with the mother's clinical need for ACTEMRA and the potential adverse effects on the breastfed child from tocilizumab or from the underlying maternal condition.

8.4 Pediatric Use

ACTEMRA by intravenous use is indicated for the treatment of pediatric patients with:

- Active systemic juvenile idiopathic arthritis in patients 2 years of age and older
- Active polyarticular juvenile idiopathic arthritis in patients 2 years of age and older
- Severe or life-threatening CAR T cell-induced cytokine release syndrome (CRS) in patients 2 years of age and older.
- Hospitalized Coronavirus disease 2019 (COVID-19) patients 2 years of age and older who are receiving systemic corticosteroids and require supplemental oxygen, non-invasive or invasive mechanical ventilation, or extracorporeal membrane oxygenation (ECMO).

ACTEMRA by subcutaneous use is indicated for the treatment of pediatric patients with:

- Active polyarticular juvenile idiopathic arthritis in patients 2 years of age and older
- Active systemic juvenile idiopathic arthritis in patients 2 years of age and older

The safety and effectiveness of ACTEMRA in pediatric patients with conditions other than PJIA, SJIA, CRS or COVID-19 have not been established. The safety and effectiveness in pediatric patients below the age of 2 have not been established in PJIA, SJIA, CRS or COVID-19.

Systemic Juvenile Idiopathic Arthritis – Intravenous Use

A multicenter, open-label, single arm study to evaluate the PK, safety and exploratory PD and efficacy of ACTEMRA over 12-weeks in SJIA patients (N=11) under 2 years of age was conducted. Patients received intravenous ACTEMRA 12 mg/kg every two weeks. Concurrent use of stable background treatment with corticosteroids, MTX, and/or non-steroidal anti-inflammatory drugs was permitted. Patients who completed the 12-week period could continue to the optional extension period (a total of 52-weeks or until the age of 2 years, whichever was longer).

The primary PK endpoints (Cmax, Ctrough and AUC2weeks) of ACTEMRA at steady-state in this study were within the ranges of these parameters observed in patients with SJIA aged 2 to 17 years.

The safety and immunogenicity of ACTEMRA for patients with SJIA under 2 years of age was assessed descriptively. SAEs, AEs leading to discontinuation, and infectious AEs were reported by 27.3%, 36.4%, and 81.8% of patients. Six patients (54.5%) experienced hypersensitivity reactions, defined as all adverse events occurring during or within 24 hours after an infusion considered related to ACTEMRA. Three of these patients experienced serious hypersensitivity reactions and were withdrawn from the study. Three patients with hypersensitivity reactions (two with serious hypersensitivity reactions) developed treatment induced anti-tocilizumab antibodies after the event. There were no cases of MAS based on the protocol-specified criteria, but 2 cases of suspected MAS based on Ravelli criteria [Ravelli A, Minoia F, Davì S on behalf of the Paediatric Rheumatology International Trials Organisation, the Childhood Arthritis and Rheumatology Research Alliance, the Pediatric Rheumatology Collaborative Study Group, and the Histiocyte Society, et al. 2016 Classification Criteria for Macrophage Activation Syndrome Complicating Systemic Juvenile Idiopathic Arthritis. Annals of the Rheumatic Diseases 2016;75:481-489.] .

Cytokine Release Syndrome – Intravenous Use

In the retrospective analysis of pooled outcome data for patients treated with ACTEMRA for CAR T cell-induced CRS, 25 patients were children (2 years up to 12 years of age), and 17 patients were adolescents (12 years up to 18 years of age). There were no differences between the pediatric patients and the adults for safety or efficacy.

COVID-19 – Intravenous Use

The safety and effectiveness of ACTEMRA have been established for the treatment of pediatric patients aged 2 years and older with COVID-19. Use of ACTEMRA in these age groups is supported by evidence from adequate and well-controlled studies of ACTEMRA in adults with COVID-19 [See Adverse Reactions (6.11) and Clinical Studies (14.11)], predicted pharmacokinetic data modeling and simulation for pediatric patients aged 2 years and older with COVID-19 [See Clinical Pharmacology (12.3)], safety data from a randomized, double-blind, placebo-controlled study of ACTEMRA in pediatric patients aged 2 years and older with systemic juvenile idiopathic arthritis, and additional uncontrolled pharmacovigilance data in pediatric patients aged 2 years and older with COVID-19 who received ACTEMRA under Emergency Use Authorization.

The safety and effectiveness of ACTEMRA has not been established in pediatric COVID-19 patients younger than 2 years of age.

8.5 Geriatric Use

Of the 2644 patients who received ACTEMRA in Studies I to V [see Clinical Studies (14)], a total of 435 rheumatoid arthritis patients were 65 years of age and older, including 50 patients 75 years and older. Of the 1069 patients who received ACTEMRA-SC in studies SC-I and SC-II there were 295 patients 65 years of age and older, including 41 patients 75 years and older. The frequency of serious infection among ACTEMRA treated subjects 65 years of age and older was higher than those under the age of 65. As there is a higher incidence of infections in the elderly population in general, caution should be used when treating the elderly.

Clinical studies that included ACTEMRA for CRS did not include sufficient numbers of patients aged 65 and over to determine whether they respond differently from younger patients.

In the EMPACTA, COVACTA, and REMDACTA studies, of the 974 COVID-19 patients in the ACTEMRA arm, 375 (39%) were 65 years of age or older. No overall differences in safety or effectiveness of ACTEMRA were observed between patients 65 years of age and older and those under the age of 65 years of age in these studies [see Adverse Reactions (6.1) and Clinical Studies (14.11)].

In the RECOVERY study, of the 2022 COVID-19 patients in the ACTEMRA arm, 930 (46%) were 65 years of age or older. No overall differences in effectiveness of ACTEMRA were observed between patients 65 years of age and older and those under the age 65 years of age in this study [see Clinical Studies (14.11)].

8.6 Hepatic Impairment

The safety and efficacy of ACTEMRA have not been studied in patients with hepatic impairment, including patients with positive HBV and HCV serology [see Warnings and Precautions (5.8)].

8.7 Renal Impairment

No dose adjustment is required in patients with mild or moderate renal impairment. ACTEMRA has not been studied in patients with severe renal impairment [see Clinical Pharmacology (12.3)].

9 DRUG ABUSE AND DEPENDENCE

No studies on the potential for ACTEMRA to cause dependence have been performed. However, there is no evidence from the available data that ACTEMRA treatment results in dependence.

10 OVERDOSAGE

There are limited data available on overdoses with ACTEMRA. One case of accidental overdose was reported with intravenous ACTEMRA in which a patient with multiple myeloma received a dose of 40 mg per kg. No adverse drug reactions were observed. No serious adverse drug reactions were observed in healthy volunteers who received single doses of up to 28 mg per kg, although all 5 patients at the highest dose of 28 mg per kg developed dose-limiting neutropenia.

In case of an overdose, it is recommended that the patient be monitored for signs and symptoms of adverse reactions. Patients who develop adverse reactions should receive appropriate symptomatic treatment.

11 DESCRIPTION

Tocilizumab is a recombinant humanized anti-human interleukin 6 (IL-6) receptor monoclonal antibody of the immunoglobulin IgG1κ (gamma 1, kappa) subclass with a typical H2L2 polypeptide structure. Each light chain and heavy chain consists of 214 and 448 amino acids, respectively. The four polypeptide chains are linked intra- and inter-molecularly by disulfide bonds. ACTEMRA has a molecular weight of approximately 148 kDa. The antibody is produced in mammalian (Chinese hamster ovary) cells.

Intravenous Infusion

ACTEMRA (tocilizumab) injection is a sterile, clear, colorless to pale yellow, preservative-free solution for further dilution prior to intravenous infusion with a pH of approximately 6.5. Each single-dose vial, formulated with a disodium phosphate dodecahydrate/sodium dihydrogen phosphate dihydrate buffered solution, is available at a concentration of 20 mg/mL containing 80 mg/4 mL, 200 mg/10 mL, or 400 mg/20 mL of ACTEMRA. Each mL of solution contains polysorbate 80 (0.5 mg), sucrose (50 mg), and Water for Injection, USP.

Subcutaneous Injection

ACTEMRA (tocilizumab) injection is a sterile, clear, colorless to slightly yellowish, preservative-free, histidine buffered solution for subcutaneous use with a pH of approximately 6.0.

It is supplied in a ready-to-use, single-dose 0.9 mL prefilled syringe (PFS) with a needle safety device or a ready-to-use, single-dose 0.9 mL autoinjector that delivers 162 mg tocilizumab, L-arginine hydrochloride (19 mg), L-histidine (1.52 mg), L-histidine hydrochloride monohydrate (1.74 mg), L-methionine (4.03 mg), polysorbate 80 (0.18 mg), and Water for Injection, USP.

12 CLINICAL PHARMACOLOGY

12.1 Mechanism of Action

Tocilizumab binds to both soluble and membrane-bound IL-6 receptors (sIL-6R and mIL-6R), and has been shown to inhibit IL-6-mediated signaling through these receptors. IL-6 is a pleiotropic pro-inflammatory cytokine produced by a variety of cell types including T- and B-cells, lymphocytes, monocytes and fibroblasts. IL-6 has been shown to be involved in diverse physiological processes such as T-cell activation, induction of immunoglobulin secretion, initiation of hepatic acute phase protein synthesis, and stimulation of hematopoietic precursor cell proliferation and differentiation. IL-6 is also produced by synovial and endothelial cells leading to local production of IL-6 in joints affected by inflammatory processes such as rheumatoid arthritis.

12.2 Pharmacodynamics

In clinical studies in RA patients with the 4 mg per kg and 8 mg per kg intravenous doses or the 162 mg weekly and every other weekly subcutaneous doses of ACTEMRA, decreases in levels of C-reactive protein (CRP) to within normal ranges were seen as early as week 2. Changes in pharmacodynamic parameters were observed (i.e., decreases in rheumatoid factor, erythrocyte sedimentation rate (ESR), serum amyloid A, fibrinogen and increases in hemoglobin) with doses, however the greatest improvements were observed with 8 mg per kg ACTEMRA. Pharmacodynamic changes were also observed to occur after ACTEMRA administration in GCA, SSc-ILD, PJIA, and SJIA patients (decreases in CRP, ESR, and increases in hemoglobin). The relationship between these pharmacodynamic findings and clinical efficacy is not known.

In healthy subjects administered ACTEMRA in doses from 2 to 28 mg per kg intravenously and 81 to 162 mg subcutaneously, absolute neutrophil counts decreased to the nadir 3 to 5 days following ACTEMRA administration. Thereafter, neutrophils recovered towards baseline in a dose dependent manner. Rheumatoid arthritis and GCA patients demonstrated a similar pattern of absolute neutrophil counts following ACTEMRA administration [see Warnings and Precautions (5.4)].

12.3 Pharmacokinetics

PK of tocilizumab is characterized by nonlinear elimination which is a combination of linear clearance and Michaelis-Menten elimination. The nonlinear part of tocilizumab elimination leads to an increase in exposure that is more than dose-proportional. The pharmacokinetic parameters of tocilizumab do not change with time. Due to the dependence of total clearance on tocilizumab serum concentrations, the half-life of tocilizumab is also concentration-dependent and varies depending on the serum concentration level. Population pharmacokinetic analyses in any patient population tested so far indicate no relationship between apparent clearance and the presence of anti-drug antibodies.

Rheumatoid Arthritis - Intravenous and Subcutaneous Administration

The pharmacokinetics in healthy subjects and RA patients suggest that PK is similar between the two populations.

The population PK model was developed from an analysis dataset composed of an IV dataset of 1793 patients from Study I, Study III, Study IV, and Study V, and from an IV and SC dataset of 1759 patients from Studies SC-I and SC-II. Cmean is included in place of AUCtau, since for dosing regimens with different inter-dose intervals, the mean concentration over the dosing period characterizes the comparative exposure better than AUCtau.

At high serum concentrations, when total clearance of tocilizumab is dominated by linear clearance, a terminal half-life of approximately 21.5 days was derived from the population parameter estimates.

For doses of 4 mg/kg tocilizumab given every 4 weeks intravenously, the estimated median (range) Cmax, Ctrough, and Cmean of tocilizumab at steady state were 86.1 (44.8–202) mcg/mL, 0.1 (0.0–14.6) mcg/mL, and 18.0 (8.9–50.7) mcg/mL, respectively. For doses of 8 mg/kg tocilizumab given every 4 weeks intravenously, the estimated median (range) Cmax, Ctrough, and Cmean of tocilizumab were 176 (75.4–557) mcg/mL, 13.4 (0.1–154) mcg/mL, and 54.0 (17–260) mcg/mL, respectively. Cmax increased dose-proportionally between doses of 4 and 8 mg/kg IV every 4 weeks, while a greater than dose-proportional increase was observed in Cmean and Ctrough. At steady-state, Cmean and Ctrough were 3.0 and 134 fold higher at 8 mg/kg as compared to 4 mg/kg, respectively.

The accumulation ratios for AUC and Cmax after multiple doses of 4 and 8 mg/kg IV Q4W are low, while the accumulation ratios for Ctrough are higher (2.62 and 2.47, respectively). For Cmax, greater than 90% of the steady-state value was reached after the 1st IV infusion. For AUCtau and Cmean, 90% of the steady-state value was reached after the 1st and 3rd infusion for 4 mg/kg and 8 mg/kg IV, while for Ctrough, approximately 90% of the steady-state value was reached after the 4th IV infusion after both doses.

For doses of 162 mg given every other week subcutaneously, the estimated median (range) steady-state Cmax, Ctrough, and Cmean of tocilizumab were 12.1 (0.4–49.3) mcg/mL, 4.1 (0.0–34.2) mcg/mL, and 9.2 (0.2–43.6) mcg/mL, respectively.

For doses of 162 mg given every week subcutaneously, the estimated median (range) steady-state Cmax, Ctrough, and Cmean of tocilizumab were 49.8 (3–150) mcg/mL, 42.9 (1.3–144) mcg/mL, and 47.3 (2.4–147) mcg/mL, respectively. Exposures after the 162 mg SC QW regimen were greater by 5.1 (Cmean) to 10.5 fold (Ctrough) compared to the 162 mg SC Q2W regimen.

Accumulation ratios after multiple doses of either SC regimen were higher than after IV regimen with the highest ratios for Ctrough (6.02 and 6.30, for 162 mg SC Q2W and 162 mg SC QW, respectively). The higher accumulation for Ctrough was expected based on the nonlinear clearance contribution at lower concentrations. For Cmax, greater than 90% of the steady-state value was reached after the 5th SC and the 12th SC injection with the Q2W and QW regimens, respectively. For AUCtau and Cmean, 90% of the steady-state value was reached after the 6th and 12th injections for the 162 mg SC Q2W and QW regimens, respectively. For Ctrough, approximately 90% of the steady-state value was reached after the 6th and 12th injections for the 162 mg SC Q2W and QW regimens, respectively.

Population PK analysis identified body weight as a significant covariate impacting the pharmacokinetics of tocilizumab. When given IV on a mg/kg basis, individuals with body weight ≥ 100 kg are predicted to have mean steady-state exposures higher than mean values for the patient population. Therefore, tocilizumab doses exceeding 800 mg per infusion are not recommended in patients with RA [see Dosage and Administration (2.2)]. Due to the flat dosing employed for SC administration of tocilizumab, no modifications are necessary by this dosing route.

Giant Cell Arteritis – Subcutaneous and Intravenous Administration

The pharmacokinetics of tocilizumab SC in GCA patients was determined using a population pharmacokinetic analysis on a dataset composed of 149 GCA patients treated with 162 mg subcutaneously every week or with 162 mg subcutaneously every other week.

For the 162 mg every week dose, the estimated median (range) steady-state Cmax, Ctrough and Cmean of tocilizumab SC were 72.1 (12.2–151) mcg/mL, 67.2 (10.7–145) mcg/mL, and 70.6 (11.7–149) mcg/mL, respectively. The accumulation ratios for Cmean or AUCtau, Ctrough, and Cmax were 10.9, 9.6, and 8.9, respectively. Steady state was reached after 17 weeks. For the 162 mg every other week dose, the estimated median (range) steady-state Cmax, Ctrough, and Cmean of tocilizumab were 17.2 (1.1–56.2) mcg/mL, 7.7 (0.1–37.3) mcg/mL, and 13.7 (0.5–49) mcg/mL, respectively. The accumulation ratios for Cmean or AUCtau, Ctrough, and Cmax were 2.8, 5.6, and 2.3 respectively. Steady-state was reached after 14 weeks.

The pharmacokinetics of tocilizumab IV in GCA patients was characterized by a non-compartmental pharmacokinetic analysis which included 22 patients treated with 6 mg/kg intravenously every 4 weeks for 20 weeks. The median (range) Cmax, Ctrough and Cmean of tocilizumab at steady state were 178 (115-320) mcg/mL, 22.7 (3.38-54.5) mcg/mL and 57.5 (32.9-110) mcg/mL, respectively. Steady state trough concentrations were within the range observed in GCA patients treated with 162 mg TCZ SC administered every week or every other week.

Based on pharmacokinetic exposure and extrapolation between RA and GCA patients, when given IV on a mg/kg basis, tocilizumab doses exceeding 600 mg per infusion are not recommended in patients with GCA [see Dosage and Administration (2.3)].

Systemic Sclerosis-Associated Interstitial Lung Disease – Subcutaneous Administration

The pharmacokinetics of tocilizumab in SSc-ILD patients was determined using a population pharmacokinetic analysis on a dataset composed of 66 SSc-ILD patients treated with 162 mg tocilizumab SC every week.

The estimated median (range) steady-state Cmax, Ctrough and Cmean of tocilizumab were 52.5 (14.8-121) mcg/mL, 47.2 (10.8-114) mcg/mL, and 50.4 (13.4-119) mcg/mL, respectively. The accumulation ratios for Cmean or AUCtau, Ctrough, and Cmax were 7.11, 6.56, and 5.89, respectively. Steady-state was reached after 13 weeks.

Polyarticular Juvenile Idiopathic Arthritis – Intravenous and Subcutaneous Administration

The pharmacokinetics of tocilizumab (TCZ) in PJIA patients was characterized by a population pharmacokinetic analysis which included 188 patients who were treated with TCZ IV or 52 patients treated with TCZ SC.

For doses of 8 mg/kg tocilizumab (patients with a body weight at or above 30 kg) given every 4 weeks intravenously, the estimated median (range) Cmax, Ctrough, and Cmean of tocilizumab at steady state were 181 (114–331) mcg/mL, 3.28 (0.02–35.4) mcg/mL, and 38.6 (22.2–83.8) mcg/mL, respectively. For doses of 10 mg/kg tocilizumab (patients with a body weight less than 30 kg) given every 4 weeks intravenously, the estimated median (range) Cmax, Ctrough, and Cmean of tocilizumab were 167 (125–220) mcg/mL, 0.35 (0–11.8) mcg/mL, and 30.8 (16.0–48.0) mcg/mL, respectively.

The accumulation ratios were 1.05 and 1.16 for AUC4weeks, and 1.43 and 2.22 for Ctrough for 10 mg/kg (BW less than 30 kg) and 8 mg/kg (BW at or above 30 kg) intravenous doses, respectively. No accumulation for Cmax was observed. Following 10 mg/kg and 8 mg/kg TCZ IV every 4 weeks doses in PJIA patients (aged 2 to 17 years), steady state concentrations (trough and average) were within the range of exposures in adult RA patients following 4 mg/kg and 8 mg/kg every 4 weeks, and steady state peak concentrations in PJIA patients were comparable to those following 8 mg/kg every 4 weeks in adult RA patients.

For doses of 162 mg tocilizumab (patients with a body weight at or above 30 kg) given every 2 weeks subcutaneously, the estimated median (range) Cmax, Ctrough, and Cmean of tocilizumab were 29.7 (7.56–50.3) mcg/mL, 12.7 (0.19–23.8) mcg/mL, and 23.0 (3.86–36.9) mcg/mL, respectively. For doses of 162 mg tocilizumab (patients with a body weight less than 30 kg) given every 3 weeks subcutaneously, the estimated median (range) Cmax, Ctrough, and Cmean of tocilizumab were 62.4 (39.4–121) mcg/mL, 13.4 (0.21–52.3) mcg/mL, and 35.7 (17.4–91.8) mcg/mL, respectively.

The accumulation ratios were 1.46 and 2.04 for AUC4weeks, 2.08 and 3.58 for Ctrough, and 1.32 and 1.72 for Cmax, for 162 mg given every 3 weeks (BW less than 30 kg) and 162 mg given every 2 weeks (BW at or above 30 kg) subcutaneous doses, respectively. Following subcutaneous dosing, steady state Ctrough was comparable for patients in the two body weight groups, while steady-state Cmax and Cmean were higher for patients in the less than 30 kg group compared to the group at or above 30 kg. All patients treated with TCZ SC had steady-state Ctrough at or higher than that achieved with TCZ IV across the spectrum of body weights. The average and trough concentrations in patients after subcutaneous dosing were within the range of those achieved in adult patients with RA following the subcutaneous administration of the recommended regimens.

Systemic Juvenile Idiopathic Arthritis – Intravenous and Subcutaneous Administration

The pharmacokinetics of tocilizumab (TCZ) in SJIA patients was characterized by a population pharmacokinetic analysis which included 89 patients who were treated with TCZ IV or 51 patients treated with TCZ SC.

For doses of 8 mg/kg tocilizumab (patients with a body weight at or above 30 kg) given every 2 weeks intravenously, the estimated median (range) Cmax, Ctrough, and Cmean of tocilizumab were 253 (120–404) mcg/mL, 70.7 (5.26–127) mcg/mL, and 117 (37.6–199) mcg/mL, respectively. For doses of 12 mg/kg tocilizumab (patients with a body weight less than 30 kg) given every 2 weeks intravenously, the estimated median (range) Cmax, Ctrough, and Cmean of tocilizumab were 274 (149–444) mcg/mL, 65.9 (19.0–135) mcg/mL, and 124 (60–194) mcg/mL, respectively.

The accumulation ratios were 1.95 and 2.01 for AUC4weeks, and 3.41 and 3.20 for Ctrough for 12 mg/kg (BW less than 30 kg) and 8 mg/kg (BW at or above 30 kg) intravenous doses, respectively. Accumulation data for Cmax were 1.37 and 1.42 for 12 mg/kg (BW less than 30 kg) and 8 mg/kg (BW at or above 30 kg) intravenous doses, respectively. Following every other week dosing with tocilizumab IV, steady state was reached by 8 weeks for both body weight groups. Mean estimated tocilizumab exposure parameters were similar between the two dose groups defined by body weight.

For doses of 162 mg tocilizumab (patients with a body weight at or above 30 kg) given every week subcutaneously, the estimated median (range) Cmax, Ctrough, and Cmean of tocilizumab were 89.8 (26.4–190) mcg/mL, 72.4 (19.5–158) mcg/mL, and 82.4 (23.9–169) mcg/mL, respectively. For doses of 162 mg tocilizumab (patients with a body weight less than 30 kg) given every 2 weeks subcutaneously, the estimated median (range) Cmax, Ctrough, and Cmean of tocilizumab were 127 (51.7–266) mcg/mL, 64.2 (16.6–136) mcg/mL, and 92.7 (38.5–199) mcg/mL, respectively.

The accumulation ratios were 2.27 and 4.28 for AUC4weeks, 3.21 and 4.39 for Ctrough, and 1.88 and 3.66 for Cmax, for 162 mg given every 2 weeks (BW less than 30 kg) and 162 mg given every week (BW at or above 30 kg) subcutaneous doses, respectively. Following subcutaneous dosing, steady state was reached by 12 weeks for both body weight groups. All patients treated with tocilizumab SC had steady-state Cmax lower than that achieved with tocilizumab IV across the spectrum of body weights. Trough and mean concentrations in patients after SC dosing were similar to those achieved with tocilizumab IV across body weights.

COVID-19 -Intravenous Administration

The pharmacokinetics of tocilizumab in adult COVID-19 patients was characterized by a population pharmacokinetic analysis of a dataset composed of 380 adult patients treated with tocilizumab 8mg/kg intravenously (IV) in the COVACTA study [see Clinical Studies (14.11)] and another clinical study.

For one dose of 8 mg/kg tocilizumab IV, the estimated median (range) Cmax and Cday28 of tocilizumab were 151 (77.5-319) mcg/mL and 0.229 (0.00119-19.4) mcg/mL, respectively. For two doses of 8 mg/kg tocilizumab IV separated by at least 8 hours, the estimated median (range) Cmax and Cday28 of tocilizumab was 290 (152-604) mcg/mL and 7.04 (0.00474-54.8) mcg/mL, respectively. The weight-tiered dosing used in RECOVERY study, 800 mg for patients >90 kg, 600 mg for patients >65 and ≤90 kg, 400 mg for patients >40 and ≤65 kg, and 8mg/kg for patients ≤40 kg, is comparable to 8 mg/kg dosing and is expected to have similar exposure.

Based on PK-sIL-6R modeling and simulation, the recommended dosing regimen for ACTEMRA is expected to result in comparable plasma exposures of tocilizumab in pediatric patients aged 2 years and older with COVID-19 as observed in adults with COVID-19 [see Use in Specific Populations (8.4)].

Absorption

Following subcutaneous dosing, the absorption half-life was around 4 days in RA and GCA patients and 3 days in SSc-ILD patients. The bioavailability for the subcutaneous formulation was 80%.

Following subcutaneous dosing in PJIA patients, the absorption half-life was around 2 days, and the bioavailability for the subcutaneous formulation in PJIA patients was 96%.

Following subcutaneous dosing in SJIA patients, the absorption half-life was around 2 days, and the bioavailability for the SC formulation in SJIA patients was 95%.

In RA patients the median values of Tmax were 2.8 days after the tocilizumab every week dose and 4.7 days after the tocilizumab every other week dose.

In GCA patients, the median values of Tmax were 3 days after the tocilizumab every week dose and 4.5 days after the tocilizumab every other week dose.

In SSc-ILD patients, the median value of Tmax was 2.8 days after the tocilizumab every week dose.

Distribution

Following intravenous dosing, tocilizumab undergoes biphasic elimination from the circulation. In rheumatoid arthritis patients the central volume of distribution was 3.5 L and the peripheral volume of distribution was 2.9 L, resulting in a volume of distribution at steady state of 6.4 L.

In GCA patients, the central volume of distribution was 4.09 L, the peripheral volume of distribution was 3.37 L resulting in a volume of distribution at steady state of 7.46 L.

In SSc-ILD patients, the central volume of distribution was 4.16 L, the peripheral volume of distribution was 2.58 L resulting in a volume of distribution at steady state of 6.74 L.

In pediatric patients with PJIA, the central volume of distribution was 1.98 L, the peripheral volume of distribution was 2.1 L, resulting in a volume of distribution at steady state of 4.08 L.

In pediatric patients with SJIA, the central volume of distribution was 1.87 L, the peripheral volume of distribution was 2.14 L resulting in a volume of distribution at steady state of 4.01 L.

In adult COVID-19 patients treated with one or two infusions of tocilizumab 8 mg/kg intravenously separated by 8 hours, the estimated central volume of distribution was 4.52 L, and the estimated peripheral volume of distribution was 4.23 L, resulting in a volume of distribution of 8.75 L.

Elimination

ACTEMRA is eliminated by a combination of linear clearance and nonlinear elimination. The concentration-dependent nonlinear elimination plays a major role at low tocilizumab concentrations. Once the nonlinear pathway is saturated, at higher tocilizumab concentrations, clearance is mainly determined by the linear clearance. The saturation of the nonlinear elimination leads to an increase in exposure that is more than dose-proportional. The pharmacokinetic parameters of ACTEMRA do not change with time.

Population pharmacokinetic analyses in any patient population tested so far indicate no relationship between apparent clearance and the presence of anti-drug antibodies.

The linear clearance in the population pharmacokinetic analysis was estimated to be 12.5 mL per h in RA patients, 6.7 mL per h in GCA patients, 8.8 mL per h in SSc-ILD patients, 5.8 mL per h in pediatric patients with PJIA, and 5.7 mL per h in pediatric patients with SJIA. In adult COVID-19 patients, serum concentrations were below the limit of quantification after 35 days on average following one infusion of tocilizumab 8 mg/kg intravenously. The average linear clearance in the population pharmacokinetic analysis was estimated to be 17.6 mL per hour in patients with baseline ordinal scale category 3 (OS 3, patients requiring supplemental oxygen), 22.5 mL per hour in patients with baseline OS 4 (patients requiring high-flow oxygen or non-invasive ventilation), 29 mL per hour in patients with baseline OS 5 (patients requiring mechanical ventilation), and 35.4 mL per hour in patients with baseline OS 6 (patients requiring extracorporeal membrane oxygenation (ECMO) or mechanical ventilation and additional organ support).

Due to the dependence of total clearance on ACTEMRA serum concentrations, the half-life of ACTEMRA is also concentration-dependent and varies depending on the serum concentration level.

For intravenous administration in RA patients, the concentration-dependent apparent t1/2 is up to 11 days for 4 mg per kg and up to 13 days for 8 mg per kg every 4 weeks in patients with RA at steady-state. For subcutaneous administration in RA patients, the concentration-dependent apparent t1/2 is up to 13 days for 162 mg every week and 5 days for 162 mg every other week in patients with RA at steady-state.

In GCA patients at steady state, the effective t1/2 of tocilizumab varied between 18.3 and 18.9 days for 162 mg subcutaneously every week dosing regimen and between 4.2 and 7.9 days for 162 mg subcutaneously every other week dosing regimen. For intravenous administration in GCA patients, the TCZ concentration-dependent apparent t1/2 was 13.2 days following 6 mg/kg every 4 weeks.

In SSc-ILD patients at steady state, the effective t1/2 of tocilizumab varied between 12.1 and 13.0 days for the 162 mg subcutaneous every week dosing regimen.

The t1/2 of tocilizumab in children with PJIA is up to 17 days for the two body weight categories (8 mg/kg for body weight at or above 30 kg or 10 mg/kg for body weight below 30 kg) during a dosing interval at steady state. For subcutaneous administration, the t1/2 of tocilizumab in PJIA patients is up to 10 days for the two body weight categories (every other week regimen for body weight at or above 30 kg or every 3 week regimen for body weight less than 30 kg) during a dosing interval at steady state.

The t1/2 of tocilizumab intravenous in pediatric patients with SJIA is up to 16 days for the two body weight categories (8 mg/kg for body weight at or above 30 kg and 12 mg/kg for body weight below 30 kg every other week) during a dosing interval at steady-state. Following subcutaneous administration, the effective t1/2 of tocilizumab subcutaneous in SJIA patients is up to 14 days for both the body weight categories (162 mg every week for body weight at or above 30 kg and 162 mg every two weeks for body weight below 30 kg) during a dosing interval at steady state.

Specific Populations

Population pharmacokinetic analyses in adult rheumatoid arthritis patients and GCA patients showed that age, gender and race did not affect the pharmacokinetics of tocilizumab. Linear clearance was found to increase with body size. In RA patients, the body weight-based dose (8 mg per kg) resulted in approximately 86% higher exposure in patients who are greater than 100 kg in comparison to patients who are less than 60 kg. There was an inverse relationship between tocilizumab exposure and body weight for flat dose subcutaneous regimens.

In GCA patients treated with ACTEMRA-SC, higher exposure was observed in patients with lower body weight. For the 162 mg every week subcutaneous dosing regimen, the steady-state Cmean was 51% higher in patients with body weight less than 60 kg compared to patients weighing between 60 to 100 kg. For the 162 mg every other week subcutaneous regimen, the steady-state Cmean was 129% higher in patients with body weight less than 60 kg compared to patients weighing between 60 to 100 kg. There is limited data for patients above 100 kg (n=7).

In COVID-19 patients, exposure following body-weight-based intravenous dosing (8 mg per kg tocilizumab up to 100 kg body weight with a maximum dose of 800 mg) was dependent on body weight and disease severity assessed by an ordinal scale (OS). Within an OS category, compared to patients with a mean body weight of 80 kg, exposure was 20% lower in patients weighing less than 60 kg. Exposure in patients weighing more than 100 kg was in the same range as exposure in patients with a mean body weight of 80 kg. For an 80 kg patient, exposure decreases as OS category increases; for each category increase, exposure decreases by 13%.

Patients with Hepatic Impairment

No formal study of the effect of hepatic impairment on the pharmacokinetics of tocilizumab was conducted.

Patients with Renal Impairment

No formal study of the effect of renal impairment on the pharmacokinetics of tocilizumab was conducted.

Most of the RA, GCA, and SSc-ILD patients in the population pharmacokinetic analysis had normal renal function or mild renal impairment. Mild renal impairment (estimated creatinine clearance less than 80 mL per min and at or above 50 mL per min based on Cockcroft-Gault formula) did not impact the pharmacokinetics of tocilizumab.

Approximately one-third of the patients in the ACTEMRA-SC GCA clinical trial had moderate renal impairment at baseline (estimated creatinine clearance of 30-59 mL/min). No impact on tocilizumab exposure was noted in these patients.

No dose adjustment is required in patients with mild or moderate renal impairment.

Drug Interaction Studies

In vitro data suggested that IL-6 reduced mRNA expression for several CYP450 isoenzymes including CYP1A2, CYP2B6, CYP2C9, CYP2C19, CYP2D6 and CYP3A4, and this reduced expression was reversed by co-incubation with tocilizumab at clinically relevant concentrations. Accordingly, inhibition of IL-6 signaling in RA patients treated with tocilizumab may restore CYP450 activities to higher levels than those in the absence of tocilizumab leading to increased metabolism of drugs that are CYP450 substrates. Its effect on CYP2C8 or transporters (e.g., P-gp) is unknown. This is clinically relevant for CYP450 substrates with a narrow therapeutic index, where the dose is individually adjusted. Upon initiation of ACTEMRA, in patients being treated with these types of medicinal products, therapeutic monitoring of the effect (e.g., warfarin) or drug concentration (e.g., cyclosporine or theophylline) should be performed and the individual dose of the medicinal product adjusted as needed. Caution should be exercised when ACTEMRA is coadministered with drugs where decrease in effectiveness is undesirable, e.g., oral contraceptives (CYP3A4 substrates) [see Drug Interactions (7.2)].

Simvastatin

Simvastatin is a CYP3A4 and OATP1B1 substrate. In 12 RA patients not treated with ACTEMRA, receiving 40 mg simvastatin, exposures of simvastatin and its metabolite, simvastatin acid, was 4- to 10-fold and 2-fold higher, respectively, than the exposures observed in healthy subjects. One week following administration of a single infusion of ACTEMRA (10 mg per kg), exposure of simvastatin and simvastatin acid decreased by 57% and 39%, respectively, to exposures that were similar or slightly higher than those observed in healthy subjects. Exposures of simvastatin and simvastatin acid increased upon withdrawal of ACTEMRA in RA patients. Selection of a particular dose of simvastatin in RA patients should take into account the potentially lower exposures that may result after initiation of ACTEMRA (due to normalization of CYP3A4) or higher exposures after discontinuation of ACTEMRA.

Omeprazole

Omeprazole is a CYP2C19 and CYP3A4 substrate. In RA patients receiving 10 mg omeprazole, exposure to omeprazole was approximately 2 fold higher than that observed in healthy subjects. In RA patients receiving 10 mg omeprazole, before and one week after ACTEMRA infusion (8 mg per kg), the omeprazole AUCinf decreased by 12% for poor (N=5) and intermediate metabolizers (N=5) and by 28% for extensive metabolizers (N=8) and were slightly higher than those observed in healthy subjects.

Dextromethorphan

Dextromethorphan is a CYP2D6 and CYP3A4 substrate. In 13 RA patients receiving 30 mg dextromethorphan, exposure to dextromethorphan was comparable to that in healthy subjects. However, exposure to its metabolite, dextrorphan (a CYP3A4 substrate), was a fraction of that observed in healthy subjects. One week following administration of a single infusion of ACTEMRA (8 mg per kg), dextromethorphan exposure was decreased by approximately 5%. However, a larger decrease (29%) in dextrorphan levels was noted after ACTEMRA infusion.

13 NONCLINICAL TOXICOLOGY

13.1 Carcinogenesis, Mutagenesis, Impairment of Fertility

No long-term animal studies have been performed to establish the carcinogenicity potential of tocilizumab. Literature indicates that the IL-6 pathway can mediate anti-tumor responses by promoting increased immune cell surveillance of the tumor microenvironment. However, available published evidence also supports that IL-6 signaling through the IL-6 receptor may be involved in pathways that lead to tumorigenesis. The malignancy risk in humans from an antibody that disrupts signaling through the IL-6 receptor, such as tocilizumab, is presently unknown.

Fertility and reproductive performance were unaffected in male and female mice that received a murine analogue of tocilizumab administered by the intravenous route at a dose of 50 mg/kg every three days.

14 CLINICAL STUDIES

14.1 Rheumatoid Arthritis – Intravenous Administration

The efficacy and safety of intravenously administered ACTEMRA was assessed in five randomized, double-blind, multicenter studies in patients greater than 18 years with active rheumatoid arthritis diagnosed according to American College of Rheumatology (ACR) criteria. Patients had at least 8 tender and 6 swollen joints at baseline. ACTEMRA was given intravenously every 4 weeks as monotherapy (Study I), in combination with methotrexate (MTX) (Studies II and III) or other disease-modifying anti-rheumatic drugs (DMARDs) (Study IV) in patients with an inadequate response to those drugs, or in combination with MTX in patients with an inadequate response to TNF antagonists (Study V).

Study I (NCT00109408) evaluated patients with moderate to severe active rheumatoid arthritis who had not been treated with MTX within 24 weeks prior to randomization, or who had not discontinued previous methotrexate treatment as a result of clinically important toxic effects or lack of response. In this study, 67% of patients were MTX-naïve, and over 40% of patients had rheumatoid arthritis less than 2 years. Patients received ACTEMRA 8 mg per kg monotherapy or MTX alone (dose titrated over 8 weeks from 7.5 mg to a maximum of 20 mg weekly). The primary endpoint was the proportion of ACTEMRA patients who achieved an ACR 20 response at Week 24.

Study II (NCT00106535) was a 104-week study with an optional 156-week extension phase that evaluated patients with moderate to severe active rheumatoid arthritis who had an inadequate clinical response to MTX. Patients received ACTEMRA 8 mg per kg, ACTEMRA 4 mg per kg, or placebo every four weeks, in combination with MTX (10 to 25 mg weekly). Upon completion of 52-weeks, patients received open-label treatment with ACTEMRA 8 mg per kg through 104 weeks or they had the option to continue their double-blind treatment if they maintained a greater than 70% improvement in swollen/tender joint count. Two pre-specified interim analyses at week 24 and week 52 were conducted. The primary endpoint at week 24 was the proportion of patients who achieved an ACR 20 response. At weeks 52 and 104, the primary endpoints were change from baseline in modified total Sharp-Genant score and the area under the curve (AUC) of the change from baseline in HAQ-DI score.

Study III (NCT00106548) evaluated patients with moderate to severe active rheumatoid arthritis who had an inadequate clinical response to MTX. Patients received ACTEMRA 8 mg per kg, ACTEMRA 4 mg per kg, or placebo every four weeks, in combination with MTX (10 to 25 mg weekly). The primary endpoint was the proportion of patients who achieved an ACR 20 response at week 24.

Study IV (NCT00106574) evaluated patients who had an inadequate response to their existing therapy, including one or more DMARDs. Patients received ACTEMRA 8 mg per kg or placebo every four weeks, in combination with the stable DMARDs. The primary endpoint was the proportion of patients who achieved an ACR 20 response at week 24.

Study V (NCT00106522) evaluated patients with moderate to severe active rheumatoid arthritis who had an inadequate clinical response or were intolerant to one or more TNF antagonist therapies. The TNF antagonist therapy was discontinued prior to randomization. Patients received ACTEMRA 8 mg per kg, ACTEMRA 4 mg per kg, or placebo every four weeks, in combination with MTX (10 to 25 mg weekly). The primary endpoint was the proportion of patients who achieved an ACR 20 response at week 24.

Clinical Response

The percentages of intravenous ACTEMRA-treated patients achieving ACR 20, 50 and 70 responses are shown in Table 4. In all intravenous studies, patients treated with 8 mg per kg ACTEMRA had higher ACR 20, ACR 50, and ACR 70 response rates versus MTX- or placebo-treated patients at week 24.

During the 24 week controlled portions of Studies I to V, patients treated with ACTEMRA at a dose of 4 mg per kg in patients with inadequate response to DMARDs or TNF antagonist therapy had lower response rates compared to patients treated with ACTEMRA 8 mg per kg.

Table 4 Clinical Response at Weeks 24 and 52 in Active and Placebo Controlled Trials of Intravenous ACTEMRA (Percent of Patients)
Percent of Patients
Response Rate | Study I |  | Study II |  |  | Study III |  |  | Study IV |  | Study V
Response Rate | MTX | ACTEMRA 8 mg per kg | Placebo + MTX | ACTEMRA 4 mg per kg + MTX | ACTEMRA 8 mg per kg + MTX | Placebo + MTX | ACTEMRA 4 mg per kg + MTX | ACTEMRA 8 mg per kg + MTX | Placebo + DMARDs | ACTEMRA 8 mg per kg + DMARDs | Placebo + MTX | ACTEMRA 4 mg per kg + MTX | ACTEMRA 8 mg per kg + MTX
Response Rate | N=284 | N=286 | N=393 | N=399 | N=398 | N=204 | N=213 | N=205 | N=413 | N=803 | N=158 | N=161 | N=170
Response Rate |  | (95% CI) [CI: 95% confidence interval of the weighted difference to placebo adjusted for site (and disease duration for Study I only)] |  | (95% CI) | (95% CI) |  | (95% CI) | (95% CI) |  | (95% CI) |  | (95% CI) | (95% CI)
ACR 20
Week 24 | 53% | 70% (0.11, 0.27) | 27% | 51% (0.17, 0.29) | 56% (0.23, 0.35) | 27% | 48% (0.15, 0.32) | 59% (0.23, 0.41) | 24% | 61% (0.30, 0.40) | 10% | 30% (0.15, 0.36) | 50% (0.36, 0.56)
Week 52 | N/A | N/A | 25% | 47% (0.15, 0.28) | 56% (0.25, 0.38) | N/A | N/A | N/A | N/A | N/A | N/A | N/A | N/A
ACR 50
Week 24 | 34% | 44% (0.04, 0.20) | 10% | 25% (0.09, 0.20) | 32% (0.16, 0.28) | 11% | 32% (0.13, 0.29) | 44% (0.25, 0.41) | 9% | 38% (0.23, 0.33) | 4% | 17% (0.05, 0.25) | 29% (0.21, 0.41)
Week 52 | N/A | N/A | 10% | 29% (0.14, 0.25) | 36% (0.21, 0.32) | N/A | N/A | N/A | N/A | N/A | N/A | N/A | N/A
ACR 70
Week 24 | 15% | 28% (0.07, 0.22) | 2% | 11% (0.03, 0.13) | 13% (0.05, 0.15) | 2% | 12% (0.04, 0.18) | 22% (0.12, 0.27) | 3% | 21% (0.13, 0.21) | 1% | 5% (-0.06, 0.14) | 12% (0.03, 0.22)
Week 52 | N/A | N/A | 4% | 16% (0.08, 0.17) | 20% (0.12, 0.21) | N/A | N/A | N/A | N/A | N/A | N/A | N/A | N/A
Major Clinical Responses [Major clinical response is defined as achieving an ACR 70 response for a continuous 24 week period]
Week 52 | N/A | N/A | 1% | 4% (0.01, 0.06) | 7% (0.03, 0.09) | N/A | N/A | N/A | N/A | N/A | N/A | N/A | N/A

In study II, a greater proportion of patients treated with 4 mg per kg and 8 mg per kg ACTEMRA + MTX achieved a low level of disease activity as measured by a DAS 28-ESR less than 2.6 compared with placebo +MTX treated patients at week 52. The proportion of ACTEMRA-treated patients achieving DAS 28-ESR less than 2.6, and the number of residual active joints in these responders in Study II are shown in Table 5.

Table 5 Proportion of Patients with DAS28-ESR Less Than 2.6 with Number of Residual Active Joints in Trials of Intravenous ACTEMRA
Study II
 | Placebo + MTX N = 393 | ACTEMRA 4 mg per kg + MTX N = 399 | ACTEMRA 8 mg per kg + MTX N = 398
DAS28-ESR less than 2.6
Proportion of responders at week 52 (n) 95% confidence interval | 3% (12) | 18% (70) 0.10, 0.19 | 32% (127) 0.24, 0.34
Of responders, proportion with 0 active joints (n) | 33% (4) | 27% (19) | 21% (27)
Of responders, proportion with 1 active joint (n) | 8% (1) | 19% (13) | 13% (16)
Of responders, proportion with 2 active joints (n) | 25% (3) | 13% (9) | 20% (25)
Of responders, proportion with 3 or more active joints (n) | 33% (4) | 41% (29) | 47% (59)
*n denotes numerator of all the percentage. Denominator is the intent-to-treat population. Not all patients received DAS28 assessments at Week 52.

The results of the components of the ACR response criteria for Studies III and V are shown in Table 6. Similar results to Study III were observed in Studies I, II and IV.

Table 6 Components of ACR Response at Week 24 in Trials of Intravenous ACTEMRA
 | Study III |  |  |  |  |  | Study V
 | ACTEMRA 4 mg per kg + MTX |  | ACTEMRA 8 mg per kg + MTX |  | Placebo + MTX |  | ACTEMRA 4 mg per kg + MTX |  | ACTEMRA 8 mg per kg + MTX |  | Placebo + MTX
 | N=213 |  | N=205 |  | N=204 |  | N=161 |  | N=170 |  | N=158
Component (mean) | Baseline | Week 24 [Data shown is mean at week 24, difference in adjusted mean change from baseline compared with placebo + MTX at week 24 and 95% confidence interval for that difference] | Baseline | Week 24 | Baseline | Week 24 | Baseline | Week 24 | Baseline | Week 24 | Baseline | Week 24
Number of tender joints (0-68) | 33 | 19 -7.0 (-10.0, -4.1) | 32 | 14.5 -9.6 (-12.6, -6.7) | 33 | 25 | 31 | 21 -10.8 (-14.6, -7.1) | 32 | 17 -15.1 (-18.8, -11.4) | 30 | 30
Number of swollen joints (0-66) | 20 | 10 -4.2 (-6.1, -2.3) | 19.5 | 8 -6.2 (-8.1, -4.2) | 21 | 15 | 19.5 | 13 -6.2 (-9.0, -3.5) | 19 | 11 -7.2 (-9.9, -4.5) | 19 | 18
Pain [Visual analog scale: 0 = best, 100 = worst] | 61 | 33 -11.0 (-17.0, -5.0) | 60 | 30 -15.8 (-21.7, -9.9) | 57 | 43 | 63.5 | 43 -12.4 (-22.1, -2.1) | 65 | 33 -23.9 (-33.7, -14.1) | 64 | 48
Patient global assessment | 66 | 34 -10.9 (-17.1, -4.8) | 65 | 31 -14.9 (-20.9, -8.9) | 64 | 45 | 70 | 46 -10.0 (-20.3, 0.3) | 70 | 36 -17.4 (-27.8, -7.0) | 71 | 51
Physician global assessment | 64 | 26 -5.6 (-10.5, -0.8) | 64 | 23 -9.0 (-13.8, -4.2) | 64 | 32 | 66.5 | 39 -10.5 (-18.6, -2.5) | 66 | 28 -18.2 (-26.3, -10.0) | 67.5 | 43
Disability index (HAQ) [Health Assessment Questionnaire: 0 = best, 3 = worst; 20 questions; 8 categories: dressing and grooming, arising, eating, walking, hygiene, reach, grip, and activities] | 1.64 | 1.01 -0.18 (-0.34, -0.02) | 1.55 | 0.96 -0.21 (-0.37, -0.05) | 1.55 | 1.21 | 1.67 | 1.39 -0.25 (-0.42, -0.09) | 1.75 | 1.34 -0.34 (-0.51, -0.17) | 1.70 | 1.58
CRP (mg per dL) | 2.79 | 1.17 -1.30 (-2.0, -0.59) | 2.61 | 0.25 -2.156 (-2.86, -1.46) | 2.36 | 1.89 | 3.11 | 1.77 -1.34 (-2.5, -0.15) | 2.80 | 0.28 -2.52 (-3.72, -1.32) | 3.705 | 3.06

The percent of ACR 20 responders by visit for Study III is shown in Figure 1. Similar response curves were observed in studies I, II, IV, and V.

Figure 1 Percent of ACR 20 Responders by Visit for Study III (Inadequate Response to MTX) [The same patients may not have responded at each timepoint.]

Radiographic Response

In Study II, structural joint damage was assessed radiographically and expressed as change in total Sharp-Genant score and its components, the erosion score and joint space narrowing score. Radiographs of hands/wrists and forefeet were obtained at baseline, 24 weeks, 52 weeks, and 104 weeks and scored by readers unaware of treatments group and visit number. The results from baseline to week 52 are shown in Table 7. ACTEMRA 4 mg per kg slowed (less than 75% inhibition compared to the control group) and ACTEMRA 8 mg per kg inhibited (at least 75% inhibition compared to the control group) the progression of structural damage compared to placebo plus MTX at week 52.

Table 7 Mean Radiographic Change from Baseline to Week 52 in Study II
 | Placebo + MTX | ACTEMRA 4 mg per kg + MTX | ACTEMRA 8 mg per kg + MTX
 | N=294 | N=343 | N=353
Week 52 [Week 52 analysis employs linearly extrapolated data for patients after escape, withdrawal, or loss to follow up.]
Total Sharp-Genant Score, Mean (SD) | 1.17 (3.14) | 0.33 (1.30) | 0.25 (0.98)
Adjusted Mean difference [Difference between the adjusted means (ACTEMRA + MTX - Placebo + MTX)] (95%CI) |  | -0.83 (-1.13, -0.52) | -0.90 (-1.20, -0.59)
Erosion Score, Mean (SD) | 0.76 (2.14) | 0.20 (0.83) | 0.15 (0.77)
Adjusted Mean difference (95%CI) |  | -0.55 (-0.76, -0.34) | -0.60 (-0.80, -0.39)
Joint Space Narrowing Score, Mean (SD) | 0.41 (1.71) | 0.13 (0.72) | 0.10 (0.49)
Adjusted Mean difference (95%CI) |  | -0.28 (-0.44, -0.11) | -0.30 (-0.46, -0.14)
SD = standard deviation

The mean change from baseline to week 104 in Total Sharp-Genant Score for the ACTEMRA 4 mg per kg groups was 0.47 (SD = 1.47) and for the 8 mg per kg groups was 0.34 (SD = 1.24). By the week 104, most patients in the control (placebo + MTX) group had crossed over to active treatment, and results are therefore not included for comparison. Patients in the active groups may have crossed over to the alternate active dose group, and results are reported per original randomized dose group.

In the placebo group, 66% of patients experienced no radiographic progression (Total Sharp-Genant Score change ≤ 0) at week 52 compared to 78% and 83% in the ACTEMRA 4 mg per kg and 8 mg per kg, respectively. Following 104 weeks of treatment, 75% and 83% of patients initially randomized to ACTEMRA 4 mg per kg and 8 mg per kg, respectively, experienced no progression of structural damage compared to 66% of placebo treated patients.

Health Related Outcomes

In Study II, physical function and disability were assessed using the Health Assessment Questionnaire Disability Index (HAQ-DI). Both dosing groups of ACTEMRA demonstrated a greater improvement compared to the placebo group in the AUC of change from baseline in the HAQ-DI through week 52. The mean change from baseline to week 52 in HAQ-DI was 0.6, 0.5, and 0.4 for ACTEMRA 8 mg per kg, ACTEMRA 4 mg per kg, and placebo treatment groups, respectively. Sixty-three percent (63%) and sixty percent (60%) of patients in the ACTEMRA 8 mg per kg and ACTEMRA 4 mg per kg treatment groups, respectively, achieved a clinically relevant improvement in HAQ-DI (change from baseline of ≥ 0.3 units) at week 52 compared to 53% in the placebo treatment group.

Other Health-Related Outcomes

General health status was assessed by the Short Form Health Survey (SF-36) in Studies I – V. Patients receiving ACTEMRA demonstrated greater improvement from baseline compared to placebo in the Physical Component Summary (PCS), Mental Component Summary (MCS), and in all 8 domains of the SF-36.

Cardiovascular Outcomes

Study WA25204 (NCT01331837) was a randomized, open-label (sponsor-blinded), 2-arm parallel-group, multicenter, non-inferiority, cardiovascular (CV) outcomes trial in patients with a diagnosis of moderate to severe RA. This CV safety study was designed to exclude a moderate increase in CV risk in patients treated with ACTEMRA compared with a TNF inhibitor standard of care (etanercept).

The study included 3,080 seropositive RA patients with active disease and an inadequate response to non-biologic disease-modifying anti-rheumatic drugs, who were aged ≥50 years with at least one additional CV risk factor beyond RA. Patients were randomized 1:1 to IV ACTEMRA 8 mg/kg Q4W or SC etanercept 50 mg QW and followed for an average of 3.2 years. The primary endpoint was the comparison of the time-to-first occurrence of any component of a composite of major adverse CV events (MACE; non-fatal myocardial infarction, non-fatal stroke, or CV death), with the final intent-to-treat analysis based on a total of 161 confirmed CV events (83/1538 [5.4%] for ACTEMRA; 78/1542 [5.1%] for etanercept) reviewed by an independent and blinded adjudication committee.

Non-inferiority of ACTEMRA to etanercept for cardiovascular risk was determined by excluding >80% relative increase in the risk of MACE. The estimated hazard ratio (HR) for the risk of MACE comparing ACTEMRA to etanercept was 1.05; 95% CI (0.77, 1.43).

14.2 Rheumatoid Arthritis – Subcutaneous Administration

The efficacy and safety of subcutaneously administered ACTEMRA was assessed in two double-blind, controlled, multicenter studies in patients with active RA. One study, SC-I (NCT01194414), was a non-inferiority study that compared the efficacy and safety of ACTEMRA 162 mg administered every week subcutaneously to 8 mg per kg intravenously every four weeks. The second study, SC-II (NCT01232569), was a placebo controlled superiority study that evaluated the safety and efficacy of ACTEMRA 162 mg administered every other week subcutaneously to placebo. Both SC-I and SC-II required patients to be >18 years of age with moderate to severe active rheumatoid arthritis diagnosed according to ACR criteria who had at least 4 tender and 4 swollen joints at baseline (SC-I) or at least 8 tender and 6 swollen joints at baseline (SC-II), and an inadequate response to their existing DMARD therapy, where approximately 20% also had a history of inadequate response to at least one TNF inhibitor. All patients in both SC studies received background non-biologic DMARD(s).

In SC-I, 1262 patients were randomized 1:1 to receive ACTEMRA-SC 162 mg every week or intravenous ACTEMRA 8 mg/kg every four weeks in combination with DMARD(s). In SC-II, 656 patients were randomized 2:1 to ACTEMRA-SC 162 mg every other week or placebo, in combination with DMARD(s). The primary endpoint in both studies was the proportion of patients who achieved an ACR20 response at Week 24.

The clinical response to 24 weeks of ACTEMRA-SC therapy is shown in Table 8. In SC-I, the primary outcome measure was ACR20 at Week 24. The pre-specified non-inferiority margin was a treatment difference of 12%. The study demonstrated non-inferiority of ACTEMRA with respect to ACR20 at Week 24; ACR50, ACR70, and DAS28 responses are also shown in Table 8. In SC-II, a greater portion of patients treated with ACTEMRA 162 mg subcutaneously every other week achieved ACR20, ACR50, and ACR70 responses compared to placebo-treated patients (Table 8). Further, a greater proportion of patients treated with ACTEMRA 162 mg subcutaneously every other week achieved a low level of disease activity as measured by a DAS28-ESR less than 2.6 at Week 24 compared to those treated with placebo (Table 8).

Table 8 Clinical Response at Week 24 in Trials of Subcutaneous ACTEMRA (Percent of Patients)
 | SC-I [Per Protocol Population] |  | SC-II [Intent To Treat Population]
 | TCZ SC 162 mg every week + DMARD | TCZ IV 8mg/kg + DMARD | TCZ SC 162 mg every other week + DMARD | Placebo + DMARD
 | N=558 | N=537 | N=437 | N=219
ACR20
Week 24 | 69% | 73.4% | 61% | 32%
Weighted difference (95% CI) | -4% (-9.2, 1.2) |  | 30% (22.0, 37.0)
ACR50
Week 24 | 47% | 49% | 40% | 12%
Weighted difference (95% CI) | -2% (-7.5, 4.0) |  | 28% (21.5, 34.4)
ACR70
Week 24 | 24% | 28% | 20% | 5%
Weighted difference (95% CI) | -4% (-9.0, 1.3) |  | 15% (9.8, 19.9)
Change in DAS28 [Adjusted mean]
Week 24 | -3.5 | -3.5 | -3.1 | -1.7
Adjusted mean difference (95% CI) | 0 (-0.2, 0.1) |  | -1.4 (-1.7; -1.1)
DAS28 < 2.6
Week 24 | 38.4% | 36.9% | 32.0% | 4.0%
Weighted difference (95% CI) | 0.9 (-5.0, 6.8) |  | 28.6 (22.0, 35.2)
TCZ = tocilizumab

The results of the components of the ACR response criteria and the percent of ACR20 responders by visit for ACTEMRA-SC in Studies SC-I and SC-II were consistent with those observed for ACTEMRA-IV.

Radiographic Response

In study SC-II, the progression of structural joint damage was assessed radiographically and expressed as a change from baseline in the van der Heijde modified total Sharp score (mTSS). At week 24, significantly less radiographic progression was observed in patients receiving ACTEMRA-SC every other week plus DMARD(s) compared to placebo plus DMARD(s); mean change from baseline in mTSS of 0.62 vs. 1.23, respectively, with an adjusted mean difference of -0.60 (-1.1, -0.1). These results are consistent with those observed in patients treated with intravenous ACTEMRA.

Health Related Outcomes

In studies SC-I and SC-II, the mean decrease from baseline to week 24 in HAQ-DI was 0.6, 0.6, 0.4 and 0.3, and the proportion of patients who achieved a clinically relevant improvement in HAQ-DI (change from baseline of ≥ 0.3 units) was 65%, 67%, 58% and 47%, for the subcutaneous every week, intravenous 8 mg/kg, subcutaneous every other week, and placebo treatment groups, respectively.

Other Health-Related Outcomes

General health status was assessed by the SF-36 in Studies SC-I and SC-II. In Study SC-II, patients receiving ACTEMRA every other week demonstrated greater improvement from baseline compared to placebo in the PCS, MCS, and in all 8 domains of the SF-36. In Study SC-I, improvements in these scores were similar between ACTEMRA-SC every week and ACTEMRA-IV 8 mg/kg.

14.3 Giant Cell Arteritis – Subcutaneous Administration

The efficacy and safety of subcutaneously administered ACTEMRA was assessed in a single, randomized, double-blind, multicenter study in patients with active GCA. In Study WA28119 (NCT01791153), 251 screened patients with new-onset or relapsing GCA were randomized to one of four treatment arms. Two subcutaneous doses of ACTEMRA (162 mg every week and 162 mg every other week) were compared to two different placebo control groups (pre-specified prednisone-taper regimen over 26 weeks and 52 weeks) randomized 2:1:1:1. The study consisted of a 52-week blinded period, followed by a 104-week open-label extension.

All patients received background glucocorticoid (prednisone) therapy. Each of the ACTEMRA-treated groups and one of the placebo-treated groups followed a pre-specified prednisone-taper regimen with the aim to reach 0 mg by 26 weeks, while the second placebo-treated group followed a pre-specified prednisone-taper regimen with the aim to reach 0 mg by 52 weeks designed to be more in keeping with standard practice.

The primary efficacy endpoint was the proportion of patients achieving sustained remission from Week 12 through Week 52. Sustained remission was defined by a patient attaining a sustained (1) absence of GCA signs and symptoms from Week 12 through Week 52, (2) normalization of erythrocyte sedimentation rate (ESR) (to < 30 mm/hr without an elevation to ≥ 30 mm/hr attributable to GCA) from Week 12 through Week 52, (3) normalization of C-reactive protein (CRP) (to < 1 mg/dL, with an absence of successive elevations to ≥ 1mg/dL) from Week 12 through Week 52, and (4) successful adherence to the prednisone taper defined by not more than 100 mg of excess prednisone from Week 12 through Week 52. ACTEMRA 162 mg weekly and 162 mg every other week + 26 weeks prednisone taper both showed superiority in achieving sustained remission from Week 12 through Week 52 compared with placebo + 26 weeks prednisone taper (Table 9). Both ACTEMRA treatment arms also showed superiority compared to the placebo + 52 weeks prednisone taper (Table 9).

Table 9 Efficacy Results from Study WA28119
 | PBO + 26 weeks prednisone taper N=50 | PBO + 52 weeks prednisone taper N=51 | TCZ 162mg SC QW + 26 weeks prednisone taper N=100 | TCZ 162 mg SC Q2W + 26 weeks prednisone taper N=49
Sustained remission [Sustained remission was achieved by a patient meeting all of the following components: absence of GCA signs and symptoms†, normalization of ESR‡, normalization of CRP§ and adherence to the prednisone taper regimen¶.]
Responders, n (%) | 7 (14.0%) | 9 (17.6%) | 56 (56.0%) | 26 (53.1%)
Unadjusted difference in proportions vs PBO + 26 weeks taper (99.5% CI) | N/A | N/A | 42.0% (18.0, 66.0) | 39.1% (12.5 , 65.7)
Unadjusted difference in proportions vs PBO + 52 weeks taper (99.5% CI) | N/A | N/A | 38.4% (14.4, 62.3) | 35.4% (8.6, 62.2)
Components of Sustained Remission
Sustained absence of GCA signs and symptoms [Patients who did not have any signs or symptoms of GCA recorded from Week 12 up to Week 52.] , n (%) | 20 (40.0%) | 23 (45.1%) | 69 (69.0%) | 28 (57.1%)
Sustained ESR<30 mm/hr [Patients who did not have an elevated ESR ≥30 mm/hr which was classified as attributed to GCA from Week 12 up to Week 52.] , n (%) | 20 (40.0%) | 22 (43.1%) | 83 (83.0%) | 37 (75.5%)
Sustained CRP normalization [Patients who did not have two or more consecutive CRP records of ≥ 1mg/dL from Week 12 up to Week 52.] , n (%) | 17 (34.0%) | 13 (25.5%) | 72 (72.0%) | 34 (69.4%)
Successful prednisone tapering [Patients who did not enter escape therapy and received ≤ 100mg of additional concomitant prednisone from Week 12 up to Week 52.] , n (%) | 10 (20.0%) | 20 (39.2%) | 60 (60.0%) | 28 (57.1%)
Patients not completing the study to week 52 were classified as non-responders in the primary and key secondary analysis: PBO+26: 6 (12.0%), PBO+52: 5 (9.8%), TCZ QW: 15 (15.0%), TCZ Q2W: 9 (18.4%).
CRP = C-reactive protein
ESR = erythrocyte sedimentation rate
PBO = placebo
Q2W = every other week dose
QW = every week dose
TCZ = tocilizumab

The estimated annual cumulative prednisone dose was lower in the two ACTEMRA dose groups (medians of 1887 mg and 2207 mg on ACTEMRA QW and Q2W, respectively) relative to the placebo arms (medians of 3804 mg and 3902 mg on placebo + 26 weeks prednisone and placebo + 52 weeks prednisone taper, respectively).

14.4 Giant Cell Arteritis – Intravenous Administration

Intravenously administered ACTEMRA in patients with GCA was assessed in WP41152 (NCT03923738), an open-label PK-PD and safety study to determine the appropriate intravenous dose of ACTEMRA that achieved comparable PK-PD profiles to the ACTEMRA-SC regimen.

At enrollment, all patients (n=24) were in remission on ACTEMRA-IV. In Period 1, all patients received open-label ACTEMRA-IV 7 mg/kg every 4 weeks for 20 weeks. Patients who completed Period 1 and remained in remission (n=22) were eligible to enter Period 2, and received open-label ACTEMRA-IV 6 mg/kg every 4 weeks for 20 weeks.

The efficacy of intravenous ACTEMRA 6 mg/kg in adult patients with GCA is based on pharmacokinetic exposure and extrapolation to the efficacy established for subcutaneous ACTEMRA in patients with GCA [see Clinical Pharmacology (12.3) and Clinical Studies (14.3)].

14.5 Systemic Sclerosis-Associated Interstitial Lung Disease– Subcutaneous Administration

The clinical efficacy of ACTEMRA was assessed in a phase 3 multicenter, randomized, double-blind, placebo controlled study in patients with SSc (Study WA29767). A phase 2/3 multicenter, randomized, double-blind, placebo controlled study in patients with SSc (Study WA27788) provided supportive information. Study WA29767 (NCT02453256) enrolled adult patients with SSc defined by the 2013 American College of Rheumatology/European League Against Rheumatism classification criteria for SSc, with onset of disease (first non-Raynaud symptom) of ≤ 5 years, modified Rodnan Skin Score (mRSS) of ≥ 10 and ≤ 35 at screening, elevated inflammatory markers (or platelets), and active disease based on at least one of the following: disease duration ≤ 18 months, increase in mRSS ≥ 3 units over 6 months, involvement of one new body area and an increase in mRSS of ≥ 2 over 6 months, or involvement of two new body areas within the previous 6 months, or presence of at least one tendon friction rub. Study WA27788 (NCT01532869) enrolled adult patients with SSc with onset of disease ≤ 5 years, mRSS of ≥ 15 and ≤ 40 at screening, active disease, and elevated inflammatory markers or platelets. Patients in both studies were not permitted to use biologic agents (such as TNF antagonists), alkylating agents, or cyclophosphamide.

In Study WA29767, 212 patients were randomized in a 1:1 ratio to receive weekly SC injections of 162 mg of ACTEMRA or placebo during the 48-week, double-blinded, placebo controlled period. Rescue treatment was allowed during the treatment period after 16 weeks for >10% percent predicted FVC (ppFVC) decline or after 24 weeks for worsening skin fibrosis. The primary efficacy endpoint was change from baseline at Week 48 in mRSS. Change from baseline in FVC at Week 48 was a key secondary endpoint.

In the overall population of Study WA29767, there was not a statistically significant difference in the mean change from baseline to Week 48 in mRSS (primary endpoint) in patients receiving ACTEMRA compared to placebo (difference: -1.73; 95% CI: -3.78, 0.32). There also was not a statistically significant effect on the primary endpoint of mRSS in Study WA27788.

In the overall population of Study WA29767, patients treated with ACTEMRA, as compared to placebo treated patients, were observed to have less decline from baseline in ppFVC and observed FVC at 48 weeks. FVC results from Study WA27788 were similar.

Of the 212 patients who were randomized in Study WA29767, 68 patients (65%) in the ACTEMRA arm and 68 patients (64%) in the placebo arm had SSc-ILD at baseline, as confirmed by a visual read of high resolution computed tomograph (HRCT) by blinded thoracic radiologists. The mean ppFVC at baseline for patients with SSc-ILD identified by HRCT was 79.6% (median 80.5%). Post-hoc analyses were performed to evaluate results within the subgroups of patients with and without SSc-ILD.

Table 10 shows results from Study WA29767 for the changes from baseline to Week 48 in ppFVC, observed FVC, and mRSS both in the overall population and within subgroups based on SSc-ILD status at baseline. The ppFVC and observed FVC results in the overall population were primarily driven by results in the SSc-ILD subgroup. In the SSc-ILD subgroup, the differences in mean changes from baseline to Week 48 for ACTEMRA, as compared to placebo, were 6.47% and 241 mL for ppFVC and observed FVC, respectively. Figure 2 illustrates the mean change from baseline through Week 48 in observed FVC in patients with SSc-ILD.

The results of the key FVC secondary endpoints from Study WA29767 support a conclusion of effectiveness of ACTEMRA in reducing the rate of progressive loss of lung function in the study population. However, in settings where a trial does not provide evidence of an effect on the primary endpoint, the estimated magnitude of effect on other endpoints should be interpreted with caution, and comparisons to results of other products and studies may be misleading.

Table 10 Efficacy Results from Study WA29767
 | Overall Population |  | Subgroup Without SSc-ILD [Post-hoc results are shown for these subgroups. Four patients had ILD status missing at baseline.] |  | SSc-ILD Subgroup
 | PBO QW | TCZ 162 mg QW | PBO QW | TCZ 162 mg QW | PBO QW | TCZ 162 mg QW
Number of patients | 106 | 104 | 36 | 34 | 68 | 68
Change from Baseline in mRSS at Week 48
LSM | -4.41 | -6.14 | -6.16 | -8.56 | -3.77 | -5.88
Difference in LSM, TCZ-placebo (95% CI) | -1.73 (-3.78, 0.32) |  | -2.40 (-5.59, 0.79) |  | -2.11 (-4.89, 0.67)
Change from Baseline in ppFVC at Week 48
LSM | -4.58 | -0.38 | -0.82 | -0.32 | -6.40 | 0.07
Difference in LSM, TCZ-placebo (95% CI) | 4.20 (2.00, 6.40) |  | 0.50 (-2.27, 3.27) |  | 6.47 (3.43, 9.50)
Change from Baseline in Observed FVC (mL) at Week 48
LSM | -190 | -24 | -53 | -11 | -255 | -14
Difference in LSM, TCZ-placebo (95% CI) | 167 (83, 250) |  | 43 (-60, 145) |  | 241 (124, 358)
PBO=placebo; TCZ=tocilizumab; ppFVC = percent predicted forced vital capacity; LSM=least squares mean; mRSS = modified Rodnan skin score; CI=confidence interval

Figure 2 Mean Change from Baseline to Week 48 in Observed Forced Vital Capacity in SSc-ILD Patients from Study WA29767

PBO = placebo; TCZ = tocilizumab; QW = every week dose

14.6 Polyarticular Juvenile Idiopathic Arthritis – Intravenous Administration

The efficacy of ACTEMRA was assessed in a three-part study, WA19977 (NCT00988221), including an open-label extension in children 2 to 17 years of age with active polyarticular juvenile idiopathic arthritis (PJIA), who had an inadequate response to methotrexate or inability to tolerate methotrexate. Patients had at least 6 months of active disease (mean disease duration of 4.2 ± 3.7 years), with at least five joints with active arthritis (swollen or limitation of movement accompanied by pain and/or tenderness) and/or at least 3 active joints having limitation of motion (mean, 20 ± 14 active joints). The patients treated had subtypes of JIA that at disease onset included Rheumatoid Factor Positive or Negative Polyarticular JIA, or Extended Oligoarticular JIA. Treatment with a stable dose of methotrexate was permitted but was not required during the study. Concurrent use of disease modifying antirheumatic drugs (DMARDs), other than methotrexate, or other biologics (e.g., TNF antagonists or T cell costimulation modulator) were not permitted in the study.

Part I consisted of a 16-week active ACTEMRA treatment lead-in period (n=188) followed by Part II, a 24-week randomized double-blind placebo-controlled withdrawal period, followed by Part III, a 64-week open-label period. Eligible patients weighing at or above 30 kg received ACTEMRA at 8 mg/kg intravenously once every four weeks. Patients weighing less than 30 kg were randomized 1:1 to receive either ACTEMRA 8 mg/kg or 10 mg/kg intravenously every four weeks. At the conclusion of the open-label Part I, 91% of patients taking background MTX in addition to tocilizumab and 83% of patients on tocilizumab monotherapy achieved an ACR 30 response at week 16 compared to baseline and entered the blinded withdrawal period (Part II) of the study. The proportions of patients with JIA ACR 50/70 responses in Part I were 84.0%, and 64%, respectively for patients taking background MTX in addition to tocilizumab and 80% and 55% respectively for patients on tocilizumab monotherapy.

In Part II, patients (ITT, n=163) were randomized to ACTEMRA (same dose received in Part I) or placebo in a 1:1 ratio that was stratified by concurrent methotrexate use and concurrent corticosteroid use. Each patient continued in Part II of the study until Week 40 or until the patient satisfied JIA ACR 30 flare criteria (relative to Week 16) and qualified for escape.

The primary endpoint was the proportion of patients with a JIA ACR 30 flare at week 40 relative to week 16. JIA ACR 30 flare was defined as 3 or more of the 6 core outcome variables worsening by at least 30% with no more than 1 of the remaining variables improving by more than 30% relative to Week 16.

ACTEMRA treated patients experienced significantly fewer disease flares compared to placebo-treated patients (26% [21/82] versus 48% [39/81]; adjusted difference in proportions -21%, 95% CI: -35%, -8%).

During the withdrawal phase (Part II), more patients treated with ACTEMRA showed JIA ACR 30/50/70 responses at Week 40 compared to patients withdrawn to placebo.

14.7 Polyarticular Juvenile Idiopathic Arthritis – Subcutaneous Administration

Subcutaneously administered ACTEMRA in pediatric patients with polyarticular juvenile idiopathic arthritis (PJIA) was assessed in WA28117 (NCT01904279), a 52-week, open-label, multicenter, PK-PD and safety study to determine the appropriate subcutaneous dose of ACTEMRA that achieved comparable PK/PD profiles to the ACTEMRA-IV regimen. PJIA patients aged 1 to 17 years with an inadequate response or inability to tolerate MTX, including patients with well-controlled disease on treatment with ACTEMRA-IV and ACTEMRA-naïve patients with active disease, were treated with subcutaneous ACTEMRA based on body weight.

Patients weighing at or above 30 kg (n = 25) were treated with 162 mg of ACTEMRA-SC every 2 weeks and patients weighing less than 30 kg (n = 27) received 162 mg of ACTEMRA-SC every 3 weeks for 52 weeks. Of these 52 patients, 37 (71%) were naive to ACTEMRA and 15 (29%) had been receiving ACTEMRA-IV and switched to ACTEMRA-SC at baseline.

The efficacy of subcutaneous ACTEMRA in children 2 to 17 years of age is based on pharmacokinetic exposure and extrapolation of the established efficacy of intravenous ACTEMRA in polyarticular JIA patients and subcutaneous ACTEMRA in patients with RA [see Clinical Pharmacology (12.3) and Clinical Studies (14.2 and 14.6)].

14.8 Systemic Juvenile Idiopathic Arthritis – Intravenous Administration

The efficacy of ACTEMRA for the treatment of active SJIA was assessed in WA18221 (NCT00642460), a 12-week randomized, double blind, placebo-controlled, parallel group, 2-arm study. Patients treated with or without MTX, were randomized (ACTEMRA:placebo = 2:1) to one of two treatment groups: 75 patients received ACTEMRA infusions every two weeks at either 8 mg per kg for patients at or above 30 kg or 12 mg per kg for patients less than 30 kg and 37 were randomized to receive placebo infusions every two weeks. Corticosteroid tapering could occur from week six for patients who achieved a JIA ACR 70 response. After 12 weeks or at the time of escape, due to disease worsening, patients were treated with ACTEMRA in the open-label extension phase at weight appropriate dosing.

The primary endpoint was the proportion of patients with at least 30% improvement in JIA ACR core set (JIA ACR 30 response) at Week 12 and absence of fever (no temperature at or above 37.5°C in the preceding 7 days). JIA ACR (American College of Rheumatology) responses are defined as the percentage improvement (e.g., 30%, 50%, 70%) in 3 of any 6 core outcome variables compared to baseline, with worsening in no more than 1 of the remaining variables by 30% or more. Core outcome variables consist of physician global assessment, parent per patient global assessment, number of joints with active arthritis, number of joints with limitation of movement, erythrocyte sedimentation rate (ESR), and functional ability (childhood health assessment questionnaire-CHAQ).

Primary endpoint result and JIA ACR response rates at Week 12 are shown in Table 11.

Table 11 Efficacy Findings at Week 12
 | ACTEMRA N=75 | Placebo N=37
Primary Endpoint: JIA ACR 30 response + absence of fever
Responders | 85% | 24%
Weighted difference (95% CI) | 62 (45, 78) | -
JIA ACR Response Rates at Week 12
JIA ACR 30
Responders | 91% | 24%
Weighted difference [The weighted difference is the difference between the ACTEMRA and Placebo response rates, adjusted for the stratification factors (weight, disease duration, background oral corticosteroid dose and background methotrexate use).] (95% CI) [CI: confidence interval of the weighted difference.] | 67 (51, 83) | -
JIA ACR 50
Responders | 85% | 11%
Weighted difference (95% CI) | 74 (58, 90) | -
JIA ACR 70
Responders | 71% | 8%
Weighted difference (95% CI) | 63 (46, 80) | -

The treatment effect of ACTEMRA was consistent across all components of the JIA ACR response core variables. JIA ACR scores and absence of fever responses in the open label extension were consistent with the controlled portion of the study (data available through 44 weeks).

Systemic Features

Of patients with fever or rash at baseline, those treated with ACTEMRA had fewer systemic features; 35 out of 41 (85%) became fever free (no temperature recording at or above 37.5°C in the preceding 14 days) compared to 5 out of 24 (21%) of placebo-treated patients, and 14 out of 22 (64%) became free of rash compared to 2 out of 18 (11%) of placebo-treated patients. Responses were consistent in the open label extension (data available through 44 weeks).

Corticosteroid Tapering

Of the patients receiving oral corticosteroids at baseline, 8 out of 31 (26%) placebo and 48 out of 70 (69%), ACTEMRA patients achieved a JIA ACR 70 response at week 6 or 8 enabling corticosteroid dose reduction. Seventeen (24%) ACTEMRA patients versus 1 (3%) placebo patient were able to reduce the dose of corticosteroid by at least 20% without experiencing a subsequent JIA ACR 30 flare or occurrence of systemic symptoms to week 12. In the open label portion of the study, by week 44, there were 44 out of 103 (43%) ACTEMRA patients off oral corticosteroids. Of these 44 patients 50% were off corticosteroids 18 weeks or more.

Health Related Outcomes

Physical function and disability were assessed using the Childhood Health Assessment Questionnaire Disability Index (CHAQ-DI). Seventy-seven percent (58 out of 75) of patients in the ACTEMRA treatment group achieved a minimal clinically important improvement in CHAQ-DI (change from baseline of ≥ 0.13 units) at week 12 compared to 19% (7 out of 37) in the placebo treatment group.

14.9 Systemic Juvenile Idiopathic Arthritis – Subcutaneous Administration

Subcutaneously administered ACTEMRA in pediatric patients with systemic juvenile idiopathic arthritis (SJIA) was assessed in WA28118 (NCT01904292), a 52-week, open-label, multicenter, PK-PD and safety study to determine the appropriate subcutaneous dose of ACTEMRA that achieved comparable PK/PD profiles to the ACTEMRA-IV regimen.

Eligible patients received ACTEMRA subcutaneously dosed according to body weight, with patients weighing at or above 30 kg (n = 26) dosed with 162 mg of ACTEMRA every week and patients weighing below 30 kg (n = 25) dosed with 162 mg of ACTEMRA every 10 days (n=8) or every 2 weeks (n=17) for 52 weeks. Of these 51 patients, 26 (51%) were naive to subcutaneous ACTEMRA and 25 (49%) had been receiving ACTEMRA intravenously and switched to subcutaneous ACTEMRA at baseline.

The efficacy of subcutaneous ACTEMRA in children 2 to 17 years of age is based on pharmacokinetic exposure and extrapolation of the established efficacy of intravenous ACTEMRA in systemic JIA patients [see Clinical Pharmacology (12.3) and Clinical Studies (14.8)].

14.10 Cytokine Release Syndrome – Intravenous Administration

The efficacy of ACTEMRA for the treatment of CRS was assessed in a retrospective analysis of pooled outcome data from clinical trials of CAR T-cell therapies for hematological malignancies. Evaluable patients had been treated with tocilizumab 8 mg/kg (12 mg/kg for patients < 30 kg) with or without additional high-dose corticosteroids for severe or life-threatening CRS; only the first episode of CRS was included in the analysis. The study population included 24 males and 21 females (total 45 patients) of median age 12 years (range, 3–23 years); 82% were Caucasian. The median time from start of CRS to first dose of tocilizumab was 4 days (range, 0-18 days). Resolution of CRS was defined as lack of fever and off vasopressors for at least 24 hours. Patients were considered responders if CRS resolved within 14 days of the first dose of tocilizumab, if no more than 2 doses of tocilizumab were needed, and if no drugs other than tocilizumab and corticosteroids were used for treatment. Thirty-one patients (69%; 95% CI: 53%–82%) achieved a response. Achievement of resolution of CRS within 14 days was confirmed in a second study using an independent cohort that included 15 patients (range: 9–75 years old) with CAR T cell-induced CRS.

14.11 COVID-19 – Intravenous Administration

The efficacy of ACTEMRA for the treatment of COVID-19 in adults was based on RECOVERY (NCT04381936), a randomized, controlled, open-label, platform study, and supported by the results from EMPACTA (NCT04372186), a randomized, double-blind, placebo-controlled study. Results of two other randomized, double-blind, placebo-controlled studies, COVACTA (NCT04320615) and REMDACTA (NCT04409262), which evaluated the efficacy of ACTEMRA for the treatment of COVID-19 are also summarized.

RECOVERY (Randomised Evaluation of COVID-19 Therapy) Collaborative Group Study in Hospitalized Adults Diagnosed with COVID-19

RECOVERY was a randomized, controlled, open-label, multicenter platform study conducted in the United Kingdom to evaluate the efficacy and safety of potential treatments in hospitalized adult patients with severe COVID-19 pneumonia. Eligible patients for the ACTEMRA portion of the study had clinically suspected or laboratory-confirmed SARS-CoV-2 infection and no medical contraindications to any of the treatments and had clinical evidence of progressive COVID-19 (defined as oxygen saturation <92% on room air or receiving oxygen therapy, and CRP ≥75 mg/L). Patients were then randomized to receive either standard of care (SoC) or intravenous ACTEMRA at a weight-tiered dosing comparable to the recommended dosage [see Clinical Pharmacology (12.3)] in addition to SoC.

Efficacy analyses were performed in the intent-to-treat (ITT) population comprising 4116 adult patients who were randomized to the ACTEMRA + SoC arm (n=2022) or to the SoC arm (n=2094). The mean age of participants was 64 years (range: 20 to 101), and patients were 67% male, 76% White, 11% Asian, 3% Black or African American, and 1% mixed race. At baseline, 0.2% of patients were not on supplemental oxygen, 45% of patients required low flow oxygen, 41% of patients required non-invasive ventilation or high-flow oxygen, and 14% of patients required invasive mechanical ventilation; 82% of patients were reported to be receiving systemic corticosteroids.

The primary efficacy endpoint was time to death through Day 28. The results for the overall population and the subgroups of patients who were or were not receiving systemic corticosteroids at time of randomization are summarized in Table 12.

Table 12 Mortality through Day 28 in RECOVERY
 | ACTEMRA+ SoC N=2022 n (%) [P-value reflects that the RECOVERY trial primary analysis results were statistically significant at the two-sided significance level of α = 0.05.] | SoC N=2094 n (%) | Hazard Ratio (95% CI) | Risk Difference (95% CI)
Mortality | 621 (30.7%) | 729 (34.9%) | 0.85 (0.76, 0.94) p= 0.0028 | -4.1% (-7.0, -1.3)
By baseline receipt of corticosteroid use
Mortality for patients receiving systemic corticosteroids at randomization [Probabilities of dying by Day 28 were estimated by the Kaplan-Meier method.] | 482/1664 (29.0%) | 600/1721 (34.9%) | 0.79 (0.70, 0.89) | -5.9% (-9.1, -2.8)
Mortality for patients not receiving systemic corticosteroids at randomization | 139/357 (39.0%) | 127/367 (34.6%) | 1.16 (0.91, 1.48) | 4.4% (-2.6, 11.5)

EMPACTA

EMPACTA was a randomized, double-blind, placebo-controlled, multicenter study to evaluate intravenous ACTEMRA 8 mg/kg in combination with SoC in hospitalized, non-ventilated adult patients with COVID-19 pneumonia. Eligible patients were at least 18 years of age, had confirmed SARS-CoV-2 infection by a positive reverse-transcriptase polymerase chain reaction (RT-PCR) result, had pneumonia confirmed by radiography, and had SpO2 < 94% on ambient air.

Of the 389 patients randomized, efficacy analyses were performed in the modified intent-to-treat (mITT) population comprising 377 patients who were randomized and received study medication (249 in the ACTEMRA arm; 128 in the placebo arm). The mean age of participants was 56 years (range: 20 to 95); 59% of patients were male, 56% were of Hispanic or Latino ethnicity, 53% were White, 20% were American Indian/Alaska Native, 15% were Black/African American and 2% were Asian. At baseline, 9% patients were not on supplemental oxygen, 64% patients required low flow oxygen, 27% patients required high-flow oxygen, and 73% were on corticosteroids.

The primary efficacy endpoint evaluated time to progression to mechanical ventilation or death through Day 28. The hazard ratio comparing ACTEMRA to placebo was 0.56 (95% CI, 0.33 to 0.97), a statistically significant result (log-rank, p-value = 0.036). The cumulative proportion of patients who required mechanical ventilation or died by Day 28 was 12.0% (95% CI, 8.5% to 16.9%) in the ACTEMRA arm and 19.3% (95% CI, 13.3% to 27.4%) in the placebo arm.

Mortality at Day 28 was 10.4% in the ACTEMRA arm versus 8.6% in the placebo arm (weighted difference (ACTEMRA arm - placebo arm): 2.0% [95% CI, -5.2% to 7.8%]).

COVACTA

COVACTA was a randomized, double-blind, placebo-controlled, multicenter study to evaluate intravenous ACTEMRA 8 mg/kg in combination with SoC for the treatment of adult patients hospitalized with severe COVID-19 pneumonia. The study randomized 452 patients who were at least 18 years of age with confirmed SARS-CoV-2 infection by a positive RT-PCR result, had pneumonia confirmed by radiography, and had oxygen saturation of 93% or lower on ambient air or a ratio of arterial oxygen partial pressure to fractional inspired oxygen of 300 mmHg or less. At baseline, 3% of patients were not on supplemental oxygen, 28% were on low flow oxygen, 30% were on non-invasive ventilation or high flow oxygen, 38% were on invasive mechanical ventilation, and 22% were on corticosteroids. The primary efficacy endpoint was clinical status on Day 28 assessed on a 7-category ordinal scale that ranged from "discharged" to "death." There were no statistically significant differences observed in the distributions of clinical status on the 7-category ordinal scale at Day 28 when comparing the ACTEMRA arm to the placebo arm.

Mortality at Day 28 was 19.7% in the ACTEMRA arm versus 19.4% in the placebo arm (weighted difference (ACTEMRA arm - placebo arm): 0.3% [95% CI, -7.6 to 8.2]).

REMDACTA

REMDACTA was a randomized, double-blind, placebo-controlled, multicenter study to evaluate intravenous ACTEMRA 8 mg/kg in combination with intravenous remdesivir (RDV) 200 mg on Day 1 followed by 100 mg once daily for a total of 10 days in hospitalized adult patients with severe COVID-19 pneumonia. The study randomized 649 adult patients with SARS-CoV-2 infection confirmed by a positive polymerase chain reaction (PCR) result, pneumonia confirmed by radiography, and who required supplemental oxygen > 6 L/min to maintain SpO2 >93%. At baseline, 7% of patients were on low flow oxygen, 80% were on non-invasive ventilation or high flow oxygen, 14% were on invasive mechanical ventilation, and 84% were on corticosteroids.

The primary efficacy endpoint was time from randomization to hospital discharge or 'ready for discharge' up to Day 28. There was no statistically significant difference between the treatment arms with respect to time to hospital discharge or "ready for discharge" through Day 28.

Mortality at Day 28 was 18.1% in the ACTEMRA+ RDV arm versus 19.5% in the placebo +RDV arm (weighted difference (ACTEMRA arm - placebo arm): -1.3% [95% CI, -7.8% to 5.2%]).

Mortality Across Studies in Patients Receiving Baseline Corticosteroids

A study-level meta-analysis was conducted on EMPACTA, COVACTA, REMDACTA and RECOVERY studies. For each of the four studies, the risk difference through Day 28 was estimated by the Kaplan-Meier method in the subgroup of patients receiving baseline corticosteroids, summarized in Figure 3. Patients from the RECOVERY trial represent 78.8% of the total sample size in this meta-analysis. The combined risk difference showed that ACTEMRA treatment (n=2261) resulted in a 4.61% absolute reduction in the risk of death at Day 28 (risk difference=-4.6%; 95% CI: -7.3% to -1.9%) compared to SoC (n=2034).

Figure 3 Risk Differences Through Day 28 for Baseline Corticosteroid Use Subpopulation in RECOVERY, EMPACTA, COVACTA and REMDACTA studies

16 HOW SUPPLIED/STORAGE AND HANDLING

For Intravenous Infusion

ACTEMRA (tocilizumab) injection is a preservative-free, sterile clear, colorless to pale yellow solution. ACTEMRA is supplied as 80 mg/4 mL (NDC 50242-135-01), 200 mg/10 mL (NDC 50242-136-01), and 400 mg/20 mL (NDC 50242-137-01) individually packaged 20 mg/mL single-dose vials for further dilution prior to intravenous infusion.

For Subcutaneous Injection

ACTEMRA (tocilizumab) injection is supplied as a preservative-free, sterile, clear, colorless to slightly yellowish solution for subcutaneous administration. The following packaging configurations are available:

- Each single-dose prefilled syringe delivers 162 mg/0.9 mL (NDC 50242-138-01).
- Each single-dose ACTPen® autoinjector delivers 162 mg/0.9 mL (NDC 50242-143-01).

Storage and Handling: Do not use beyond expiration date on the container, package, prefilled syringe, or autoinjector. ACTEMRA must be refrigerated at 36°F to 46°F (2ºC to 8ºC). Do not freeze. Protect the vials, syringes, and autoinjectors from light by storage in the original package until time of use, and keep syringes and autoinjectors dry. Once removed from the refrigerator, the prefilled syringe and autoinjector can be stored up to 2 weeks at or below 86°F (30°C). The prefilled syringe and autoinjector must always be kept in the carton.

17 PATIENT COUNSELING INFORMATION

Advise the patient to read the FDA-approved patient labeling (Medication Guide and Instructions for Use).

Serious Infections

Inform patients that ACTEMRA may lower their resistance to infections [see Warnings and Precautions (5.1)]. Instruct the patient of the importance of contacting their doctor immediately when symptoms suggesting infection appear in order to assure rapid evaluation and appropriate treatment.

Gastrointestinal Perforation

Inform patients that some patients who have been treated with ACTEMRA have had serious side effects in the stomach and intestines [see Warnings and Precautions (5.2)]. Instruct the patient of the importance of contacting their doctor immediately when symptoms of fever, severe, persistent abdominal pain, and change in bowel habits appear to assure rapid evaluation and appropriate treatment.

Hypersensitivity and Serious Allergic Reactions

Inform patients that some patients who have been treated with ACTEMRA have developed serious allergic reactions, including anaphylaxis, as well as serious skin reactions [see Warnings and Precautions (5.6)]. Advise patients to stop taking ACTEMRA and seek immediate medical attention if they experience any symptom of serious allergic reactions (including rash, hives, and swelling of the face, lips, tongue, and throat that may cause difficulty in breathing or swallowing).

Instruction on Injection Technique

Assess patient suitability for home use for subcutaneous injection. Perform the first injection under the supervision of a qualified healthcare professional. If a patient or caregiver is to administer subcutaneous ACTEMRA, instruct him/her in injection techniques and assess his/her ability to inject subcutaneously to ensure proper administration of subcutaneous ACTEMRA and the suitability for home use [see Instructions for Use].

Prior to use, remove the prefilled syringe (PFS) or autoinjector from the refrigerator and allow to sit at room temperature outside of the carton for 30 minutes (PFS) or 45 minutes (autoinjector), out of the reach of children. Do not warm ACTEMRA in any other way.

Advise patients to consult their healthcare provider if the full dose is not received.

A puncture-resistant container for disposal of needles, syringes and autoinjectors should be used and should be kept out of the reach of children. Instruct patients or caregivers in the technique as well as proper needle, syringe and autoinjector disposal, and caution against reuse of these items.

Pregnancy

Inform female patients of reproductive potential that ACTEMRA may cause fetal harm and to inform their prescriber of a known or suspected pregnancy [see Use in Specific Populations (8.1)].

ACTEMRA® (tocilizumab)
Manufactured by:
Genentech, Inc.
A Member of the Roche Group
1 DNA Way
South San Francisco, CA 94080-4990

ACTEMRA is a registered trademark of Chugai Seiyaku Kabushiki
Kaisha Corp., a member of the Roche Group
© 2025 Genentech, Inc.

U.S. License No.: 1048

Medication Guide
ACTEMRA® (AC-TEM-RA)
(tocilizumab) injection
for intravenous use
ACTEMRA® (AC-TEM-RA)
(tocilizumab) injection
for subcutaneous use

What is the most important information I should know about ACTEMRA?

ACTEMRA can cause serious side effects including:

1. Serious Infections. ACTEMRA is a medicine that affects your immune system. ACTEMRA can lower the ability of your immune system to fight infections. Some people have serious infections while taking ACTEMRA, including tuberculosis (TB), and infections caused by bacteria, fungi, or viruses that can spread throughout the body. Some people have died from these infections. Your healthcare provider should assess you for TB before starting ACTEMRA (except if you have COVID-19).

If you have COVID-19, your healthcare provider should monitor you for signs and symptoms of new infections during and after treatment with ACTEMRA.

Your healthcare provider should monitor you closely for signs and symptoms of TB during and after treatment with ACTEMRA.

- You should not start taking ACTEMRA if you have any kind of infection unless your healthcare provider says it is okay.

Before starting ACTEMRA, tell your healthcare provider if you:

- think you have an infection or have symptoms of an infection, with or without a fever, such as:

- sweating or chills
- shortness of breath
- warm, red, or painful skin or sores on your body

- feel very tired
- muscle aches
- blood in phlegm
- diarrhea or stomach pain

- cough
- weight loss
- burning when you urinate or urinating more often than normal

- are being treated for an infection.
- get a lot of infections or have infections that keep coming back.
- have diabetes, HIV, or a weak immune system. People with these conditions have a higher chance for infections.
- have TB, or have been in close contact with someone with TB.
- live or have lived, or have traveled to certain parts of the country (such as the Ohio and Mississippi River valleys and the Southwest) where there is an increased chance for getting certain kinds of fungal infections (histoplasmosis, coccidiomycosis, or blastomycosis). These infections may happen or become more severe if you use ACTEMRA. Ask your healthcare provider, if you do not know if you have lived in an area where these infections are common.
- have or have had hepatitis B.

After starting ACTEMRA, call your healthcare provider right away if you have any symptoms of an infection. ACTEMRA can make you more likely to get infections or make worse any infection that you have.

2. Tears (perforation) of the stomach or intestines.
  - Tell your healthcare provider if you have had diverticulitis (inflammation in parts of the large intestine) or ulcers in your stomach or intestines. Some people taking ACTEMRA get tears in their stomach or intestine. This happens most often in people who also take nonsteroidal anti-inflammatory drugs (NSAIDs), corticosteroids, or methotrexate.
  - Tell your healthcare provider right away if you have fever and new onset stomach-area pain that does not go away, and a change in your bowel habits.
3. Liver problems (Hepatotoxicity): Some people have experienced serious life-threatening liver problems, which required a liver transplant or led to death. Your healthcare provider may tell you to stop taking ACTEMRA if you develop new or worse liver problems during treatment with ACTEMRA. Tell your healthcare provider right away if you have any of the following symptoms:

- feeling tired (fatigue)
- lack of appetite for several days or longer (anorexia)
- yellowing of your skin or the whites of your eyes (jaundice)
- abdominal swelling and pain on the right side of your stomach-area
- light colored stools

- weakness
- nausea and vomiting
- confusion
- dark "tea-colored" urine

4. Changes in certain laboratory test results. Your healthcare provider should do blood tests before you start receiving ACTEMRA. If you have rheumatoid arthritis (RA), giant cell arteritis (GCA), or systemic sclerosis-interstitial lung disease (SSc-ILD) your healthcare provider should do blood tests every 4 to 8 weeks after you start receiving ACTEMRA for the first 6 months and then every 3 months after that. If you have polyarticular juvenile idiopathic arthritis (PJIA) you will have blood tests done every 4 to 8 weeks during treatment. If you have systemic juvenile idiopathic arthritis (SJIA) you will have blood tests done every 2 to 4 weeks during treatment. These blood tests are to check for the following side effects of ACTEMRA:
  - low neutrophil count. Neutrophils are white blood cells that help the body fight off bacterial infections.
  - low platelet count. Platelets are blood cells that help with blood clotting and stop bleeding.
  - increase in certain liver function tests.
  - increase in blood cholesterol levels. You may also have changes in other laboratory tests, such as your blood cholesterol levels. Your healthcare provider should do blood tests to check your cholesterol levels 4 to 8 weeks after you start receiving ACTEMRA.
  Your healthcare provider will determine how often you will have follow-up blood tests. Make sure you get all your follow-up blood tests done as ordered by your healthcare provider.
  You should not receive ACTEMRA if your neutrophil or platelet counts are too low or your liver function tests are too high.
  Your healthcare provider may stop your ACTEMRA treatment for a period of time or change your dose of medicine if needed because of changes in these blood test results.

5. Cancer. ACTEMRA may increase your risk of certain cancers by changing the way your immune system works. Tell your healthcare provider if you have ever had any type of cancer.

See "What are the possible side effects with ACTEMRA?" for more information about side effects.

What is ACTEMRA?

ACTEMRA is a prescription medicine called an Interleukin-6 (IL-6) receptor antagonist. ACTEMRA is used:

- To treat adults with moderately to severely active rheumatoid arthritis (RA), after at least one other medicine called a Disease-Modifying Anti-Rheumatic Drug (DMARD) has been used and did not work well.
- To treat adults with giant cell arteritis (GCA).
- For slowing the rate of decline in lung function in adults with systemic sclerosis-associated interstitial lung disease (SSc-ILD) (also known as scleroderma associated ILD).
- To treat people with active PJIA ages 2 and above.
- To treat people with active SJIA ages 2 and above.
- To treat people age 2 years and above who experience severe or life-threatening Cytokine Release Syndrome (CRS) following chimeric antigen receptor (CAR) T cell treatment.
- To treat hospitalized people ages 2 years and above with coronavirus disease 2019 (COVID-19) receiving systemic corticosteroids and requiring supplemental oxygen or mechanical ventilation.
- ACTEMRA is not approved for subcutaneous use in people with CRS or COVID-19.

It is not known if ACTEMRA is safe and effective in children with PJIA, SJIA, CRS or COVID-19 under 2 years of age or in children with conditions other than PJIA, SJIA, CRS or COVID-19.

Do not take ACTEMRA: if you are allergic to tocilizumab, or any of the ingredients in ACTEMRA. See the end of this Medication Guide for a complete list of ingredients in ACTEMRA.

Before you receive ACTEMRA, tell your healthcare provider about all of your medical conditions, including if you:

- have an infection. See "What is the most important information I should know about ACTEMRA?"
- have liver problems.
- have any stomach-area (abdominal) pain or been diagnosed with diverticulitis or ulcers in your stomach or intestines.
- have had a reaction to tocilizumab or any of the ingredients in ACTEMRA before.
- have or had a condition that affects your nervous system, such as multiple sclerosis.
- have recently received or are scheduled to receive a vaccine:
  - All vaccines should be brought up-to-date before starting ACTEMRA, unless urgent treatment initiation is required.
  - People who take ACTEMRA should not receive live vaccines.
  - People taking ACTEMRA can receive non-live vaccines.
- plan to have surgery or a medical procedure.
- are pregnant or plan to become pregnant. ACTEMRA may harm your unborn baby. Tell your healthcare provider if you become pregnant or think you may be pregnant during treatment with ACTEMRA.
- are breastfeeding or plan to breastfeed. It is not known if ACTEMRA passes into your breast milk. Talk to your healthcare provider about the best way to feed your baby if you take ACTEMRA.

Tell your healthcare provider about all of the medicines you take, including prescription, over-the-counter medicines, vitamins and herbal supplements. ACTEMRA and other medicines may affect each other causing side effects.

Especially tell your healthcare provider if you take:

- any other medicines to treat your RA. Taking ACTEMRA with these medicines may increase your risk of infection.
- medicines that affect the way certain liver enzymes work. Ask your healthcare provider if you are not sure if your medicine is one of these.

Know the medicines you take. Keep a list of them to show to your healthcare provider and pharmacist when you get a new medicine.

How will I receive ACTEMRA?

Into a vein (IV or intravenous infusion) for Rheumatoid Arthritis, Giant Cell Arteritis, PJIA, SJIA, CRS or COVID-19:

- If your healthcare provider prescribes ACTEMRA as an IV infusion, you will receive ACTEMRA from a healthcare provider through a needle placed in a vein in your arm. The infusion will take about 1 hour to give you the full dose of medicine.
- For rheumatoid arthritis, giant cell arteritis or PJIA you will receive a dose of ACTEMRA about every 4 weeks.
- For SJIA you will receive a dose of ACTEMRA about every 2 weeks.
- For CRS you will receive a single dose of ACTEMRA, and if needed, additional doses.
- For COVID-19, you will receive a single dose of ACTEMRA, and if needed one additional dose.
- While taking ACTEMRA, you may continue to use other medicines that help treat your rheumatoid arthritis, PJIA, SJIA or COVID-19 such as methotrexate, non-steroidal anti-inflammatory drugs (NSAIDs) and prescription steroids, as instructed by your healthcare provider.
- Keep all of your follow-up appointments and get your blood tests as ordered by your healthcare provider.

Under the skin (SC or subcutaneous injection) for Rheumatoid Arthritis, Giant Cell Arteritis, SSc-ILD, PJIA or SJIA:

- See the Instructions for Use at the end of this Medication Guide for instructions about the right way to prepare and give your ACTEMRA injections at home.
- ACTEMRA is available as a single-dose Prefilled Syringe or single-dose prefilled ACTPen® autoinjector.
- You may also receive ACTEMRA as an injection under your skin (subcutaneous). If your healthcare provider decides that you or a caregiver can give your injections of ACTEMRA at home, you or your caregiver should receive training on the right way to prepare and inject ACTEMRA. Do not try to inject ACTEMRA until you have been shown the right way to give the injections by your healthcare provider.
- For PJIA or SJIA, you may self-inject with the Prefilled Syringe or prefilled ACTPen® autoinjector, or your caregiver can give you ACTEMRA, if both your healthcare provider and parent/legal guardian find it appropriate.
- Your healthcare provider will tell you how much ACTEMRA to use and when to use it.

What are the possible side effects with ACTEMRA?

ACTEMRA can cause serious side effects, including:

- See "What is the most important information I should know about ACTEMRA?"
- Hepatitis B infection in people who carry the virus in their blood. If you are a carrier of the hepatitis B virus (a virus that affects the liver), the virus may become active while you use ACTEMRA. Your healthcare provider may do blood tests before you start treatment with ACTEMRA and while you are using ACTEMRA. Tell your healthcare provider if you have any of the following symptoms of a possible hepatitis B infection:

- feel very tired
- vomiting
- chills
- dark urine

- skin or eyes look yellow
- clay-colored bowel movements
- stomach discomfort
- skin rash

- little or no appetite
- fevers
- muscle aches

- Serious Allergic Reactions. Serious allergic reactions, including death, can happen with ACTEMRA. These reactions can happen with any infusion or injection of ACTEMRA, even if they did not occur with an earlier infusion or injection. Stop taking ACTEMRA, contact your healthcare provider, and get emergency help right away if you have any of the following signs of a serious allergic reaction:
  - swelling of your face, lips, mouth, or tongue
  - trouble breathing
  - wheezing
  - severe itching
  - skin rash, hives, redness, or swelling outside of the injection site area
  - dizziness or fainting
  - fast heartbeat or pounding in your chest (tachycardia)
  - sweating
- Nervous system problems. While rare, Multiple Sclerosis has been diagnosed in people who take ACTEMRA. It is not known what effect ACTEMRA may have on some nervous system disorders.

The most common side effects of ACTEMRA include:

- upper respiratory tract infections (common cold, sinus infections)
- headache
- increased blood pressure (hypertension)
- injection site reactions

Tell your healthcare provider about any side effect that bothers you or does not go away. These are not all the possible side effects of ACTEMRA. For more information, ask your healthcare provider or pharmacist.
Call your doctor for medical advice about side effects. You may report side effects to FDA at 1-800-FDA-1088.

You may also report side effects to Genentech at 1-888-835-2555.

General information about the safe and effective use of ACTEMRA.

Medicines are sometimes prescribed for purposes other than those listed in a Medication Guide. Do not give ACTEMRA to other people, even if they have the same symptoms that you have. It may harm them. You can ask your pharmacist or healthcare provider for information about ACTEMRA that is written for health professionals.

What are the ingredients in ACTEMRA?

Active ingredient: tocilizumab.

Inactive ingredients of Intravenous ACTEMRA: disodium phosphate dodecahydrate/sodium dihydrogen phosphate dihydrate buffered solution, polysorbate 80, sucrose, and water for Injection.

Inactive ingredients of Subcutaneous ACTEMRA: L-arginine hydrochloride, L-histidine, L-histidine hydrochloride monohydrate, L-methionine, polysorbate 80, and water for Injection.

ACTEMRA is a registered trademark of Chugai Seiyaku Kabushiki Kaisha Corp., a member of the Roche Group.

ACTPen is a registered trademark of Chugai Seiyaku Kabushiki Kaisha Corp., a member of the Roche Group.

Genentech, Inc.,
A Member of the Roche Group, 1 DNA Way, South San Francisco, CA 94080-4990 U.S. License No.: 1048
© 2025 Genentech, Inc. All rights reserved.
For more information, go to www.ACTEMRA.com or call 1-800-ACTEMRA.

Medication Guide has been approved by the U.S. Food and Drug Administration

Revised: 08/2025

Instructions for Use
ACTEMRA® (AC-TEM-RA)
(tocilizumab)
Injection, For Subcutaneous Use
Single-dose Prefilled Syringe

Read and follow the Instructions for Use that come with your ACTEMRA prefilled syringe before you start using it and each time you get a prescription refill. Before you use ACTEMRA prefilled syringe for the first time, make sure your healthcare provider shows you the right way to use it.

- Do not remove the needle cap until you are ready to inject ACTEMRA.
- Do not try to take apart the syringe at any time.
- Do not reuse the same syringe.

Parts of your ACTEMRA Prefilled Syringe (See Figure A).

Figure A

Supplies needed for your ACTEMRA Prefilled Syringe Injection (See Figure B):

- ACTEMRA prefilled syringe
- alcohol pad
- sterile cotton ball or gauze
- puncture-resistant container or sharps container for safe disposal of needle cap and used syringe (See Step 4 "Dispose of the syringe")
  Figure B

Step 1. Preparing for an ACTEMRA Injection

Find a comfortable space with a clean, flat, working surface.

- Take the box containing the syringe out of the refrigerator and open the box. Do not touch the trigger fingers on the syringe as this may damage the syringe.
- Remove 1 single-use ACTEMRA prefilled syringe from the box and let it warm up for 30 minutes to allow it to reach room temperature. If the syringe does not reach room temperature, this could cause your injection to feel uncomfortable and make it difficult to push the plunger in.
- Do not speed up the warming process in any way, such as using the microwave or placing the syringe in warm water.
- Check the expiration date on the ACTEMRA prefilled syringe (See Figure A). Do not use it if the expiration date has passed because it may not be safe to use. If the expiration date has passed safely dispose of the syringe in a sharps container and get a new one.

Do not remove the needle cap while allowing your ACTEMRA prefilled syringe to reach room temperature.

- Keep your unused syringes in the original carton and keep in the refrigerator at 36°F to 46°F (2°C to 8°C). Do not freeze.
- Once removed from the refrigerator, your prefilled syringe can be stored up to 2 weeks at or below 86°F (30°C). Your prefilled syringe must always be kept in the original carton in order to protect from light and moisture. Hold your ACTEMRA prefilled syringe with the covered needle pointing down (See Figure C).
  Figure C
- Check the liquid in the ACTEMRA prefilled syringe. It should be clear and colorless to pale yellow. Do not inject ACTEMRA if the liquid is cloudy, discolored, or has lumps or particles in it because it may not be safe to use. Safely dispose of the syringe in a sharps container and get a new one.
- Wash your hands well with soap and water.

Step 2. Choose and Prepare an Injection Site

Choose an Injection Site

- The front of your thigh and your abdomen except for the 2-inch area around your navel are the recommended injection sites (See Figure D).
- The outer area of the upper arms may also be used only if the injection is being given by a caregiver. Do not attempt to use the upper arm area by yourself (See Figure D).

Rotate Injection Site

- Choose a different injection site for each new injection at least 1-inch from the last area you injected.
- Do not inject into moles, scars, bruises, or areas where the skin is tender, red, hard or not intact.
  Figure D

Prepare the Injection Site

- Wipe the injection site with an alcohol pad in a circular motion and let it air dry to reduce the chance of getting an infection. Do not touch the injection site again before giving the injection.
- Do not fan or blow on the clean area.

Step 3. Inject ACTEMRA

- Hold the ACTEMRA prefilled syringe with 1 hand and pull the needle cap straight off with your other hand (See Figure E). Do not hold the plunger while you remove the needle cap. If you cannot remove the needle cap you should ask a caregiver for help or contact your healthcare provider.
  Figure E
- Throw away the needle cap in a sharps container.
- There may be a small air bubble in the ACTEMRA prefilled syringe. You do not need to remove it.
- You may see a drop of liquid at the end of the needle. This is normal and will not affect your dose.
- Do not touch the needle or let it touch any surfaces.
- Do not use the prefilled syringe if it is dropped.
- If it is not used within 5 minutes of needle cap removal, the syringe should be disposed of in the puncture resistant container or sharps container and a new syringe should be used.
- Never reattach the needle cap after removal.
- Hold the ACTEMRA prefilled syringe in 1 hand between the thumb and index finger (See Figure F).
  Figure F
- Do not pull back on the plunger of the syringe.
- Use your other hand and gently pinch the area of skin you cleaned. Hold the pinched skin firmly. Pinching the skin is important to make sure that you inject under the skin (into fatty tissue) but not any deeper (into muscle). Injection into muscle could cause the injection to feel uncomfortable.
- Do not hold or push on the plunger while inserting the needle into the skin.
- Use a quick, dart-like motion to insert the needle all the way into the pinched skin at an angle between 45° to 90° (See Figure G). It is important to use the correct angle to make sure the medicine is delivered under the skin (into fatty tissue), or the injection could be painful and the medicine may not work.
  Figure G
- Keep the syringe in position and let go of the pinch of skin.
- Slowly inject all of the medicine by gently pushing the plunger all the way down (See Figure H). You must press the plunger all the way down to get the full dose of medicine and to ensure the trigger fingers are completely pushed to the side. If the plunger is not fully depressed the needle shield will not extend to cover the needle when it is removed. If the needle is not covered, carefully place the syringe into the puncture resistant container to avoid injury with the needle.
  Figure H
- After the plunger is pushed all the way down, keep pressing down on the plunger to be sure all of the medicine is injected before taking the needle out of the skin.
- Keep pressing down on the plunger while you take the needle out of the skin at the same angle as inserted (See Figure I).
  Figure I
- After the needle is removed completely from the skin, release the plunger, allowing the needle-shield to protect the needle (See Figure J).
  Figure J

After the Injection

- There may be a little bleeding at the injection site. You can press a cotton ball or gauze over the injection site.
- Do not rub the injection site.
- If needed, you may cover the injection site with a small bandage.

Step 4. Dispose of the syringe

- The ACTEMRA prefilled syringe should not be reused.
- Put the used syringe into your puncture resistant container (See "How do I throw away used syringes?")
- Do not put the needle cap back on the needle.
- If your injection is given by another person, this person must also be careful when removing the syringe and disposing of the syringe to prevent accidental needle stick injury and passing infection.

How do I throw away used syringes?

- Put your used needles and syringes including ACTEMRA in a FDA-cleared sharps disposal container right away after use (See Figure K). Do not throw away (dispose of) loose needles and syringes in your household trash.
  Figure K
- If you do not have a FDA-cleared sharps disposal container, you may use a household container that is:
  - made of a heavy-duty plastic
  - can be closed with a tight-fitting, puncture-resistant lid, without sharps being able to come out
  - upright stable during use
  - leak-resistant
  - properly labeled to warn of hazardous waste inside the container
    - When your sharps disposal container is almost full, you will need to follow your community guidelines for the right way to dispose of your sharps disposal container. There may be state or local laws about how you should throw away used needles and syringes. For more information about the safe sharps disposal, and for specific information about sharps disposal in the state that you live in, go to the FDA's website at: http://www.fda.gov/safesharpsdisposal.
    - Do not dispose of your used sharps disposal container in your household trash unless your community guidelines permit this. Do not recycle your used sharps disposal container.
- Keep ACTEMRA prefilled syringes and the disposal container out of the reach of children.

Record your Injection

- Write the date, time, and specific part of your body where you injected yourself. It may also be helpful to write any questions or concerns about the injection so you can ask your healthcare provider.

If you have questions or concerns about your ACTEMRA prefilled syringe, please contact your healthcare provider familiar with ACTEMRA or call 1-800-ACTEMRA.

This Medication Guide and Instructions for Use has been approved by the U.S. Food and Drug Administration.
Medication Guide Revised: 08/2025
ACTEMRA is a registered trademark of Chugai Seiyaku Kabushiki Kaisha Corp., a member of the Roche Group.

Genentech, Inc.
A Member of the Roche Group
1 DNA Way
South San Francisco, CA 94080-4990

U.S. License No.: 1048
© 2025 Genentech, Inc. All rights reserved.

Instructions for Use
ACTEMRA® (AC-TEM-RA)
(tocilizumab)
Injection, For Subcutaneous Use
Single-dose Prefilled ACTPen® (AKT-PEN) Autoinjector

Read and follow the Instructions for Use that come with your ACTEMRA ACTPen autoinjector before you start using it and each time you get a prescription refill. Before you use the ACTEMRA ACTPen autoinjector for the first time, make sure your healthcare provider shows you the right way to use it.

Important: Keep your unused Autoinjectors in the original carton and keep in the refrigerator at 36°F to 46°F (2°C to 8°C). Do not freeze. Once removed from the refrigerator, your Autoinjector can be stored up to 2 weeks at or below 86°F (30°C). Your Autoinjector must always be kept in the original carton in order to protect from light and moisture.

- Do not remove the Autoinjector cap until you are ready to inject ACTEMRA.
- Do not try to take apart the Autoinjector at any time.
- Do not reuse the same Autoinjector.
- Do not use the Autoinjector through clothing.
- Do not leave the Autoinjector unattended.
- Do not use the Autoinjector if it appears to be damaged or if you have accidentally dropped the Autoinjector.
- Keep out of the reach of children.

Parts of your ACTEMRA ACTPen autoinjector (See Figure A).

Supplies needed for an injection using your ACTEMRA ACTPen autoinjector (See Figure B):

- 1 ACTEMRA ACTPen autoinjector
- 1 Alcohol pad
- 1 Sterile cotton ball or gauze
- 1 Puncture-resistant container or sharps container for safe disposal of Autoinjector cap and used Autoinjector (See Step 4 "Dispose of the Autoinjector")

Step 1. Preparing for an ACTEMRA Injection

Find a comfortable space with a clean, flat, working surface.

- Take the box containing the Autoinjector out of the refrigerator.
- If you are opening the box for the first time, check to make sure that it is properly sealed. Do not use the Autoinjector if the box looks like it has already been opened.
- Check that the Autoinjector box is not damaged. Do not use ACTEMRA ACTPen autoinjector if the box looks damaged.
- Check the expiration date on the Autoinjector box. Do not use the Autoinjector if the expiration date has passed because it may not be safe to use.
- Open the box, and remove 1 single-use ACTEMRA ACTPen autoinjector from the box.
- Return any remaining autoinjectors in the box to the refrigerator.
- Check the expiration date on the ACTEMRA ACTPen autoinjector (See Figure A). Do not use it if the expiration date has passed because it may not be safe to use. If the expiration date has passed, safely dispose of the Autoinjector in a sharps container and get a new one.
- Check the Autoinjector to make sure it is not damaged. Do not use the Autoinjector if it appears to be damaged or if you have accidentally dropped the Autoinjector.
- Place the Autoinjector on a clean, flat surface and let the Autoinjector warm up for 45 minutes to allow it to reach room temperature. If the Autoinjector does not reach room temperature, this could cause your injection to feel uncomfortable and it could take longer to inject.
  - Do not speed up the warming process in any way, such as using the microwave or placing the Autoinjector in warm water.
  - Do not leave the Autoinjector to warm up in direct sunlight.
  - Do not remove the green cap while allowing your ACTEMRA ACTPen autoinjector to reach room temperature.
- Hold your ACTEMRA ACTPen autoinjector with the green cap pointing down (See Figure C).
- Look in the clear Window area. Check the liquid in the ACTEMRA ACTPen autoinjector (See Figure C). It should be clear and colorless to pale yellow. Do not inject ACTEMRA if the liquid is cloudy, discolored, or has lumps or particles in it because it may not be safe to use. Safely dispose of the Autoinjector in a sharps container and get a new one.
- Wash your hands well with soap and water.

Step 2. Choose and Prepare an Injection Site

Choose an Injection Site

- The front of your thigh or your abdomen except for the 2-inch (5cm) area around your navel are the recommended injection sites (See Figure D).
- The outer area of the upper arms may also be used only if the injection is being given by a caregiver. Do not attempt to use the upper arm area by yourself (See Figure D).

Rotate Injection Site

- Choose a different injection site for each new injection at least 1 inch (2.5cm) from the last area you injected.
- Do not inject into moles, scars, bruises, or areas where the skin is tender, red, hard or not intact.

Prepare the Injection Site

- Wipe the injection site with an alcohol pad in a circular motion and let it air dry to reduce the chance of getting an infection. Do not touch the injection site again before giving the injection.
- Do not fan or blow on the clean area.

Step 3. Inject ACTEMRA

- Hold the ACTEMRA ACTPen autoinjector firmly with one hand. Twist and pull off the green cap with the other hand (See Figure E). The green cap contains a loose fitting metal tube.
- If you cannot remove the green cap you should ask a caregiver for help or contact your healthcare provider.
  Important: Do not touch the needle shield which is located at the tip of the Autoinjector below the Window area (See Figure A), to avoid accidental needle stick injury.
- Throw away the green cap in a sharps container.
- After you remove the green cap, the Autoinjector is ready for use. If the Autoinjector is not used within 3 minutes of the cap removal, the Autoinjector should be disposed of in the sharps container and a new Autoinjector should be used.
- Never reattach the green cap after removal.
- Hold the Autoinjector comfortably in 1 hand by the upper part, so that you can see the Window area of the Autoinjector (See Figure F).
- Use your other hand to gently pinch the area of skin you cleaned, to prepare a firm injection site (See Figure G). The Autoinjector requires a firm injection site to properly activate. Pinching the skin is important to make sure that you inject under the skin (into fatty tissue) but not any deeper (into muscle). Injection into muscle could cause the injection to feel uncomfortable.
- Do not press the green Activation button yet.
  Place the needle-shield of the Autoinjector against your pinched skin at a 90° angle (See Figure H).
- It is important to use the correct angle to make sure the medicine is delivered under the skin (into fatty tissue), or the injection could be painful and the medicine may not work.
- Continue to gently pinch throughout the injection procedure.
- To use the Autoinjector, you first have to unlock the green Activation button. To unlock it, press the Autoinjector firmly against your pinched skin until the needle-shield is completely pushed in (See Figure I).
- Continue to keep the needle-shield pushed in. If you do not keep the needle-shield completely pushed against the skin, the green Activation button will not work. Continue to pinch the skin while you keep the Autoinjector in place.
- Press the green Activation button to start the injection. A "click" sound indicates the start of the injection. Keep the green button pressed in and continue holding the Autoinjector pressed firmly against your skin (See Figure J). If you cannot start the injection you should ask for help from a caregiver or contact your healthcare provider.
- The purple indicator will move along the Window area during the injection (See Figure K).
- Watch the purple indicator until it stops moving to be sure the full dose of medicine is injected. This may take up to 10 seconds.
- You may hear a second "click" during the injection but you should continue to hold the Autoinjector firmly against your skin until the purple indicator stops moving.
- When the purple indicator has stopped moving, release the green button. Lift the Autoinjector straight off of the injection site at a 90° angle to remove the needle from the skin. The needle-shield will then move out and lock into place covering the needle (See Figure L).
- Check the Window area to see that it is filled with the purple indicator (See Figure L).
- If the Window area is not filled by the purple indicator then:
  - The needle-shield may not have locked. Do not touch the needle-shield of the Autoinjector, because you may stick yourself with the needle. If the needle is not covered, carefully place the Autoinjector into the sharps container to avoid any injury with the needle.
  - You may not have received your full dose of ACTEMRA. Do not try to re-use the Autoinjector. Do not repeat the injection with another Autoinjector. Call your healthcare provider for help.

After the Injection

- There may be a little bleeding at the injection site. You can press a cotton ball or gauze over the injection site.
- Do not rub the injection site.
- If needed, you may cover the injection site with a small bandage.

Step 4. Dispose of the Autoinjector

- The ACTEMRA ACTPen autoinjector should not be reused.
- Put the used Autoinjector into your sharps container (See "How do I dispose of used Autoinjectors?").
- Do not put the cap back on the Autoinjector.
- If your injection is given by another person, this person must also be careful when removing the Autoinjector and disposing of it to prevent accidental needle stick injury and passing infection.

How do I dispose of used Autoinjectors?

- Put your used ACTEMRA ACTPen autoinjector and green cap in a FDA-cleared sharps disposal container right away after use (See Figure M).
- Do not throw away (dispose of) the Autoinjector and the green cap in your household trash.
- If you do not have a FDA-cleared sharps disposal container, you may use a household container that is:
  - made of a heavy-duty plastic
  - can be closed with a tight-fitting, puncture-resistant lid, without sharps being able to come out
  - upright stable during use
  - leak-resistant
  - properly labeled to warn of hazardous waste inside the container
    - When your sharps disposal container is almost full, you will need to follow your community guidelines for the right way to dispose of your sharps disposal container. There may be state or local laws about how you should dispose of used Autoinjectors. For more information about the safe sharps disposal, and for specific information about sharps disposal in the state that you live in, go to the FDA's website at: http://www.fda.gov/safesharpsdisposal.
    - Do not dispose of your used sharps disposal container in your household trash unless your community guidelines permit this. Do not recycle your used sharps disposal container.

Keep the ACTEMRA ACTPen autoinjector and disposal container out of the reach of children.

Record your Injection

- Write the date, time, and specific part of your body where you injected yourself. It may also be helpful to write any questions or concerns about the injection so you can ask your healthcare provider.

If you have any questions or concerns about your ACTEMRA ACTPen autoinjector, talk to your healthcare provider familiar with ACTEMRA or call 1-800-ACTEMRA.

This Medication Guide and Instructions for Use has been approved by the U.S. Food and Drug Administration.
Medication Guide Revised: 08/2025
ACTEMRA is a registered trademark of Chugai Seiyaku Kabushiki Kaisha Corp., a member of the Roche Group.
ACTPen is a registered trademark of Chugai Seiyaku Kabushiki Kaisha Corp., a member of the Roche Group.

Genentech, Inc.
A Member of the Roche Group
1 DNA Way
South San Francisco, CA 94080-4990

U.S. License No.: 1048

© 2025 Genentech, Inc. All rights reserved.

Representative sample of labeling (see the HOW SUPPLIED section for complete listing):

PRINCIPAL DISPLAY PANEL - 80 mg/4 mL Vial Carton

NDC 50242-135-01

Actemra®
(tocilizumab)
Injection

80 mg/4 mL

(20 mg/mL)
For Intravenous Infusion only after
dilution.
Single-Dose Vial; Discard unused portion
ATTENTION PROVIDER: Each patient is
required to receive the enclosed
Medication Guide
No Preservative

Rx only

Genentech

11037819

PRINCIPAL DISPLAY PANEL - 200 mg/10 mL Vial Carton

NDC 50242-136-01

Actemra®
(tocilizumab)
Injection

200 mg/10 mL

(20 mg/mL)
For Intravenous Infusion only after
dilution.
Single-Dose Vial; Discard unused portion
ATTENTION PROVIDER: Each patient is
required to receive the enclosed
Medication Guide
No Preservative

Rx only

Genentech

11037833

PRINCIPAL DISPLAY PANEL - 400 mg/20 mL Vial Carton

NDC 50242-137-01

Actemra®
(tocilizumab)
Injection

400 mg/20 mL

(20 mg/mL)
For Intravenous Infusion only after
dilution.
Single-Dose Vial; Discard unused portion
ATTENTION PROVIDER: Each patient is
required to receive the enclosed
Medication Guide
No Preservative

Rx only

Genentech

11037818

PRINCIPAL DISPLAY PANEL - 162 mg/0.9 mL Prefilled Syringe Carton

NDC 50242-138-01

Rx only

Actemra®
(tocilizumab)
Injection

162 mg/0.9 mL

For Subcutaneous
Injection Only

Single Dose Prefilled
Syringe - Discard Unused
Portion

Sterile

ATTENTION
PHARMACIST:
Each patient is required
to receive the enclosed
Medication Guide.

Refrigerate Immediately

Each Prefilled Syringe
Contains:
162 mg/0.9 mL

Genentech

↓ TO OPEN ↓

10249853

PRINCIPAL DISPLAY PANEL - 162 mg/0.9 mL Autoinjector Carton

NDC 50242-143-01

Rx only

Actemra®
ACTPen®
(tocilizumab)
Injection

162 mg/0.9 mL

For Subcutaneous
Injection Only
Sterile

ATTENTION
PHARMACIST:
Each patient is required
to receive the enclosed
Medication Guide.

Refrigerate Immediately

CAUTION

Injection is
complete only
when
the purple
indicator stops
moving.
This may take up
to 10 seconds.
Refer to
instructions for
use.

1 Single-dose
Autoinjector
Discard Unused or
Expired Portion

Genentech

↓ TO OPEN ↓

10249859